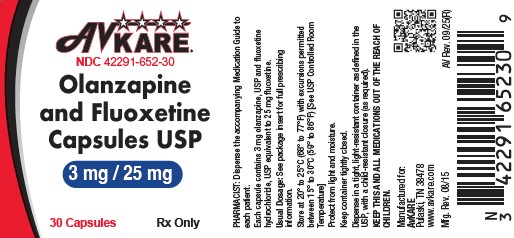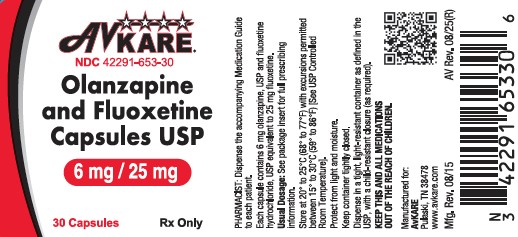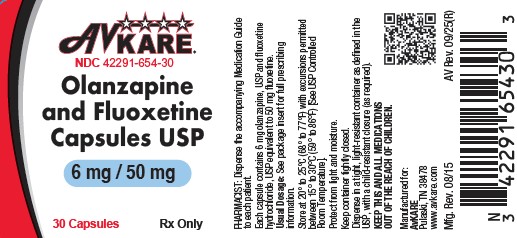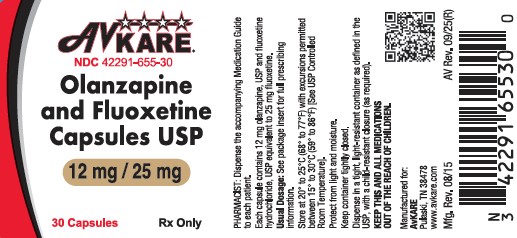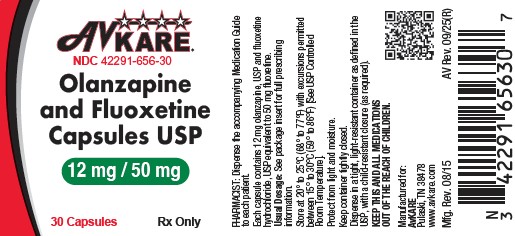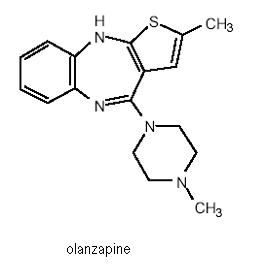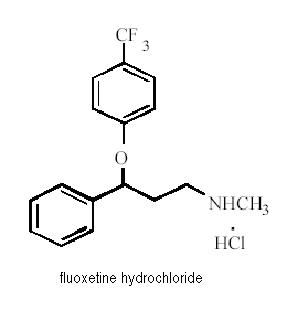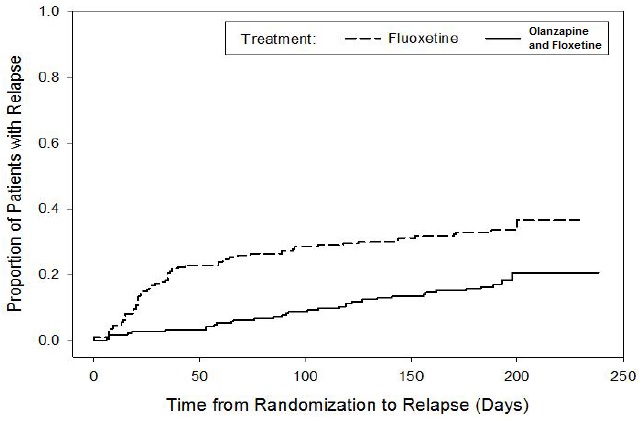 DRUG LABEL: Olanzapine and Fluoxetine
NDC: 42291-652 | Form: CAPSULE
Manufacturer: AvKARE
Category: prescription | Type: HUMAN PRESCRIPTION DRUG LABEL
Date: 20251015

ACTIVE INGREDIENTS: OLANZAPINE 3 mg/1 1; FLUOXETINE HYDROCHLORIDE 25 mg/1 1
INACTIVE INGREDIENTS: D&C YELLOW NO. 10; FD&C BLUE NO. 1; FD&C BLUE NO. 2; INDIGOTINDISULFONATE SODIUM; FD&C RED NO. 40; GELATIN, UNSPECIFIED; FERROSOFERRIC OXIDE; MAGNESIUM STEARATE; STARCH, CORN; PROPYLENE GLYCOL; SHELLAC; TITANIUM DIOXIDE; FD&C YELLOW NO. 6

HIGHLIGHTS OF PRESCRIBING INFORMATION

Olanzapine and Fluoxetine Capsules USP
Rx Only
These highlights do not include all the information needed to use OLANZAPINE AND FLUOXETINE CAPSULES safely and effectively. See full prescribing information for OLANZAPINE AND FLUOXETINE CAPSULES.
OLANZAPINE and FLUOXETINE capsules, for oral use
Initial U.S. Approval: 2003

WARNINGS: SUICIDAL THOUGHTS AND BEHAVIORS; AND INCREASED MORTALITY IN ELDERLY PATIENTS WITH DEMENTIA-RELATED PSYCHOSIS

See full prescribing information for complete boxed warning.

- Increased risk of suicidal thinking and behavior in children, adolescents, and young adults taking antidepressants. Olanzapine and fluoxetine capsules are not approved for use in children less than 10 years of age (5.1, 8.4, 17.2).
- Monitor for worsening and emergence of suicidal thoughts and behaviors (5.1, 17.2).
- Elderly patients with dementia-related psychosis treated with antipsychotic drugs are at an increased risk of death. Olanzapine and fluoxetine capsules are not approved for the treatment of patients with dementia-related psychosis (5.2, 5.21, 17.3).

1 INDICATIONS AND USAGE

Olanzapine and fluoxetine capsules combine olanzapine, an atypical antipsychotic and fluoxetine, a selective serotonin reuptake inhibitor, indicated for treatment of:

- Acute Depressive Episodes Associated with Bipolar I Disorder (1)
- Treatment Resistant Depression (1)

2 DOSAGE AND ADMINISTRATION

- Adult Starting Dose: 6 mg olanzapine with 25 mg fluoxetine (6 mg/25 mg, once daily in the evening) (2.1, 2.2)
- Adult Maximum Dose: 12 mg/50 mg once daily (2.1, 2.2).
- Pediatric Bipolar Depression Starting Dose: 3 mg/25 mg once daily (for ages 10 to 17 years) (2.1).
- Pediatric Bipolar Depression Maximum Dose: 12 mg/50 mg (2.1)
- Starting dose in patients predisposed to hypotensive reactions, hepatic impairment, or with potential for slowed metabolism: 3 mg/25 mg to 6 mg/25 mg. Escalate dose cautiously (2.3)

3 DOSAGE FORMS AND STRENGTHS

- Capsules: 3 mg olanzapine/25 mg fluoxetine, 6 mg olanzapine/25 mg fluoxetine, 6 mg olanzapine/50 mg fluoxetine, 12 mg olanzapine/25 mg fluoxetine, and 12 mg olanzapine/50 mg fluoxetine (mg equivalent olanzapine/mg equivalent fluoxetine) (3)

4 CONTRAINDICATIONS

- Monoamine Oxidase Inhibitors (MAOI): Because of the risk of serotonin syndrome, do not use MAOIs intended to treat psychiatric disorders with olanzapine and fluoxetine capsules or within 5 weeks of stopping treatment with olanzapine and fluoxetine capsules. Do not use olanzapine and fluoxetine capsules within 14 days of stopping an MAOI intended to treat psychiatric disorders. In addition, do not start olanzapine and fluoxetine capsules in a patient who is being treated with linezolid or intravenous methylene blue. (4.1)
- Pimozide: Do not use. Risk of QT interval prolongation (4.2, 5.20, 7.7, 7.8)
- Thioridazine: Do not use. Risk of QT interval prolongation. Do not use thioridazine within 5 weeks of discontinuing olanzapine and fluoxetine capsules (4.2, 5.20, 7.7, 7.8)

5 WARNINGS AND PRECAUTIONS

- Neuroleptic Malignant Syndrome: Manage with immediate discontinuation and close monitoring (5.3)
- Drug Reaction with Eosinophilia and Systemic Symptoms (DRESS): Discontinue if DRESS is suspected (5.4)
- Metabolic Changes: Atypical antipsychotic drugs have been associated with metabolic changes including hyperglycemia, dyslipidemia, and weight gain (5.5)
  - Hyperglycemia and Diabetes Mellitus: In some cases extreme and associated with ketoacidosis or hyperosmolar coma or death. Monitor for symptoms of hyperglycemia. Perform fasting blood glucose testing before beginning, and periodically during treatment. (5.5)
  - Dyslipidemia: Appropriate clinical monitoring is recommended, including fasting blood lipid testing before beginning, and periodically during, treatment (5.5)
  - Weight gain: Consider potential consequences of weight gain. Monitor weight regularly (5.5)
- Serotonin Syndrome: Serotonin syndrome has been reported with SSRIs and SNRIs, including olanzapine and fluoxetine capsules, both when taken alone, but especially when co-administered with other serotonergic agents (including triptans, tricyclic antidepressants, fentanyl, lithium, tramadol, tryptophan, buspirone, amphetamines, and St. John's Wort). If such symptoms occur, discontinue olanzapine and fluoxetine capsules and initiate supportive treatment. If concomitant use of olanzapine and fluoxetine capsules with other serotonergic drugs is clinically warranted, patients should be made aware of a potential increased risk for serotonin syndrome, particularly during treatment initiation and dose increases (5.6)
- Angle-Closure Glaucoma: Angle-closure glaucoma has occurred in patients with untreated anatomically narrow angles treated with antidepressants (5.7)
- Allergic Reactions and Rash: Discontinue upon appearance of rash or allergic phenomena (5.8)
- Activation of Mania/Hypomania: Screen for Bipolar Disorder and monitor for activation of mania/hypomania (5.9)
- Tardive Dyskinesia: Discontinue if clinically appropriate (5.10)
- Orthostatic Hypotension: Can be associated with bradycardia and syncope. Risk is increased during initial dose titration. Use caution in patients with cardiovascular disease or cerebrovascular disease, and those conditions that could affect hemodynamic responses (5.11)
- Leukopenia, Neutropenia, and Agranulocytosis: Has been reported with antipsychotics, including olanzapine and fluoxetine capsules. Patients with a history of a clinically significant low white blood cell count (WBC) or drug induced leukopenia/neutropenia should have their complete blood count (CBC) monitored frequently during the first few months of therapy. Consider discontinuing olanzapine and fluoxetine capsules at the first sign of a clinically significant decline in WBC in the absence of other causative factors (5.13)
- Seizures: Use cautiously in patients with a history of seizures or with conditions that lower the seizure threshold (5.15)
- Abnormal Bleeding: SSRIs increase the risk of bleeding. Use with NSAIDs, aspirin, warfarin, or other drugs that affect coagulation may potentiate the risk of gastrointestinal or other bleeding (5.16)
- Hyponatremia: Can occur in association with syndrome of inappropriate antidiuretic hormone (SIADH). Consider discontinuing olanzapine and fluoxetine capsules if symptomatic hyponatremia occurs (SIADH) (5.17)
- Potential for Cognitive and Motor Impairment: Has potential to impair judgment, thinking, and motor skills. Caution patients about operating machinery (5.18)
- QT Prolongation: QT prolongation and ventricular arrhythmia including Torsade de Pointes have been reported with fluoxetine. Use with caution in conditions that predispose to arrhythmias or increased fluoxetine exposure. Use cautiously in patients with risk factors for QT prolongation (4.2, 5.20)
- Hyperprolactinemia: May elevate prolactin levels (5.22)
- Long Elimination Half-Life of Fluoxetine: Changes in dose will not be fully reflected in plasma for several weeks (5.24)

6 ADVERSE REACTIONS

Most common adverse reactions (≥5% and at least twice that for placebo) in adults: sedation, weight increased, appetite increased, dry mouth, fatigue, edema, tremor, disturbance in attention, blurred vision.

Children and adolescents: sedation, weight increased, appetite increased, tremor, triglyceride increased, hepatic enzymes increased (6.1)

To report SUSPECTED ADVERSE REACTIONS, contact AvKARE, Inc. at 1-855-361-3993 or FDA at 1-800-FDA-1088 or www.fda.gov/medwatch.

7 DRUG INTERACTIONS

- Monoamine Oxidase Inhibitor (MAOI): (2.4, 2.5, 4.1, 5.6, 7.1)
- Drugs Metabolized by CYP2D6: Fluoxetine is a potent inhibitor of CYP2D6 enzyme pathway (7.7)
- Tricyclic Antidepressants (TCAs): Monitor TCA levels during coadministration with olanzapine and fluoxetine capsules or when olanzapine and fluoxetine capsules have been recently discontinued (5.6, 7.7)
- CNS Acting Drugs: Caution is advised if the concomitant administration of olanzapine and fluoxetine capsules and other CNS-active drugs is required (7.2)
- Antihypertensive Agent: Enhanced antihypertensive effect (7.7)
- Levodopa and Dopamine Agonists: May antagonize levodopa/dopamine agonists (7.7)
- Benzodiazepines: May potentiate orthostatic hypotension and sedation (7.6, 7.7)
- Clozapine: May elevate clozapine levels (7.7)
- Haloperidol: Elevated haloperidol levels have been observed (7.7)
- Carbamazepine: Potential for elevated carbamazepine levels and clinical anticonvulsant toxicity (7.7)
- Phenytoin: Potential for elevated phenytoin levels and clinical anticonvulsant toxicity (7.7)
- Alcohol: May potentiate sedation and orthostatic hypotension (7.7)
- Serotonergic Drugs: (2.4, 2.5, 4.1, 5.6, 7.3)
- Fluvoxamine: May increase olanzapine levels; a lower dose of the olanzapine component of olanzapine and fluoxetine capsules should be considered (7.6)
- Drugs that Interfere with Hemostasis: (e.g., NSAIDs, Aspirin, Warfarin, etc.): May potentiate the risk of bleeding (7.4)
- Drugs Tightly Bound to Plasma Proteins: Fluoxetine may cause shift in plasma concentrations (7.7)
- Drugs that Prolong the QT Interval: Do not use olanzapine and fluoxetine capsules in combination with thioridazine or pimozide. Use olanzapine and fluoxetine capsules with caution in combination with other drugs that prolong the QT interval (4.2, 5.20, 7.7, 7.8)

8 USE IN SPECIFIC POPULATIONS

- Pregnancy: Olanzapine and fluoxetine capsules should be used during pregnancy only if the potential benefit justifies the potential risk to the fetus (8.1)
- Nursing Mothers: Breast feeding is not recommended (8.3)
- Pediatric Use: Safety and efficacy of olanzapine and fluoxetine capsules for the treatment of bipolar I depression in patients under 10 years of age have not been established. Safety and efficacy of olanzapine and fluoxetine capsules for treatment resistant depression in patients under 18 years of age have not been established (8.4)
- Hepatic Impairment: Use a lower or less frequent dose in patients with cirrhosis (8.6)

FULL PRESCRIBING INFORMATION

WARNINGS: SUICIDAL THOUGHTS AND BEHAVIORS; AND INCREASED MORTALITY IN ELDERLY PATIENTS WITH DEMENTIA-RELATED PSYCHOSIS

Suicidal Thoughts and Behaviors — Antidepressants increased the risk of suicidal thoughts and behavior in children, adolescents, and young adults in short-term studies. These studies did not show an increase in the risk of suicidal thoughts and behavior with antidepressant use in patients over age 24; there was a reduction in risk with antidepressant use in patients aged 65 and older.

In patients of all ages who are started on antidepressant therapy, monitor closely for worsening and emergence of suicidal thoughts and behaviors. Advise families and caregivers of the need for close observation and communication with the prescriber. Olanzapine and fluoxetine capsules are not approved for use in children less than 10 years of age [see Warnings and Precautions (5.1), Use in Specific Populations (8.4), and Patient Counseling Information (17.2)].

Increased Mortality in Elderly Patients with Dementia-Related Psychosis — Elderly patients with dementia-related psychosis treated with antipsychotic drugs are at an increased risk of death. Olanzapine and fluoxetine capsules are not approved for the treatment of patients with dementia-related psychosis [see Warnings and Precautions (5.2)].

1 INDICATIONS AND USAGE

Olanzapine and fluoxetine capsules are indicated for the treatment of:

- Acute depressive episodes in Bipolar I Disorder [see Clinical Studies (14.1)].
- Treatment resistant depression (Major Depressive Disorder in patient who do not respond to 2 separate trials of different antidepressants of adequate dose and duration in the current episode) [see Clinical Studies (14.2)].

2 DOSAGE AND ADMINISTRATION

2.1 Depressive Episodes Associated with Bipolar I Disorder

Adults – Administer olanzapine and fluoxetine capsules once daily in the evening, generally beginning with the 6 mg/25 mg (mg olanzapine/mg equivalent fluoxetine) capsule. While food has no appreciable effect on the absorption of olanzapine and fluoxetine given individually, the effect of food on the absorption of olanzapine and fluoxetine capsules has not been studied. Make dosage adjustments, if indicated, according to efficacy and tolerability. Antidepressant efficacy was demonstrated with olanzapine and fluoxetine capsules in a dose range of olanzapine 6 mg to 12 mg and fluoxetine 25 mg to 50 mg [see Clinical Studies (14.1)]. The safety of doses above 18 mg of olanzapine and 75 mg of fluoxetine has not been evaluated in adult clinical studies. Periodically reexamine the need for continued pharmacotherapy.

Children and Adolescents (10 to 17 years of age) — Administer olanzapine and fluoxetine capsules once daily in the evening, generally beginning with the 3 mg/25 mg capsule, without regard to meals, with a recommended target dose within the approved dosing range (6/25; 6/50; 12/25; 12/50 mg) [see Clinical Studies ((14.1)]. The safety of doses above 12 mg of olanzapine and 50 mg of fluoxetine has not been evaluated in pediatric clinical studies. Periodically reexamine the need for continued pharmacotherapy.

2.2 Treatment Resistant Depression

Administer olanzapine and fluoxetine capsules once daily in the evening, generally beginning with the 6 mg/25 mg capsule. While food has no appreciable effect on the absorption of olanzapine and fluoxetine given individually, the effect of food on the absorption of olanzapine and fluoxetine capsules has not been studied. Adjust dosage, if indicated, according to efficacy and tolerability. Antidepressant efficacy was demonstrated with olanzapine and fluoxetine capsules in a dose range of olanzapine 6 mg to 18 mg and fluoxetine 25 mg to 50 mg [see Clinical Studies (14.2)]. The safety of doses above 18 mg/75 mg has not been evaluated in clinical studies. Periodically reexamine the need for continued pharmacotherapy.

2.3 Specific Populations

Start olanzapine and fluoxetine capsules at 3 mg/25 mg or 6 mg/25 mg in patients with a predisposition to hypotensive reactions, patients with hepatic impairment, or patients who exhibit a combination of factors that may slow the metabolism of olanzapine and fluoxetine capsules (female gender, geriatric age, nonsmoking status) or those patients who may be pharmacodynamically sensitive to olanzapine. Titrate slowly and adjust dosage as needed in patients who exhibit a combination of factors that may slow metabolism. Olanzapine and fluoxetine capsules have not been systematically studied in patients >65 years of age or in patients <10 years of age [see Warnings and Precautions (5.21), Use in Specific Populations (8.5), and Clinical Pharmacology (12.3, 12.4)].

Treatment of Pregnant Women — When treating pregnant women with fluoxetine, a component of olanzapine and fluoxetine capsules, the physician should carefully consider the potential risks and potential benefits of treatment. Neonates exposed to SSRIs or SNRIs late in the third trimester have developed complications requiring prolonged hospitalizations, respiratory support, and tube feeding [see Use in Specific Populations (8.1)].

2.4 Switching a Patient To or From a Monoamine Oxidase Inhibitor (MAOI) Intended to Treat Psychiatric Disorders

At least 14 days should elapse between discontinuation of an MAOI intended to treat psychiatric disorders and initiation of therapy with olanzapine and fluoxetine capsules. Conversely, at least 5 weeks should be allowed after stopping olanzapine and fluoxetine capsules before starting an MAOI intended to treat psychiatric disorders [see Contraindications (4.1)].

2.5 Use of Olanzapine and Fluoxetine Capsules with Other MAOIs such as Linezolid or Methylene Blue

Do not start olanzapine and fluoxetine capsules in a patient who is being treated with linezolid or intravenous methylene blue because there is an increased risk of serotonin syndrome. In a patient who requires more urgent treatment of a psychiatric condition, other interventions, including hospitalization, should be considered [see Contraindications (4.1)].

In some cases, a patient already receiving olanzapine and fluoxetine capsule therapy may require urgent treatment with linezolid or intravenous methylene blue. If acceptable alternatives to linezolid or intravenous methylene blue treatment are not available and the potential benefits of linezolid or intravenous methylene blue are judged to outweigh the risks of serotonin syndrome in a particular patient, olanzapine and fluoxetine capsules should be stopped promptly, and linezolid or intravenous methylene blue can be administered. The patient should be monitored for symptoms of serotonin syndrome for five weeks or until 24 hours after the last dose of linezolid or intravenous methylene blue, whichever comes first. Therapy with olanzapine and fluoxetine capsules may be resumed 24 hours after the last dose of linezolid or intravenous methylene blue [see Warnings and Precautions (5.6)].

The risk of administering methylene blue by non-intravenous routes (such as oral tablets or by local injection) or in intravenous doses much lower than 1 mg/kg with olanzapine and fluoxetine capsules is unclear. The clinician should, nevertheless, be aware of the possibility of emergent symptoms of serotonin syndrome with such use [see Warnings and Precautions (5.6)].

2.6 Discontinuation of Treatment with Olanzapine and Fluoxetine Capsules

Symptoms associated with discontinuation of fluoxetine, a component of olanzapine and fluoxetine capsules, SNRIs, and SSRIs, have been reported [see Warnings and Precautions (5.25)].

3 DOSAGE FORMS AND STRENGTHS

Capsules (mg olanzapine, USP/mg equivalent fluoxetine):

- 3 mg/25 mg
- 6 mg/25 mg
- 6 mg/50 mg
- 12 mg/25 mg
- 12 mg/50 mg

4 CONTRAINDICATIONS

4.1 Monoamine Oxidase Inhibitors (MAOIs)

The use of MAOIs intended to treat psychiatric disorders with olanzapine and fluoxetine capsules or within 5 weeks of stopping treatment with olanzapine and fluoxetine capsules is contraindicated because of an increased risk of serotonin syndrome. The use of olanzapine and fluoxetine capsules within 14 days of stopping an MAOI intended to treat psychiatric disorders is also contraindicated [see Dosage and Administration (2.4) and Warnings and Precautions (5.6)].

Starting olanzapine and fluoxetine capsules in a patient who is being treated with MAOIs such as linezolid or intravenous methylene blue is also contraindicated because of an increased risk of serotonin syndrome [see Dosage and Administration (2.5)and Warnings and Precautions (5.6)].

4.2 Other Contraindications

- Pimozide [see Warnings and Precautions (5.20) and Drug Interactions (7.7, 7.8)]
- Thioridazine [see Warnings and Precautions (5.20) and Drug Interactions (7.7, 7.8)]

Pimozide and thioridazine prolong the QT interval. Olanzapine and fluoxetine capsules can increase the levels of pimozide and thioridazine through inhibition of CYP2D6. Olanzapine and fluoxetine capsules can also prolong the QT interval.

5 WARNINGS AND PRECAUTIONS

5.1 Suicidal Thoughts and Behaviors in Children, Adolescents, and Young Adults

Patients with Major Depressive Disorder (MDD), both adult and pediatric, may experience worsening of their depression and/or the emergence of suicidal ideation and behavior (suicidality) or unusual changes in behavior, whether or not they are taking antidepressant medications, and this risk may persist until significant remission occurs. Suicide is a known risk of depression and certain other psychiatric disorders, and these disorders themselves are the strongest predictors of suicide. There has been a long-standing concern, however, that antidepressants may have a role in inducing worsening of depression and the emergence of suicidality in certain patients during the early phases of treatment. Pooled analyses of short-term placebo-controlled trials of antidepressant drugs (SSRIs and others) showed that these drugs increase the risk of suicidal thinking and behavior (suicidality) in children, adolescents, and young adults (ages 18 to 24) with Major Depressive Disorder (MDD) and other psychiatric disorders. Short-term studies did not show an increase in the risk of suicidality with antidepressants compared to placebo in adults beyond age 24; there was a reduction with antidepressants compared to placebo in adults aged 65 and older.

The pooled analyses of placebo-controlled trials in children and adolescents with MDD, Obsessive Compulsive Disorder (OCD), or other psychiatric disorders included a total of 24 short-term trials of 9 antidepressant drugs in over 4400 patients. The pooled analyses of placebo-controlled trials in adults with MDD or other psychiatric disorders included a total of 295 short-term trials (median duration of 2 months) of 11 antidepressant drugs in over 77,000 patients. There was considerable variation in risk of suicidality among drugs, but a tendency toward an increase in the younger patients for almost all drugs studied. There were differences in absolute risk of suicidality across the different indications, with the highest incidence in MDD. The risk differences (drug versus placebo), however, were relatively stable within age strata and across indications. These risk differences (drug-placebo difference in the number of cases of suicidality per 1000 patients treated) are provided in Table 1.

Table 1: Suicidality per 1000 Patients Treated
Age Range | Drug-Placebo Difference in Number of Cases of Suicidality per 1000 Patients Treated
 | Increases Compared to Placebo
<18 | 14 additional cases
18 to 24 | 5 additional cases
 | Decreases Compared to Placebo
25 to 64 | 1 fewer case
≥65 | 6 fewer cases

No suicides occurred in any of the pediatric trials. There were suicides in the adult trials, but the number was not sufficient to reach any conclusion about drug effect on suicide.

It is unknown whether the suicidality risk extends to longer-term use, i.e., beyond several months. However, there is substantial evidence from placebo-controlled maintenance trials in adults with depression that the use of antidepressants can delay the recurrence of depression.

All patients being treated with antidepressants for any indication should be monitored appropriately and observed closely for clinical worsening, suicidality, and unusual changes in behavior, especially during the initial few months of a course of drug therapy, or at times of dose changes, either increases or decreases.

The following symptoms, anxiety, agitation, panic attacks, insomnia, irritability, hostility, aggressiveness, impulsivity, akathisia (psychomotor restlessness), hypomania, and mania, have been reported in adult and pediatric patients being treated with antidepressants for Major Depressive Disorder as well as for other indications, both psychiatric and nonpsychiatric. Although a causal link between the emergence of such symptoms and either the worsening of depression and/or the emergence of suicidal impulses has not been established, there is concern that such symptoms may represent precursors to emerging suicidality.

Consideration should be given to changing the therapeutic regimen, including possibly discontinuing the medication, in patients whose depression is persistently worse, or who are experiencing emergent suicidality or symptoms that might be precursors to worsening depression or suicidality, especially if these symptoms are severe, abrupt in onset, or were not part of the patient’s presenting symptoms.

If the decision has been made to discontinue treatment, medication should be tapered, as rapidly as is feasible, but with recognition that abrupt discontinuation can be associated with certain symptoms [ see Warnings and Precautions (5.25)].

Families and caregivers of patients being treated with antidepressants for Major Depressive Disorder or other indications, both psychiatric and nonpsychiatric, should be alerted about the need to monitor patients for the emergence of agitation, irritability, unusual changes in behavior, and the other symptoms described above, as well as the emergence of suicidality, and to report such symptoms immediately to health care providers. Such monitoring should include daily observation by families and caregivers. Prescriptions for olanzapine and fluoxetine capsules should be written for the smallest quantity of capsules consistent with good patient management, in order to reduce the risk of overdose.

It should be noted that olanzapine and fluoxetine capsules are not approved for use in treating any indications in patients less than 10 years of age [ see Use in Specific Populations (8.4) ].

5.2 Increased Mortality in Elderly Patients with Dementia-Related Psychosis

Elderly patients with dementia-related psychosis treated with antipsychotic drugs are at an increased risk of death. Olanzapine and fluoxetine capsules are not approved for the treatment of patients with dementia-related psychosis [ see Boxed Warning, Warnings and Precautions (5.21), and Patient Counseling Information (17.3) ].

In olanzapine placebo-controlled clinical trials of elderly patients with dementia-related psychosis, the incidence of death in olanzapine-treated patients was significantly greater than placebo-treated patients (3.5% vs 1.5%, respectively).

Meta-Analysis of Antipsychotic Use in Dementia-Related Psychosis – Elderly patients with dementia-related psychosis treated with antipsychotic drugs are at an increased risk of death. Analyses of seventeen placebo-controlled trials (modal duration of 10 weeks), largely in patients taking atypical antipsychotic drugs, revealed a risk of death in drug-treated patients of between 1.6 to 1.7 times the risk of death in placebo-treated patients. Over the course of a typical 10 week controlled trial, the rate of death in drug-treated patients was about 4.5%, compared to a rate of about 2.6% in the placebo group. Although the causes of death were varied, most of the deaths appeared to be either cardiovascular (e.g., heart failure, sudden death) or infectious (e.g., pneumonia) in nature. Observational studies suggest that, similar to atypical antipsychotic drugs, treatment with conventional antipsychotic drugs may increase mortality. The extent to which the findings of increased mortality in observational studies may be attributed to the antipsychotic drug as opposed to some characteristic(s) of the patients is not clear. Olanzapine and fluoxetine capsules are not approved for the treatment of patients with dementia-related psychosis [ see Warnings and Precautions (5.21) and Patient Counseling Information (17.3) ].

Cerebrovascular Adverse Events (CVAE), Including Stroke — Cerebrovascular adverse events (e.g., stroke, transient ischemic attack), including fatalities, were reported in patients in trials of olanzapine in elderly patients with dementia-related psychosis. In placebo-controlled trials, there was a significantly higher incidence of cerebrovascular adverse events in patients treated with olanzapine compared to patients treated with placebo. Olanzapine and olanzapine and fluoxetine capsules are not approved for the treatment of patients with dementia-related psychosis [ see Boxed Warning and Patient Counseling Information (17.3) ].

5.3 Neuroleptic Malignant Syndrome (NMS)

A potentially fatal symptom complex sometimes referred to as NMS has been reported in association with administration of antipsychotic drugs, including olanzapine. Clinical manifestations of NMS are hyperpyrexia, muscle rigidity, altered mental status, and evidence of autonomic instability (irregular pulse or blood pressure, tachycardia, diaphoresis, and cardiac dysrhythmia). Additional signs may include elevated creatinine phosphokinase, myoglobinuria (rhabdomyolysis), and acute renal failure.

The diagnostic evaluation of patients with this syndrome is complicated. In arriving at a diagnosis, it is important to exclude cases where the clinical presentation includes both serious medical illness (e.g., pneumonia, systemic infection, etc.) and untreated or inadequately treated extrapyramidal signs and symptoms (EPS). Other important considerations in the differential diagnosis include central anticholinergic toxicity, heat stroke, drug fever, and primary central nervous system pathology.

The management of NMS should include: 1) immediate discontinuation of antipsychotic drugs and other drugs not essential to concurrent therapy, 2) intensive symptomatic treatment and medical monitoring, and 3) treatment of any concomitant serious medical problems for which specific treatments are available. There is no general agreement about specific pharmacological treatment regimens for NMS.

If after recovering from NMS, a patient requires treatment with an antipsychotic, the patient should be carefully monitored, since recurrences of NMS have been reported [ see Warnings and Precautions (5.5) and Patient Counseling Information (17.4, 17.9) ].

5.4 Drug Reaction with Eosinophilia and Systemic Symptoms (DRESS)

Drug Reaction with Eosinophilia and Systemic Symptoms (DRESS) has been reported with olanzapine exposure. DRESS may present with a cutaneous reaction (such as rash or exfoliative dermatitis), eosinophilia, fever, and/or lymphadenopathy with systemic complications such as hepatitis, nephritis, pneumonitis, myocarditis, and/or pericarditis. DRESS is sometimes fatal. Discontinue olanzapine and fluoxetine capsules if DRESS is suspected [see Patient Counseling Information (17.5)].

5.5 Metabolic Changes

Atypical antipsychotic drugs have been associated with metabolic changes including hyperglycemia, dyslipidemia, and weight gain. Metabolic changes may be associated with increased cardiovascular/cerebrovascular risk. Olanzapine’s specific metabolic profile is presented below.

Hyperglycemia and Diabetes Mellitus

Adults — Physicians should consider the risks and benefits when prescribing olanzapine and fluoxetine capsules to patients with an established diagnosis of diabetes mellitus, or having borderline increased blood glucose level (fasting 100 to 126 mg/dL, nonfasting 140 to 200 mg/dL). Patients taking olanzapine and fluoxetine capsules should be monitored regularly for worsening of glucose control. Patients starting treatment with olanzapine and fluoxetine capsules should undergo fasting blood glucose testing at the beginning of treatment and periodically during treatment. Any patient treated with atypical antipsychotics should be monitored for symptoms of hyperglycemia including polydipsia, polyuria, polyphagia, and weakness. Patients who develop symptoms of hyperglycemia during treatment with atypical antipsychotics should undergo fasting blood glucose testing. In some cases, hyperglycemia has resolved when the atypical antipsychotic was discontinued; however, some patients required continuation of anti-diabetic treatment despite discontinuation of the suspect drug [see Patient Counseling Information (17.6)].

Hyperglycemia, in some cases extreme and associated with ketoacidosis or hyperosmolar coma or death, has been reported in patients treated with atypical antipsychotics, including olanzapine alone, as well as olanzapine taken concomitantly with fluoxetine. Assessment of the relationship between atypical antipsychotic use and glucose abnormalities is complicated by the possibility of an increased background risk of diabetes mellitus in patients with schizophrenia and the increasing incidence of diabetes mellitus in the general population. Epidemiological studies suggest an increased risk of treatment-emergent hyperglycemia-related adverse reactions in patients treated with the atypical antipsychotics. While relative risk estimates are inconsistent, the association between atypical antipsychotics and increases in glucose levels appears to fall on a continuum and olanzapine appears to have a greater association than some other atypical antipsychotics.

Mean increases in blood glucose have been observed in patients treated (median exposure of 9.2 months) with olanzapine in phase 1 of the Clinical Antipsychotic Trials of Intervention Effectiveness (CATIE). The mean increase of serum glucose (fasting and nonfasting samples) from baseline to the average of the 2 highest serum concentrations was 15.0 mg/dL.

In a study of healthy volunteers, subjects who received olanzapine (N=22) for 3 weeks had a mean increase compared to baseline in fasting blood glucose of 2.3 mg/dL. Placebo-treated subjects (N=19) had a mean increase in fasting blood glucose compared to baseline of 0.34 mg/dL.

In an analysis of 7 controlled clinical studies, 2 of which were placebo-controlled, with treatment duration up to 12 weeks, olanzapine and fluoxetine capsules were associated with a greater mean change in random glucose compared to placebo (+8.65 mg/dL vs -3.86 mg/dL). The difference in mean changes between olanzapine and fluoxetine capsules and placebo was greater in patients with evidence of glucose dysregulation at baseline (including those patients diagnosed with diabetes mellitus or related adverse reactions, patients treated with anti-diabetic agents, patients with a baseline random glucose level ≥200 mg/dL, or a baseline fasting glucose level ≥126 mg/dL). Olanzapine and fluoxetine capsule-treated patients had a greater mean HbA1c increase from baseline of 0.15% (median exposure 63 days), compared to a mean HbA1c decrease of 0.04% in fluoxetine-treated subjects (median exposure 57 days) and a mean HbA1c increase of 0.12% in olanzapine-treated patients (median exposure 56 days).

In an analysis of 6 controlled clinical studies, a larger proportion of olanzapine and fluoxetine capsule-treated subjects had glycosuria (4.4%) compared to placebo-treated subjects (1.4%).

The mean change in nonfasting glucose in patients exposed at least 48 weeks was +5.9 mg/dL (N=425).

Table 2 shows short-term and long-term changes in random glucose levels from adult olanzapine and fluoxetine capsule studies.

Table 2: Changes in Random Glucose Levels from Adult Olanzapine and Fluoxetine Capsule Studies
Laboratory Analyte | Category Change (at least once) from Baseline | Treatment Arm | Up to 12 weeks exposure |  | At least 48 weeks exposure
Laboratory Analyte | Category Change (at least once) from Baseline | Treatment Arm | N | Patients | N | Patients
Random Glucose | Normal to High (<140 mg/dL to ≥200 mg/dL) | Olanzapine and Fluoxetine Capsules | 609 | 2.3% | 382 | 3.1%
Random Glucose | Normal to High (<140 mg/dL to ≥200 mg/dL) | Placebo | 346 | 0.3% | NAa | NAa
Random Glucose | Borderline to High (≥140 mg/dL and <200 mg/dL to ≥200 mg/dL) | Olanzapine and Fluoxetine Capsules | 44 | 34.1% | 27 | 37.0%
Random Glucose | Borderline to High (≥140 mg/dL and <200 mg/dL to ≥200 mg/dL) | Placebo | 28 | 3.6% | NAa | NAa

a Not Applicable.

In a 47 week olanzapine and fluoxetine capsule study, the mean change from baseline to endpoint in fasting glucose was +4.81 mg/dL (n=130). Table 3 shows the categorical changes in fasting glucose [see Clinical Studies (14.2)].

Table 3: Changes in Fasting Glucose Levels from a Single Adult Olanzapine and Fluoxetine Capsule Study
 |  |  | Up to 27 Weeks Exposure (Randomized, Double-Blind Phase) |  | Up to 47 Weeks Exposure
Laboratory Analyte | Category Change (at least once) from Baseline | Treatment Arm | N | Patients | N | Patients
Fasting Glucose | Normal to High (<100 mg/dL to ≥126 mg/dL) | Olanzapine and Fluoxetine Capsules | 90 | 4.4% | 130 | 11.5%
Fasting Glucose | Normal to High (<100 mg/dL to ≥126 mg/dL) | Fluoxetine | 96 | 5.2% | NAa | NAa
Fasting Glucose | Borderline to High (≥100 mg/dL and <126 mg/dL to ≥126 mg/dL) | Olanzapine and Fluoxetine Capsules | 98 | 18.4% | 79 | 32.9%
Fasting Glucose | Borderline to High (≥100 mg/dL and <126 mg/dL to ≥126 mg/dL) | Fluoxetine | 97 | 7.2% | NAa | NAa

a Not Applicable.

Controlled fasting glucose data is limited for olanzapine and fluoxetine capsules; however, in an analysis of 5 placebo-controlled olanzapine monotherapy studies with treatment duration up to 12 weeks, olanzapine was associated with a greater mean change in fasting glucose levels compared to placebo (+2.76 mg/dL vs +0.17 mg/dL).

The mean change in fasting glucose for olanzapine-treated patients exposed at least 48 weeks was +4.2 mg/dL (N=487). In analyses of patients who completed 9 to 12 months of olanzapine therapy, mean change in fasting and nonfasting glucose levels continued to increase over time.

Children and Adolescents — In a single, 8 week, randomized, placebo-controlled clinical trial investigating olanzapine and fluoxetine capsules for treatment of bipolar I depression in patients 10 to 17 years of age, there were no clinically meaningful differences observed between olanzapine and fluoxetine capsules and placebo for mean change in fasting glucose levels. Table 4 shows categorical changes in fasting blood glucose from the pediatric olanzapine and fluoxetine capsules study.

Table 4: Changes in Fasting Glucose Levels from a Single Pediatric Olanzapine and Fluoxetine Capsule Study in Bipolar Depression

Laboratory Analyte | Category Change (at least once) from Baseline | Treatment Arm | Up to 8 weeks exposure
Laboratory Analyte | Category Change (at least once) from Baseline | Treatment Arm | N | Patients
Fasting Glucose | Normal to High (<100 mg/dL to ≥126 mg/dL) | Olanzapine and Fluoxetine Capsules | 125 | 4.8%
Fasting Glucose | Normal to High (<100 mg/dL to ≥126 mg/dL) | Placebo | 65 | 1.5%
Fasting Glucose | Normal/IGTa to High (<126 mg/dL to ≥126 mg/dL) | Olanzapine and Fluoxetine Capsules | 156 | 5.8%
Fasting Glucose | Normal/IGTa to High (<126 mg/dL to ≥126 mg/dL) | Placebo | 78 | 1.3%
Fasting Glucose | Normal/IGT (<126 mg/dL) to ≥140 mg/dL) | Olanzapine and Fluoxetine Capsules | 156 | 1.9%
Fasting Glucose | Normal/IGT (<126 mg/dL) to ≥140 mg/dL) | Placebo | 78 | 0.0%

a Impaired Glucose Tolerance.

Olanzapine Monotherapy in Adolescents — In an analysis of 3 placebo-controlled olanzapine monotherapy studies of adolescent patients, including those with Schizophrenia (6 weeks) or Bipolar I Disorder (manic or mixed episodes) (3 weeks), olanzapine was associated with a greater mean change from baseline in fasting glucose levels compared to placebo (+2.68 mg/dL vs -2.59 mg/dL). The mean change in fasting glucose for adolescents exposed at least 24 weeks was +3.1 mg/dL (N=121). Table 5 shows short-term and long-term changes in fasting blood glucose from adolescent olanzapine monotherapy studies.

Table 5: Changes in Fasting Glucose Levels from Adolescent Olanzapine Monotherapy Studies
Laboratory Analyte | Category Change (at least once) from Baseline | Treatment Arm | Up to 12 weeks exposure |  | At least 24 weeks exposure
Laboratory Analyte | Category Change (at least once) from Baseline | Treatment Arm | N | Patients | N | Patients
Fasting Glucose | Normal to High (<100 mg/dL to ≥126 mg/dL) | Olanzapine | 124 | 0% | 108 | 0.9%
Fasting Glucose | Normal to High (<100 mg/dL to ≥126 mg/dL) | Placebo | 53 | 1.9% | NAa | NAa
Fasting Glucose | Borderline to High (≥100 mg/dL and <126 mg/dL to ≥126 mg/dL) | Olanzapine | 14 | 14.3% | 13 | 23.1%
Fasting Glucose | Borderline to High (≥100 mg/dL and <126 mg/dL to ≥126 mg/dL) | Placebo | 13 | 0% | NAa | NAa

a Not Applicable.

Dyslipidemia

Undesirable alterations in lipids have been observed with olanzapine and fluoxetine capsule use. Clinical monitoring, including baseline and periodic follow-up lipid evaluations in patients using olanzapine and fluoxetine capsules, is recommended [see Patient Counseling Information (17.7)].

Adults — Clinically meaningful, and sometimes very high (>500 mg/dL), elevations in triglyceride levels have been observed with olanzapine and fluoxetine capsule use. Clinically meaningful increases in total cholesterol have also been seen with olanzapine and fluoxetine capsule use.

In an analysis of 7 controlled clinical studies, 2 of which were placebo-controlled, with treatment duration up to 12 weeks, olanzapine and fluoxetine capsule-treated patients had an increase from baseline in mean random total cholesterol of 12.1 mg/dL compared to an increase from baseline in mean random total cholesterol of 4.8 mg/dL for olanzapine-treated patients and a decrease in mean random total cholesterol of 5.5 mg/dL for placebo-treated patients. Table 6 shows categorical changes in nonfasting lipid values.

In long-term olanzapine and fluoxetine in combination studies (at least 48 weeks), changes (at least once) in nonfasting total cholesterol from normal at baseline to high occurred in 12% (N=150) and changes from borderline to high occurred in 56.6% (N=143) of patients. The mean change in nonfasting total cholesterol was 11.3 mg/dL (N=426).

Table 6: Changes in Nonfasting Lipids Values from Controlled Clinical Studies with Treatment Duration up to 12 Weeks
Laboratory Analyte | Category Change (at least once) from Baseline | Treatment Arm | N | Patients
Nonfasting Triglycerides | Increase by ≥50 mg/dL | OFC | 174 | 67.8%
Nonfasting Triglycerides | Increase by ≥50 mg/dL | Olanzapine | 172 | 72.7%
Nonfasting Triglycerides | Normal to High (<150 mg/dL to ≥500 mg/dL) | OFC | 57 | 0%
Nonfasting Triglycerides | Normal to High (<150 mg/dL to ≥500 mg/dL) | Olanzapine | 58 | 0%
Nonfasting Triglycerides | Borderline to High (≥150 mg/dL and <500 mg/dL to ≥500 mg/dL) | OFC | 106 | 15.1%
Nonfasting Triglycerides | Borderline to High (≥150 mg/dL and <500 mg/dL to ≥500 mg/dL) | Olanzapine | 103 | 8.7%
Nonfasting Total Cholesterol | Increase by ≥40 mg/dL | OFC | 685 | 35%
Nonfasting Total Cholesterol | Increase by ≥40 mg/dL | Olanzapine | 749 | 22.7%
Nonfasting Total Cholesterol | Increase by ≥40 mg/dL | Placebo | 390 | 9%
Nonfasting Total Cholesterol | Normal to High (<200 mg/dL to ≥240 mg/dL) | OFC | 256 | 8.2%
Nonfasting Total Cholesterol | Normal to High (<200 mg/dL to ≥240 mg/dL) | Olanzapine | 279 | 2.9%
Nonfasting Total Cholesterol | Normal to High (<200 mg/dL to ≥240 mg/dL) | Placebo | 175 | 1.7%
Nonfasting Total Cholesterol | Borderline to High (≥200 mg/dL and <240 mg/dL to ≥240 mg/dL) | OFC | 213 | 36.2%
Nonfasting Total Cholesterol | Borderline to High (≥200 mg/dL and <240 mg/dL to ≥240 mg/dL) | Olanzapine | 261 | 27.6%
Nonfasting Total Cholesterol | Borderline to High (≥200 mg/dL and <240 mg/dL to ≥240 mg/dL) | Placebo | 111 | 9.9%

A 47 week olanzapine and fluoxetine capsule study demonstrated mean changes from baseline to endpoint in fasting total cholesterol (+1.24 mg/dL), LDL cholesterol (+0.29 mg/dL), direct HDL cholesterol (-2.13 mg/dL), and triglycerides (+11.33 mg/dL). Table 7 shows the categorical changes in fasting lipids [see Clinical Studies (14.2)].

Table 7: Changes in Fasting Lipids Values from a Controlled Study with Olanzapine and Fluoxetine Capsule Treatment Duration up to 47 Weeks
 |  |  | Up to 27 Weeks Treatment (Randomized, Double-Blind Phase) |  | Up to 47 Weeks Treatment
Laboratory Analyte | Category Change (at least once) from Baseline | Treatment Arm | N | Patients | N | Patients
Fasting Total Cholesterol | Normal to High (<200 mg/dL to ≥240 mg/dL) | Olanzapine and Fluoxetine Capsules | 47 | 2.1% | 83 | 19.3%
Fasting Total Cholesterol | Normal to High (<200 mg/dL to ≥240 mg/dL) | Fluoxetine | 59 | 3.4% | NAa | NAa
Fasting Total Cholesterol | Borderline to High (≥200 and <240 mg/dL to ≥240 mg/dL) | Olanzapine and Fluoxetine Capsules | 75 | 28.0% | 73 | 69.9%
Fasting Total Cholesterol | Borderline to High (≥200 and <240 mg/dL to ≥240 mg/dL) | Fluoxetine | 83 | 20.5% | NAa | NAa
Fasting LDL Cholesterol | Normal to High (<100 mg/dL to ≥160 mg/dL) | Olanzapine and Fluoxetine Capsules | 22 | 4.5% | 46 | 8.7%
Fasting LDL Cholesterol | Normal to High (<100 mg/dL to ≥160 mg/dL) | Fluoxetine | 26 | 0% | NAa | NAa
Fasting LDL Cholesterol | Borderline to High (≥100 mg/dL and <160 mg/dL to ≥160 mg/dL) | Olanzapine and Fluoxetine Capsules | 115 | 17.4% | 128 | 46.9%
Fasting LDL Cholesterol | Borderline to High (≥100 mg/dL and <160 mg/dL to ≥160 mg/dL) | Fluoxetine | 134 | 10.4% | NAa | NAa
Fasting HDL Cholesterol | Normal to Low (≥40 mg/dL to <40 mg/dL) | Olanzapine and Fluoxetine Capsules | 199 | 39.2% | 193 | 45.1%
Fasting HDL Cholesterol | Normal to Low (≥40 mg/dL to <40 mg/dL) | Fluoxetine | 208 | 25.5% | NAa | NAa
Fasting Triglycerides | Normal to High (<150 mg/dL to ≥200 mg/dL) | Olanzapine and Fluoxetine Capsules | 68 | 16.2% | 115 | 46.1%
Fasting Triglycerides | Normal to High (<150 mg/dL to ≥200 mg/dL) | Fluoxetine | 74 | 5.4% | NAa | NAa
Fasting Triglycerides | Borderline to High (≥150 mg/dL and <200 mg/dL to ≥200 mg/dL) | Olanzapine and Fluoxetine Capsules | 47 | 51.1% | 40 | 72.5%
Fasting Triglycerides | Borderline to High (≥150 mg/dL and <200 mg/dL to ≥200 mg/dL) | Fluoxetine | 41 | 26.8% | NAa | NAa

a Not Applicable.

Fasting lipid data is limited for olanzapine and fluoxetine capsules; however, in an analysis of 5 placebo-controlled olanzapine monotherapy studies with treatment duration up to 12 weeks, olanzapine-treated patients had increases from baseline in mean fasting total cholesterol, LDL cholesterol, and triglycerides of 5.3 mg/dL, 3.0 mg/dL, and 20.8 mg/dL respectively compared to decreases from baseline in mean fasting total cholesterol, LDL cholesterol, and triglycerides of 6.1 mg/dL, 4.3 mg/dL, and 10.7 mg/dL for placebo-treated patients. For fasting HDL cholesterol, no clinically meaningful differences were observed between olanzapine-treated patients and placebo-treated patients. Mean increases in fasting lipid values (total cholesterol, LDL cholesterol, and triglycerides) were greater in patients without evidence of lipid dysregulation at baseline, where lipid dysregulation was defined as patients diagnosed with dyslipidemia or related adverse reactions, patients treated with lipid lowering agents, patients with high baseline lipid levels.

In long-term olanzapine studies (at least 48 weeks), patients had increases from baseline in mean fasting total cholesterol, LDL cholesterol, and triglycerides of 5.6 mg/dL, 2.5 mg/dL, and 18.7 mg/dL, respectively, and a mean decrease in fasting HDL cholesterol of 0.16 mg/dL. In an analysis of patients who completed 12 months of therapy, the mean nonfasting total cholesterol did not increase further after approximately 4 to 6 months.

The proportion of olanzapine-treated patients who had changes (at least once) in total cholesterol, LDL cholesterol or triglycerides from normal or borderline to high, or changes in HDL cholesterol from normal or borderline to low, was greater in long-term studies (at least 48 weeks) as compared with short-term studies. Table 8 shows categorical changes in fasting lipids values.

Table 8: Changes in Fasting Lipids Values from Adult Olanzapine Monotherapy Studies
Laboratory Analyte | Category Change (at least once) from Baseline | Treatment Arm | Up to 12 weeks exposure |  | At least 48 weeks exposure
Laboratory Analyte | Category Change (at least once) from Baseline | Treatment Arm | N | Patients | N | Patients
Fasting; Triglycerides | Increase by ≥50 mg/dL | Olanzapine | 745 | 39.6% | 487 | 61.4%
Fasting; Triglycerides | Increase by ≥50 mg/dL | Placebo | 402 | 26.1% | NAa | NAa
Fasting; Triglycerides | Normal to High; (<150 mg/dL to ≥200 mg/dL) | Olanzapine | 457 | 9.2% | 293 | 32.4%
Fasting; Triglycerides | Normal to High; (<150 mg/dL to ≥200 mg/dL) | Placebo | 251 | 4.4% | NAa | NAa
Fasting; Triglycerides | Borderline to High; (≥150 mg/dL and <200 mg/dL to ≥200 mg/dL) | Olanzapine | 135 | 39.3% | 75 | 70.7%
Fasting; Triglycerides | Borderline to High; (≥150 mg/dL and <200 mg/dL to ≥200 mg/dL) | Placebo | 65 | 20.0% | NAa | NAa
Fasting; Triglycerides
Fasting; Total Cholesterol | Increase by ≥40 mg/dL | Olanzapine | 745 | 21.6% | 489 | 32.9%
Fasting; Total Cholesterol | Increase by ≥40 mg/dL | Placebo | 402 | 9.5% | NAa | NAa
Fasting; Total Cholesterol | Normal to High; (<200 mg/dL to ≥240 mg/dL) | Olanzapine | 392 | 2.8% | 283 | 14.8%
Fasting; Total Cholesterol | Normal to High; (<200 mg/dL to ≥240 mg/dL) | Placebo | 207 | 2.4% | NAa | NAa
Fasting; Total Cholesterol | Borderline to High; (≥200 mg/dL and <240 mg/dL to ≥240 mg/dL) | Olanzapine | 222 | 23.0% | 125 | 55.2%
Fasting; Total Cholesterol | Borderline to High; (≥200 mg/dL and <240 mg/dL to ≥240 mg/dL) | Placebo | 112 | 12.5% | NAa | NAa
Fasting; Total Cholesterol
Fasting; LDL Cholesterol | Increase by ≥30 mg/dL | Olanzapine | 536 | 23.7% | 483 | 39.8%
Fasting; LDL Cholesterol | Increase by ≥30 mg/dL | Placebo | 304 | 14.1% | NAa | NAa
Fasting; LDL Cholesterol | Normal to High; (<100 mg/dL to ≥160 mg/dL) | Olanzapine | 154 | 0% | 123 | 7.3%
Fasting; LDL Cholesterol | Normal to High; (<100 mg/dL to ≥160 mg/dL) | Placebo | 82 | 1.2% | NAa | NAa
Fasting; LDL Cholesterol | Borderline to High; (≥100 mg/dL and <160 mg/dL to ≥160 mg/dL) | Olanzapine | 302 | 10.6% | 284 | 31.0%
Fasting; LDL Cholesterol | Borderline to High; (≥100 mg/dL and <160 mg/dL to ≥160 mg/dL) | Placebo | 173 | 8.1% | NAa | NAa

a Not Applicable.

In phase 1 of the Clinical Antipsychotic Trials of Intervention Effectiveness (CATIE), over a median exposure of 9.2 months, the mean increase in triglycerides in patients taking olanzapine was 40.5 mg/dL. In phase 1 of CATIE, the median increase in total cholesterol was 9.4 mg/dL.

Children and Adolescents — In a single, 8 week, randomized, placebo-controlled clinical trial investigating olanzapine and fluoxetine capsules for treatment of bipolar I depression in patients 10 to 17 years of age, there were clinically meaningful and statistically significant differences observed between olanzapine and fluoxetine capsules and placebo for mean change in fasting total cholesterol (+16.3 mg/dL vs. -4.3 mg/dL, respectively), LDL cholesterol (+9.7 mg/dL vs -3.5 mg/dL, respectively), and triglycerides (+35.4 mg/dL vs. -3.5 mg/dL, respectively).

The magnitude and frequency of changes in lipids were greater in children and adolescents than previously observed in adults. Table 9 shows categorical changes in fasting lipids values from the pediatric olanzapine and fluoxetine capsules study.

Table 9: Changes in Fasting Lipids Values from a Single Pediatric Olanzapine and Fluoxetine Capsule Study in Bipolar Depression
Laboratory Analyte | Category Change (at least once) from Baseline | Treatment Arm | Up to 8 weeks exposure
Laboratory Analyte | Category Change (at least once) from Baseline | Treatment Arm | N | Patients
Fasting; Triglycerides | Increase by ≥50 mg/dL | OFC | 158 | 70.3%
Fasting; Triglycerides | Increase by ≥50 mg/dL | Placebo | 81 | 38.3%
Fasting; Triglycerides | Normal to High; (<90 mg/dL to ≥130 mg/dL) | OFC | 71 | 39.4%
Fasting; Triglycerides | Normal to High; (<90 mg/dL to ≥130 mg/dL) | Placebo | 31 | 19.4%
Fasting; Triglycerides | Borderline to High; (≥90 mg/dL and <130 mg/dL to ≥130 mg/dL) | OFC | 13 | 84.6%
Fasting; Triglycerides | Borderline to High; (≥90 mg/dL and <130 mg/dL to ≥130 mg/dL) | Placebo | 12 | 33.3%
Fasting; Triglycerides | Normal/borderline to High; (<130 mg/dL to ≥130 mg/dL) | OFC | 106 | 52.8%
Fasting; Triglycerides | Normal/borderline to High; (<130 mg/dL to ≥130 mg/dL) | Placebo | 56 | 25.0%
Fasting; Triglycerides | Normal to borderline/high; (<90 mg/dL to ≥90 mg/dL) | OFC | 71 | 73.2%
Fasting; Triglycerides | Normal to borderline/high; (<90 mg/dL to ≥90 mg/dL) | Placebo | 31 | 41.9%
Fasting; Triglycerides | Normal/borderline/high to very high; (<500 mg/dL to ≥500 mg/dL) | OFC | 158 | 2.5%
Fasting; Triglycerides | Normal/borderline/high to very high; (<500 mg/dL to ≥500 mg/dL) | Placebo | 81 | 1.2%
Fasting; Total Cholesterol | Increase by ≥40 mg/dL | OFC | 158 | 52.5%
Fasting; Total Cholesterol | Increase by ≥40 mg/dL | Placebo | 81 | 8.6%
Fasting; Total Cholesterol | Normal to High; (<170 mg/dL to ≥200 mg/dL) | OFC | 81 | 12.3%
Fasting; Total Cholesterol | Normal to High; (<170 mg/dL to ≥200 mg/dL) | Placebo | 44 | 4.5%
Fasting; Total Cholesterol | Borderline to High; (≥170 mg/dL and <200 mg/dL to ≥200 mg/dL) | OFC | 22 | 72.7%
Fasting; Total Cholesterol | Borderline to High; (≥170 mg/dL and <200 mg/dL to ≥200 mg/dL) | Placebo | 11 | 24.3%
Fasting; Total Cholesterol | Normal/borderline to High (<200 mg/dL to ≥200 mg/dL) | OFC | 126 | 32.5%
Fasting; Total Cholesterol | Normal/borderline to High (<200 mg/dL to ≥200 mg/dL) | Placebo | 67 | 10.4%
Fasting; Total Cholesterol | Normal to borderline/high (<170 mg/dL to ≥170 mg/dL) | OFC | 81 | 58.0%
Fasting; Total Cholesterol | Normal to borderline/high (<170 mg/dL to ≥170 mg/dL) | Placebo | 44 | 31.8%
Fasting; LDL Cholesterol | Increase by ≥30 mg/dL | OFC | 158 | 53.8%
Fasting; LDL Cholesterol | Increase by ≥30 mg/dL | Placebo | 81 | 23.5%
Fasting; LDL Cholesterol | Normal to High; (<110 mg/dL to ≥130 mg/dL) | OFC | 112 | 13.4%
Fasting; LDL Cholesterol | Normal to High; (<110 mg/dL to ≥130 mg/dL) | Placebo | 62 | 6.5%
Fasting; LDL Cholesterol | Borderline to High; (≥110 mg/dL and <130 mg/dL to ≥130 mg/dL) | OFC | 12 | 75.0%
Fasting; LDL Cholesterol | Borderline to High; (≥110 mg/dL and <130 mg/dL to ≥130 mg/dL) | Placebo | 3 | 0.0%
Fasting; LDL Cholesterol | Normal/borderline to High; (<130 mg/dL to ≥130 mg/dL) | OFC | 138 | 21.7%
Fasting; LDL Cholesterol | Normal/borderline to High; (<130 mg/dL to ≥130 mg/dL) | Placebo | 77 | 7.8%
Fasting; LDL Cholesterol | Normal to borderline/high; (<110 mg/dL to ≥110 mg/dL) | OFC | 112 | 30.4%
Fasting; LDL Cholesterol | Normal to borderline/high; (<110 mg/dL to ≥110 mg/dL) | Placebo | 62 | 14.5%

Olanzapine Monotherapy in Adolescents — In an analysis of 3 placebo-controlled olanzapine monotherapy studies of adolescents, including those with Schizophrenia (6 weeks) or Bipolar I Disorder (manic or mixed episodes) (3 weeks), olanzapine-treated adolescents had increases from baseline in mean fasting total cholesterol, LDL cholesterol, and triglycerides of 12.9 mg/dL, 6.5 mg/dL, and 28.4 mg/dL, respectively, compared to increases from baseline in mean fasting total cholesterol and LDL cholesterol of 1.3 mg/dL and 1.0 mg/dL, and a decrease in triglycerides of 1.1 mg/dL for placebo-treated adolescents. For fasting HDL cholesterol, no clinically meaningful differences were observed between olanzapine-treated adolescents and placebo-treated adolescents.

In long-term olanzapine studies (at least 24 weeks), adolescents had increases from baseline in mean fasting total cholesterol, LDL cholesterol, and triglycerides of 5.5 mg/dL, 5.4 mg/dL, and 20.5 mg/dL, respectively, and a mean decrease in fasting HDL cholesterol of 4.5 mg/dL. Table 10 shows categorical changes in fasting lipids values in adolescents.

Table 10: Changes in Fasting Lipids Values from Adolescent Olanzapine Monotherapy Studies
Laboratory Analyte | Category Change (at least once) from Baseline | Treatment Arm | Up to 6 weeks exposure |  | At least 24 weeks exposure
Laboratory Analyte | Category Change (at least once) from Baseline | Treatment Arm | N | Patients | N | Patients
Fasting Triglycerides | Increase by ≥50 mg/dL | Olanzapine | 138 | 37.0% | 122 | 45.9%
Fasting Triglycerides | Increase by ≥50 mg/dL | Placebo | 66 | 15.2% | NAa | NAa
Fasting Triglycerides | Normal to High; (<90 mg/dL to >130 mg/dL) | Olanzapine | 67 | 26.9% | 66 | 36.4%
Fasting Triglycerides | Normal to High; (<90 mg/dL to >130 mg/dL) | Placebo | 28 | 10.7% | NAa | NAa
Fasting Triglycerides | Borderline to High; (≥90 mg/dL and ≤130 mg/dL to >130 mg/dL) | Olanzapine | 37 | 59.5% | 31 | 64.5%
Fasting Triglycerides | Borderline to High; (≥90 mg/dL and ≤130 mg/dL to >130 mg/dL) | Placebo | 17 | 35.3% | NAa | NAa
Fasting Total Cholesterol | Increase by ≥40 mg/dL | Olanzapine | 138 | 14.5% | 122 | 14.8%
Fasting Total Cholesterol | Increase by ≥40 mg/dL | Placebo | 66 | 4.5% | NAa | NAa
Fasting Total Cholesterol | Normal to High; (<170 mg/dL to ≥200 mg/dL) | Olanzapine | 87 | 6.9% | 78 | 7.7%
Fasting Total Cholesterol | Normal to High; (<170 mg/dL to ≥200 mg/dL) | Placebo | 43 | 2.3% | NAa | NAa
Fasting Total Cholesterol | Borderline to High; (≥170 mg/dL and <200 mg/dL to ≥200 mg/dL) | Olanzapine | 36 | 38.9% | 33 | 57.6%
Fasting Total Cholesterol | Borderline to High; (≥170 mg/dL and <200 mg/dL to ≥200 mg/dL) | Placebo | 13 | 7.7% | NAa | NAa
Fasting LDL Cholesterol | Increase by ≥30 mg/dL | Olanzapine | 137 | 17.5% | 121 | 22.3%
Fasting LDL Cholesterol | Increase by ≥30 mg/dL | Placebo | 63 | 11.1% | NAa | NAa
Fasting LDL Cholesterol | Normal to High; (<110 mg/dL to ≥130 mg/dL) | Olanzapine | 98 | 5.1% | 92 | 10.9%
Fasting LDL Cholesterol | Normal to High; (<110 mg/dL to ≥130 mg/dL) | Placebo | 44 | 4.5% | NAa | NAa
Fasting LDL Cholesterol | Borderline to High; (≥110 mg/dL and <130 mg/dL to ≥130 mg/dL) | Olanzapine | 29 | 48.3% | 21 | 47.6%
Fasting LDL Cholesterol | Borderline to High; (≥110 mg/dL and <130 mg/dL to ≥130 mg/dL) | Placebo | 9 | 0% | NAa | NAa

a Not Applicable.

Weight Gain

Potential consequences of weight gain should be considered prior to starting olanzapine and fluoxetine capsules. Patients receiving olanzapine and fluoxetine capsules should receive regular monitoring of weight [ see Patient Counseling Information (17.8)].

Adults — In an analysis of 7 controlled clinical studies, 2 of which were placebo-controlled, the mean weight increase for olanzapine and fluoxetine capsule-treated patients was greater than placebo-treated patients [4 kg (8.8 lb) vs -0.3 kg (-0.7 lb)]. Twenty-two percent of olanzapine and fluoxetine capsule-treated patients gained at least 7% of their baseline weight, with a median exposure to event of 6 weeks. This was greater than in placebo-treated patients (1.8%). Approximately 3% of olanzapine and fluoxetine capsule-treated patients gained at least 15% of their baseline weight, with a median exposure to event of 8 weeks. This was greater than in placebo-treated patients (0%). Clinically significant weight gain was observed across all baseline Body Mass Index (BMI) categories. Discontinuation due to weight gain occurred in 2.5% of olanzapine and fluoxetine capsule-treated patients and 0% of placebo-treated patients.

In long-term olanzapine and fluoxetine in combination studies (at least 48 weeks), the mean weight gain was 6.7 kg (14.7 lb) (median exposure of 448 days, N=431). The percentages of patients who gained at least 7%, 15% or 25% of their baseline body weight with long-term exposure were 66%, 33%, and 10%, respectively. Discontinuation due to weight gain occurred in 1.2% of patients treated with olanzapine and fluoxetine in combination following at least 48 weeks of exposure.

Table 11 presents the distribution of weight gain in a single long-term relapse prevention study of patients treated for up to 47 weeks with olanzapine and fluoxetine [see Clinical Studies (14.2)].

Table 11: Weight Gain with Olanzapine and Fluoxetine Use in a Single Relapse Prevention Study in Adults
Amount Gained kg; (lb) | Up to 8 Weeks; (N=881); (%) | Up to 20 Weeks; (N=651); (%) | Up to 47 Weeks; (N=220); (%)
≤0 | 19.8 | 14.9 | 19.1
0 to ≤5 (0 to 11 lb) | 64.1 | 47.2 | 37.7
>5 to ≤10 (11 to 22 lb) | 15.1 | 30.3 | 27.7
>10 to ≤15 (22 to 33 lb) | 0.9 | 5.8 | 10.0
>15 to ≤20 (33 to 44 lb) | 0.1 | 1.2 | 3.2
>20 to ≤25 (44 to 55 lb) | 0.0 | 0.6 | 1.4
>25 to ≤30 (55 to 66 lb) | 0.0 | 0.0 | 0.5
>30 (>66 lb) | 0.0 | 0.0 | 0.5

In long-term olanzapine studies (at least 48 weeks), the mean weight gain was 5.6 kg (12.3 lb) (median exposure of 573 days, N=2021). The percentages of patients who gained at least 7%, 15%, or 25% of their baseline body weight with long-term exposure were 64%, 32%, and 12%, respectively. Discontinuation due to weight gain occurred in 0.4% of olanzapine-treated patients following at least 48 weeks of exposure.

Table 12 includes data on adult weight gain with olanzapine pooled from 86 clinical trials. The data in each column represent data for those patients who completed treatment periods of the durations specified.

Table 12: Weight Gain with Olanzapine Use in Adults
Amount Gained; kg (lb) | 6 Weeks (N=7465) (%) | 6 Months (N=4162) (%) | 12 Months (N=1345) (%) | 24 Months (N=474) (%) | 36 Months (N=147) (%)
≤0 | 26.2 | 24.3 | 20.8 | 23.2 | 17.0
0 to ≤5; (0 to 11 lb) | 57.0 | 36.0 | 26.0 | 23.4 | 25.2
>5 to ≤10; (11 to 22 lb) | 14.9 | 24.6 | 24.2 | 24.1 | 18.4
>10 to ≤15; (22 to 33 lb) | 1.8 | 10.9 | 14.9 | 11.4 | 17.0
>15 to ≤20; (33 to 44 lb) | 0.1 | 3.1 | 8.6 | 9.3 | 11.6
>20 to ≤25; (44 to 55 lb) | 0 | 0.9 | 3.3 | 5.1 | 4.1
>25 to ≤30; (55 to 66 lb) | 0 | 0.2 | 1.4 | 2.3 | 4.8
>30; (>66 lb) | 0 | 0.1 | 0.8 | 1.2 | 2

Dose group differences with respect to weight gain have been observed. In a single 8 week randomized, double-blind, fixed-dose study comparing 10 (N=199), 20 (N=200) and 40 (N=200) mg/day of oral olanzapine in adult patients with schizophrenia or schizoaffective disorder, mean baseline to endpoint increase in weight (10 mg/day: 1.9 kg; 20 mg/day: 2.3 kg; 40 mg/day: 3 kg) was observed with significant differences between 10 vs 40 mg/day.

Children and Adolescents — In a single, 8 week, randomized, placebo-controlled clinical trial investigating olanzapine and fluoxetine capsules for the treatment of bipolar I depression in patients 10 to 17 years of age, olanzapine and fluoxetine capsules were associated with greater mean change in weight compared to placebo (+4.4 kg vs +0.5 kg, respectively). The percentages of children and adolescents who gained at least 7%, 15%, or 25% of their baseline body weight with 8 week exposure were 52%, 14%, and 1%, respectively. The proportion of patients who had clinically significant weight gain was greater in children and adolescent patients compared to short-term data in adults. Discontinuation due to weight gain occurred in 2.9% of olanzapine and fluoxetine capsule-treated patients and 0% of placebo-treated patients. Table 13 depicts weight gain observed in the pediatric olanzapine and fluoxetine capsule study.

Table 13: Weight Gain with OFC Use Seen in a Single Pediatric Study in Bipolar Depression
Amount Gained; kg (lb) | Up to 8 Weeks; (N=170); (%)
≤0 | 7.1
0 to ≤5 (0 to 11 lb) | 54.7
>5 to ≤10 (11 to 22 lb) | 31.2
>10 to ≤15 (22 to 33 lb) | 7.1
>15 to ≤20 (33 to 44 lb) | 0
>20 to ≤25 (44 to 55 lb) | 0
>25 to ≤30 (55 to 66 lb) | 0
>30 (>66 lb) | 0

Olanzapine Monotherapy in Adolescents — Mean increase in weight in adolescents was greater than in adults. In 4 placebo-controlled trials, discontinuation due to weight gain occurred in 1% of olanzapine-treated patients, compared to 0% of placebo-treated patients.

Table 14: Weight Gain with Olanzapine Use in Adolescents from 4 Placebo-Controlled Trials
Mean change in body weight from baseline (median exposure = 3 weeks) | Olanzapine-treated patients | Placebo-treated patients
Mean change in body weight from baseline (median exposure = 3 weeks) | 4.6 kg (10.1 lb) | 0.3 kg (0.7 lb)
Percentage of patients who gained at least 7% of baseline body weight | 40.6%; (median exposure to 7% = 4 weeks) | 9.8%; (median exposure to 7% = 8 weeks)
Percentage of patients who gained at least 15% of baseline body weight | 7.1%; (median exposure to 15% = 19 weeks) | 2.7%; (median exposure to 15% = 8 weeks)

In long-term olanzapine studies (at least 24 weeks), the mean weight gain was 11.2 kg (24.6 lb) (median exposure of 201 days, N=179). The percentages of adolescents who gained at least 7%, 15%, or 25% of their baseline body weight with long-term exposure were 89%, 55%, and 29%, respectively. Among adolescent patients, mean weight gain by baseline BMI category was 11.5 kg (25.3 lb), 12.1 kg (26.6 lb), and 12.7 kg (27.9 lb), respectively, for normal (N=106), overweight (N=26) and obese (N=17). Discontinuation due to weight gain occurred in 2.2% of olanzapine-treated patients following at least 24 weeks of exposure.

Table 15 shows data on adolescent weight gain with olanzapine pooled from 6 clinical trials. The data in each column represent data for those patients who completed treatment periods of the durations specified. Little clinical trial data is available on weight gain in adolescents with olanzapine beyond 6 months of treatment.

Table 15: Weight Gain with Olanzapine Use in Adolescents
Amount Gained; kg (lb) | 6 Weeks; (N=243); (%) | 6 Months; (N=191); (%)
≤0 | 2.9 | 2.1
0 to ≤5 (0 to 11 lb) | 47.3 | 24.6
>5 to ≤10 (11 to 22 lb) | 42.4 | 26.7
>10 to ≤15 (22 to 33 lb) | 5.8 | 22.0
>15 to ≤20 (33 to 44 lb) | 0.8 | 12.6
>20 to ≤25 (44 to 55 lb) | 0.8 | 9.4
>25 to ≤30 (55 to 66 lb) | 0 | 2.1
>30 to ≤35 (66 to 77 lb) | 0 | 0
>35 to ≤40 (77 to 88 lb) | 0 | 0
>40 (>88 lb) | 0 | 0.5

5.6 Serotonin Syndrome

The development of a potentially life-threatening serotonin syndrome has been reported with SNRIs and SSRIs, including olanzapine and fluoxetine capsules, alone but particularly with concomitant use of other serotonergic drugs (including triptans, tricyclic antidepressants, fentanyl, lithium, tramadol, tryptophan, buspirone, amphetamines, and St. John's Wort) and with drugs that impair metabolism of serotonin (in particular, MAOIs, both those intended to treat psychiatric disorders and also others, such as linezolid and intravenous methylene blue).

Serotonin syndrome symptoms may include mental status changes (e.g., agitation, hallucinations, delirium, and coma), autonomic instability (e.g., tachycardia, labile blood pressure, dizziness, diaphoresis, flushing, hyperthermia), neuromuscular symptoms (e.g., tremor, rigidity, myoclonus, hyperreflexia, incoordination), seizures, and/or gastrointestinal symptoms (e.g., nausea, vomiting, diarrhea). Patients should be monitored for the emergence of serotonin syndrome. Serotonin syndrome symptoms may include mental status changes (e.g., agitation, hallucinations, delirium, and coma), autonomic instability (e.g., tachycardia, labile blood pressure, dizziness, diaphoresis, flushing, hyperthermia), neuromuscular symptoms (e.g., tremor, rigidity, myoclonus, hyperreflexia, incoordination), seizures, and/or gastrointestinal symptoms (e.g., nausea, vomiting, diarrhea). Patients should be monitored for the emergence of serotonin syndrome.

The concomitant use of olanzapine and fluoxetine capsules with MAOIs intended to treat psychiatric disorders is contraindicated. Olanzapine and fluoxetine capsules should also not be started in a patient who is being treated with MAOIs such as linezolid or intravenous methylene blue. All reports with methylene blue that provided information on the route of administration involved intravenous administration in the dose range of 1 mg/kg to 8 mg/kg. No reports involved the administration of methylene blue by other routes (such as oral tablets or local tissue injection) or at lower doses. There may be circumstances when it is necessary to initiate treatment with an MAOI such as linezolid or intravenous methylene blue in a patient taking olanzapine and fluoxetine capsules. Olanzapine and fluoxetine capsules should be discontinued before initiating treatment with the MAOI [ ]. The concomitant use of olanzapine and fluoxetine capsules with MAOIs intended to treat psychiatric disorders is contraindicated. Olanzapine and fluoxetine capsules should also not be started in a patient who is being treated with MAOIs such as linezolid or intravenous methylene blue. All reports with methylene blue that provided information on the route of administration involved intravenous administration in the dose range of 1 mg/kg to 8 mg/kg. No reports involved the administration of methylene blue by other routes (such as oral tablets or local tissue injection) or at lower doses. There may be circumstances when it is necessary to initiate treatment with an MAOI such as linezolid or intravenous methylene blue in a patient taking olanzapine and fluoxetine capsules. Olanzapine and fluoxetine capsules should be discontinued before initiating treatment with the MAOI [ see Dosage and Administration (2.4, 2.5) and Contraindications (4.1) ].

If concomitant use of olanzapine and fluoxetine capsules with other serotonergic drugs including triptans, tricyclic antidepressants, fentanyl, lithium, tramadol, buspirone, tryptophan, amphetamines, and St. John's Wort is clinically warranted, patients should be made aware of a potential increased risk for serotonin syndrome, particularly during treatment initiation and dose increases.

Treatment with olanzapine and fluoxetine capsules and any concomitant serotonergic agents should be discontinued immediately if the above events occur and supportive symptomatic treatment should be initiated.Treatment with olanzapine and fluoxetine capsules and any concomitant serotonergic agents should be discontinued immediately if the above events occur and supportive symptomatic treatment should be initiated.

5.7 Angle-Closure Glaucoma

Angle-Closure Glaucoma — The pupillary dilation that occurs following use of many antidepressant drugs including olanzapine and fluoxetine capsules may trigger an angle-closure attack in a patient with anatomically narrow angles who does not have a patent iridectomy.

5.8 Allergic Reactions and Rash

In olanzapine and fluoxetine capsule premarketing controlled clinical studies, the overall incidence of rash or allergic reactions in olanzapine and fluoxetine capsule-treated patients [4.6% (26/571)] was similar to that of placebo [5.2% (25/477)]. The majority of the cases of rash and/or urticaria were mild; however, 3 patients discontinued (1 due to rash, which was moderate in severity and 2 due to allergic reactions, 1 of which included face edema).

In fluoxetine U.S. clinical studies, 7% of 10,782 fluoxetine-treated patients developed various types of rashes and/or urticaria. Among the cases of rash and/or urticaria reported in premarketing clinical studies, almost a third were withdrawn from treatment because of the rash and/or systemic signs or symptoms associated with the rash. Clinical findings reported in association with rash include fever, leukocytosis, arthralgias, edema, carpal tunnel syndrome, respiratory distress, lymphadenopathy, proteinuria, and mild transaminase elevation. Most patients improved promptly with discontinuation of fluoxetine and/or adjunctive treatment with antihistamines or steroids, and all patients experiencing these reactions were reported to recover completely.

In fluoxetine premarketing clinical studies, 2 patients are known to have developed a serious cutaneous systemic illness. In neither patient was there an unequivocal diagnosis, but 1 was considered to have a leukocytoclastic vasculitis, and the other, a severe desquamating syndrome that was considered variously to be a vasculitis or erythema multiforme. Other patients have had systemic syndromes suggestive of serum sickness.

Since the introduction of fluoxetine, systemic reactions, possibly related to vasculitis, have developed in patients with rash. Although these reactions are rare, they may be serious, involving the lung, kidney, or liver. Death has been reported to occur in association with these systemic reactions.

Anaphylactoid reactions, including bronchospasm, angioedema, and urticaria alone and in combination, have been reported.

Pulmonary reactions, including inflammatory processes of varying histopathology and/or fibrosis, have been reported rarely. These reactions have occurred with dyspnea as the only preceding symptom.

Whether these systemic reactions and rash have a common underlying cause or are due to different etiologies or pathogenic processes is not known. Furthermore, a specific underlying immunologic basis for these reactions has not been identified. Upon the appearance of rash or of other possible allergic phenomena for which an alternative etiology cannot be identified, olanzapine and fluoxetine capsules should be discontinued.

5.9 Activation of Mania/Hypomania

A major depressive episode may be the initial presentation of Bipolar Disorder. It is generally believed (though not established in controlled trials) that treating such an episode with an antidepressant alone may increase the likelihood of precipitation of a manic episode in patients at risk for Bipolar Disorder. Whether any of the symptoms described for clinical worsening and suicide risk represent such a conversion is unknown . However, prior to initiating treatment with an antidepressant, patients with depressive symptoms should be adequately screened to determine if they are at risk for Bipolar Disorder; such screening should include a detailed psychiatric history, including a family history of suicide, Bipolar Disorder, and depression. It should be noted that olanzapine and fluoxetine capsules are approved for the acute treatment of depressive episodes associated with Bipolar I Disorder.

In the 3 controlled bipolar depression studies (2 in adults and 1 in children and adolescents [10 to 17 years of age]) there was no statistically significant difference in the incidence of manic reactions (manic reaction or manic depressive reaction) between olanzapine and fluoxetine capsule- and placebo-treated patients. In 1 adult study, the incidence of manic reactions was (7% [3/43]) in olanzapine and fluoxetine capsule-treated patients compared to (3% [5/184]) in placebo-treated patients. In the other adult study, the incidence of manic reactions was (2% [1/43]) in olanzapine and fluoxetine capsule-treated patients compared to (8% [15/193]) in placebo-treated patients. In a single, 8 week, randomized, placebo-controlled clinical trial investigating olanzapine and fluoxetine capsules for the treatment of bipolar I depression in patients 10 to 17 years of age, the incidence of manic reactions was (1% [2/170]) in olanzapine and fluoxetine capsule-treated patients compared to (0% [0/84]) in placebo-treated patients. Because of the cyclical nature of Bipolar I Disorder, patients should be monitored closely for the development of symptoms of mania/hypomania during treatment with olanzapine and fluoxetine capsules.

5.10 Tardive Dyskinesia

A syndrome of potentially irreversible, involuntary, dyskinetic movements may develop in patients treated with antipsychotic drugs. Although the prevalence of the syndrome appears to be highest among the elderly, especially elderly women, it is impossible to rely upon prevalence estimates to predict, at the inception of antipsychotic treatment, which patients are likely to develop the syndrome. Whether antipsychotic drug products differ in their potential to cause tardive dyskinesia is unknown.

The risk of developing tardive dyskinesia and the likelihood that it will become irreversible are believed to increase as the duration of treatment and the total cumulative dose of antipsychotic drugs administered to the patient increase. However, the syndrome can develop, although much less commonly, after relatively brief treatment periods at low doses or may even arise after discontinuation of treatment.

There is no known treatment for established cases of tardive dyskinesia, although the syndrome may remit, partially or completely, if antipsychotic treatment is withdrawn. Antipsychotic treatment itself, however, may suppress (or partially suppress) the signs and symptoms of the syndrome and thereby may possibly mask the underlying process. The effect that symptomatic suppression has upon the long-term course of the syndrome is unknown.

The incidence of dyskinetic movement in olanzapine and fluoxetine capsule-treated patients was infrequent. The mean score on the Abnormal Involuntary Movement Scale (AIMS) in the olanzapine and fluoxetine capsule-controlled database across clinical studies involving olanzapine and fluoxetine capsule-treated patients decreased from baseline. Nonetheless, olanzapine and fluoxetine capsules should be prescribed in a manner that is most likely to minimize the risk of tardive dyskinesia. If signs and symptoms of tardive dyskinesia appear in a patient on olanzapine and fluoxetine capsules, drug discontinuation should be considered. However, some patients may require treatment with olanzapine and fluoxetine capsules despite the presence of the syndrome. The need for continued treatment should be reassessed periodically.

5.11 Orthostatic Hypotension

Olanzapine and fluoxetine capsules may induce orthostatic hypotension associated with dizziness, tachycardia, bradycardia and, in some patients, syncope, especially during the initial dose-titration period [ see Patient Counseling Information (17.12)].

In the olanzapine and fluoxetine capsule-controlled clinical trials across all indications, there were no significant differences between olanzapine and fluoxetine capsule-treated patients and olanzapine, fluoxetine- or placebo-treated patients in exposure-adjusted rates of orthostatic systolic blood pressure decreases of at least 30 mm Hg. Orthostatic systolic blood pressure decreases of at least 30 mm Hg occurred in 4.0% (28/705), 2.3% (19/831), 4.5% (18/399), and 1.8% (8/442) of the olanzapine and fluoxetine capsules, olanzapine, fluoxetine, and placebo groups, respectively. In this group of studies, the incidence of syncope-related adverse reactions (i.e., syncope and/or loss of consciousness) in olanzapine and fluoxetine capsule-treated patients was 0.4% (3/771) compared to placebo 0.2% (1/477).

In a clinical pharmacology study of olanzapine and fluoxetine capsules, 3 healthy subjects were discontinued from the trial after experiencing severe, but self-limited, hypotension and bradycardia that occurred 2 to 9 hours following a single 12 mg/50 mg dose of olanzapine and fluoxetine capsules. Reactions consisting of this combination of hypotension and bradycardia (and also accompanied by sinus pause) have been observed in at least 3 other healthy subjects treated with various formulations of olanzapine (1 oral, 2 intramuscular). In controlled clinical studies, the incidence of patients with a ≥20 bpm decrease in orthostatic pulse concomitantly with a ≥20 mm Hg decrease in orthostatic systolic blood pressure was 0.3% (2/706) in the olanzapine and fluoxetine capsule group, 0.2% (1/445) in the placebo group, 0.7% (6/837) in the olanzapine group, and 0% (0/404) in the fluoxetine group.

Olanzapine and fluoxetine capsules should be used with particular caution in patients with known cardiovascular disease (history of myocardial infarction or ischemia, heart failure, or conduction abnormalities), cerebrovascular disease, or conditions that would predispose patients to hypotension (dehydration, hypovolemia, and treatment with antihypertensive medications).

5.12 Falls

Olanzapine and fluoxetine capsules may cause somnolence, postural hypotension, motor and sensory instability, which may lead to falls and, consequently, fractures or other injuries. For patients with diseases, conditions, or medications that could exacerbate these effects, complete fall risk assessments when initiating antipsychotic treatment and recurrently for patients on long-term antipsychotic therapy.

5.13 Leukopenia, Neutropenia, and Agranulocytosis

Class Effect — In clinical trial and/or postmarketing experience, events of leukopenia/neutropenia have been reported temporally related to antipsychotic agents, including olanzapine and fluoxetine capsules. Agranulocytosis has also been reported.

Possible risk factors for leukopenia/neutropenia include preexisting low white blood cell count (WBC) and history of drug induced leukopenia/neutropenia. Patients with a history of a clinically significant low WBC or drug induced leukopenia/neutropenia should have their complete blood count (CBC) monitored frequently during the first few months of therapy and discontinuation of olanzapine and fluoxetine capsules should be considered at the first sign of a clinically significant decline in WBC in the absence of other causative factors.

Patients with clinically significant neutropenia should be carefully monitored for fever or other symptoms or signs of infection and treated promptly if such symptoms or signs occur. Patients with severe neutropenia (absolute neutrophil count <1000/mm^3) should discontinue olanzapine and fluoxetine capsules and have their WBC followed until recovery.

5.14 Dysphagia

Esophageal dysmotility and aspiration have been associated with antipsychotic drug use. Aspiration pneumonia is a common cause of morbidity and mortality in patients with advanced Alzheimer’s disease. Olanzapine and fluoxetine capsules are not approved for the treatment of patients with Alzheimer’s disease.

5.15 Seizures

Seizures occurred in 0.2% (4/2547) of olanzapine and fluoxetine capsule-treated patients during open-label clinical studies. No seizures occurred in the controlled olanzapine and fluoxetine capsule studies. Seizures have also been reported with both olanzapine and fluoxetine monotherapy. Olanzapine and fluoxetine capsules should be used cautiously in patients with a history of seizures or with conditions that potentially lower the seizure threshold, e.g., Alzheimer’s dementia. Olanzapine and fluoxetine capsules are not approved for the treatment of patients with Alzheimer’s disease. Conditions that lower the seizure threshold may be more prevalent in a population of ≥65 years of age.

5.16 Abnormal Bleeding

SNRIs and SSRIs, including fluoxetine, may increase the risk of bleeding reactions. Concomitant use of aspirin, non-steroidal anti-inflammatory drugs, warfarin, and other anti-coagulants may add to this risk. Case reports and epidemiological studies (case-control and cohort design) have demonstrated an association between use of drugs that interfere with serotonin reuptake and the occurrence of gastrointestinal bleeding. Bleeding reactions related to SNRIs and SSRIs use have ranged from ecchymoses, hematomas, epistaxis, and petechiae to life-threatening hemorrhages.

Patients should be cautioned about the risk of bleeding associated with the concomitant use of olanzapine and fluoxetine capsules and NSAIDs, aspirin, or other drugs that affect coagulation [ see Drug Interactions (7.4) and Patient Counseling Information (17.13)].

5.17 Hyponatremia

Hyponatremia has been reported during treatment with SNRIs and SSRIs, including fluoxetine and olanzapine and fluoxetine capsules. In many cases, this hyponatremia appears to be the result of the syndrome of inappropriate antidiuretic hormone secretion (SIADH). Cases with serum sodium lower than 110 mmol/L have been reported and appeared to be reversible when [ see Use in Specific Populations (8.5) ] olanzapine and fluoxetine capsules were discontinued. Elderly patients may be at greater risk of developing hyponatremia with SNRIs and SSRIs. Also, patients taking diuretics or who are otherwise volume depleted may be at greater risk. Discontinuation of olanzapine and fluoxetine capsules should be considered in patients with symptomatic hyponatremia and appropriate medical intervention should be instituted.

Signs and symptoms of hyponatremia include headache, difficulty concentrating, memory impairment, confusion, weakness, and unsteadiness, which may lead to falls. More severe and/or acute cases have been associated with hallucination, syncope, seizure, coma, respiratory arrest, and death [ see Patient Counseling Information (17.14)].

5.18 Potential for Cognitive and Motor Impairment

Olanzapine and fluoxetine capsules have the potential to impair judgment, thinking, or motor skills. Patients should be cautioned about operating hazardous machinery, including automobiles, until they are reasonably certain that olanzapine and fluoxetine capsule therapy does not affect them adversely [ see Patient Counseling Information (17.15)].

Adults — Sedation-related adverse reactions were commonly reported with olanzapine and fluoxetine capsule treatment occurring at an incidence of 26.6% in olanzapine and fluoxetine capsule-treated patients compared with 10.9% in placebo-treated patients. Sedation-related adverse reactions (sedation, somnolence, hypersomnia, and lethargy) led to discontinuation in 2% (15/771) of patients in the controlled clinical studies.

Children and Adolescents — In a single, 8 week, randomized, placebo-controlled clinical trial investigating olanzapine and fluoxetine capsules for the treatment of bipolar I depression in patients 10 to 17 years of age, somnolence-related adverse events were commonly reported with olanzapine and fluoxetine capsule treatment occurring at an incidence of 23.5% in olanzapine and fluoxetine capsule-treated patients compared with 2.4% in placebo-treated patients. Somnolence-related adverse events led to discontinuation in 1.2% (2/170) of patients.

5.19 Body Temperature Dysregulation

Disruption of the body’s ability to reduce core body temperature has been attributed to antipsychotic drugs. Appropriate care is advised when prescribing olanzapine and fluoxetine capsules for patients who will be experiencing conditions which may contribute to an elevation in core body temperature (e.g., exercising strenuously, exposure to extreme heat, receiving concomitant medication with anticholinergic activity, or being subject to dehydration) [ see Patient Counseling Information (17.16)].

5.20 QT Prolongation

Post-marketing cases of QT interval prolongation and ventricular arrhythmia including Torsade de Pointes have been reported in patients treated with fluoxetine. Olanzapine and fluoxetine capsules should be used with caution in patients with congenital long QT syndrome; a previous history of QT prolongation; a family history of long QT syndrome or sudden cardiac death; and other conditions that predispose to QT prolongation and ventricular arrhythmia. Such conditions include concomitant use of drugs that prolong the QT interval; hypokalemia or hypomagnesemia; recent myocardial infarction, uncompensated heart failure, bradyarrhythmias, and other significant arrhythmias; and conditions that predispose to increased fluoxetine exposure (overdose, hepatic impairment, use of CYP2D6 inhibitors, CYP2D6 poor metabolizer status, or use of other highly protein-bound drugs). Fluoxetine is primarily metabolized by CYP2D6 [ see Contraindications (4.2), Adverse Reactions (6), Drug Interactions (7.7, 7.8), Overdose (10.1), and Clinical Pharmacology (12.3) ].

Pimozide and thioridazine are contraindicated for use with olanzapine and fluoxetine capsules. Avoid the concomitant use of drugs known to prolong the QT interval. These include specific antipsychotics (e.g., ziprasidone, iloperidone, chlorpromazine, mesoridazine, droperidol); specific antibiotics (e.g., erythromycin, gatifloxacin, moxifloxacin, sparfloxacin); Class 1A antiarrhythmic medications (e.g., quinidine, procainamide); Class III antiarrhythmics (e.g., amiodarone, sotalol); and others (e.g., pentamidine, levomethadyl acetate, methadone, halofantrine, mefloquine, dolasetron mesylate, probucol or tacrolimus) [ see Drug Interactions (7.7, 7.8) and Clinical Pharmacology (12.3) ].

Consider ECG assessment and periodic ECG monitoring if initiating treatment with olanzapine and fluoxetine capsules in patients with risk factors for QT prolongation and ventricular arrhythmia. Consider discontinuing olanzapine and fluoxetine capsules and obtaining a cardiac evaluation if patients develop signs or symptoms consistent with ventricular arrhythmia.

In a single, 8 week, randomized, placebo-controlled clinical trial investigating olanzapine and fluoxetine capsules for the treatment of bipolar I depression in patients 10 to 17 years of age, there was a statistically significant difference in QTc interval for patients treated with olanzapine and fluoxetine capsules compared with patients on placebo: mean change in QTcF (Fridericia correction factor) from baseline to endpoint in patients treated with olanzapine and fluoxetine capsules was 8.2 msec (95% CI 6.2, 10.2). No patient developed QTc increases ≥60 msec or QTc ≥480 msec. Clinicians should use olanzapine and fluoxetine capsules with caution in those children or adolescents who are known to be particularly at risk for QT prolongation [ see Adverse Reactions (6.2) ].

5.21 Antichlolinergic (antimuscarinic) Effects

The following precautions for the individual components may be applicable to olanzapine and fluoxetine capsules.
Olanzapine exhibits in vitro muscarinic receptor affinity. In premarketing clinical studies, olanzapine and fluoxetine capsules were associated with constipation, dry mouth, and tachycardia, all adverse reactions possibly related to cholinergic antagonism. Such adverse reactions were not often the basis for study discontinuations; olanzapine and fluoxetine capsules should be used with caution
in patients with a current diagnosis or prior history of urinary retention, clinically significant

5.22 Hyperprolactinemia

As with other drugs that antagonize dopamine D receptors, olanzapine and fluoxetine capsules elevate prolactin levels, and the elevation persists during administration. Hyperprolactinemia may suppress hypothalamic GnRH, resulting in reduced pituitary gonadotropin secretion. This, in turn, may inhibit reproductive function by impairing gonadal steroidogenesis in both female and male patients. Galactorrhea, amenorrhea, gynecomastia, and erectile dysfunction have been reported in patients receiving prolactin-elevating compounds. Long-standing hyperprolactinemia when associated with hypogonadism may lead to decreased bone density in both female and male subjects. As with other drugs that antagonize dopamine D2 receptors, olanzapine and fluoxetine capsules elevate prolactin levels, and the elevation persists during administration. Hyperprolactinemia may suppress hypothalamic GnRH, resulting in reduced pituitary gonadotropin secretion. This, in turn, may inhibit reproductive function by impairing gonadal steroidogenesis in both female and male patients. Galactorrhea, amenorrhea, gynecomastia, and erectile dysfunction have been reported in patients receiving prolactin-elevating compounds. Long-standing hyperprolactinemia when associated with hypogonadism may lead to decreased bone density in both female and male subjects.

Tissue culture experiments indicate that approximately one-third of human breast cancers are prolactin dependent , a factor of potential importance if the prescription of these drugs is contemplated in a patient with previously detected breast cancer. As is common with compounds that increase prolactin release, an increase in mammary gland neoplasia was observed in the olanzapine carcinogenicity studies conducted in mice and rats [ ]. Neither clinical studies nor epidemiologic studies conducted to date have shown an association between chronic administration of this class of drugs and tumorigenesis in humans; the available evidence is considered too limited to be conclusive at this time. Tissue culture experiments indicate that approximately one-third of human breast cancers are prolactin dependent in vitro, a factor of potential importance if the prescription of these drugs is contemplated in a patient with previously detected breast cancer. As is common with compounds that increase prolactin release, an increase in mammary gland neoplasia was observed in the olanzapine carcinogenicity studies conducted in mice and rats [ see Nonclinical Toxicology (13.1) ]. Neither clinical studies nor epidemiologic studies conducted to date have shown an association between chronic administration of this class of drugs and tumorigenesis in humans; the available evidence is considered too limited to be conclusive at this time.

— In controlled clinical studies of olanzapine and fluoxetine capsules (up to 12 weeks), changes from normal to high in prolactin concentrations were observed in 28% of adults treated with olanzapine and fluoxetine capsules as compared to 5% of placebo-treated patients. The elevations persisted throughout administration of olanzapine and fluoxetine capsules. In a pooled analysis from clinical studies including 2929 adults treated with olanzapine and fluoxetine capsules, potentially associated clinical manifestations included menstrual-related events (1% [20/1946] of females), sexual function-related events (7% [192/2929] of females and males), and breast-related events (0.8% [16/1946] of females, 0.2% [2/983] of males). Adults — In controlled clinical studies of olanzapine and fluoxetine capsules (up to 12 weeks), changes from normal to high in prolactin concentrations were observed in 28% of adults treated with olanzapine and fluoxetine capsules as compared to 5% of placebo-treated patients. The elevations persisted throughout administration of olanzapine and fluoxetine capsules. In a pooled analysis from clinical studies including 2929 adults treated with olanzapine and fluoxetine capsules, potentially associated clinical manifestations included menstrual-related events^1 (1% [20/1946] of females), sexual function-related events^2 (7% [192/2929] of females and males), and breast-related events^3 (0.8% [16/1946] of females, 0.2% [2/983] of males).

— In a single, 8 week, randomized, placebo-controlled clinical trial investigating olanzapine and fluoxetine capsules for the treatment of bipolar I depression in patients 10 to 17 years of age, olanzapine and fluoxetine capsules were associated with a statistically significant greater mean change from baseline in prolactin levels compared to placebo (8.7 mcg/L vs 0.7 mcg/L, respectively). Although prolactin concentrations were very commonly (>10%) elevated above normal in both the olanzapine and fluoxetine capsules and placebo groups, more than twice as many olanzapine and fluoxetine capsule-treated patients were seen with these elevations compared to placebo-treated patients. Five patients experienced an adverse event potentially associated with elevated prolactin; these events included dysmenorrhoea, galactorrhoea, and ovulation disorder. Children and Adolescents — In a single, 8 week, randomized, placebo-controlled clinical trial investigating olanzapine and fluoxetine capsules for the treatment of bipolar I depression in patients 10 to 17 years of age, olanzapine and fluoxetine capsules were associated with a statistically significant greater mean change from baseline in prolactin levels compared to placebo (8.7 mcg/L vs 0.7 mcg/L, respectively). Although prolactin concentrations were very commonly (>10%) elevated above normal in both the olanzapine and fluoxetine capsules and placebo groups, more than twice as many olanzapine and fluoxetine capsule-treated patients were seen with these elevations compared to placebo-treated patients. Five patients experienced an adverse event potentially associated with elevated prolactin; these events included dysmenorrhoea, galactorrhoea, and ovulation disorder.

The magnitude and frequency of change in prolactin in children and adolescents was larger than observed in adult patients treated with olanzapine and fluoxetine capsules, but was similar to that observed in adolescents treated with olanzapine monotherapy.The magnitude and frequency of change in prolactin in children and adolescents was larger than observed in adult patients treated with olanzapine and fluoxetine capsules, but was similar to that observed in adolescents treated with olanzapine monotherapy.

Olanzapine Monotherapy

In placebo-controlled olanzapine clinical studies (up to 12 weeks), changes from normal to high in prolactin concentrations were observed in 30% of adults treated with olanzapine as compared to 10.5% of adults treated with placebo. In a pooled analysis from clinical studies including 8136 adults treated with olanzapine, potentially associated clinical manifestations included menstrual-related events (2% [49/3240] of females), sexual function-related events (2% [150/8136] of females and males), and breast-related events (0.7% [23/3240] of females, 0.2% [9/4896] of males). In placebo-controlled olanzapine clinical studies (up to 12 weeks), changes from normal to high in prolactin concentrations were observed in 30% of adults treated with olanzapine as compared to 10.5% of adults treated with placebo. In a pooled analysis from clinical studies including 8136 adults treated with olanzapine, potentially associated clinical manifestations included menstrual-related events^1 (2% [49/3240] of females), sexual function-related events^2 (2% [150/8136] of females and males), and breast-related events^3 (0.7% [23/3240] of females, 0.2% [9/4896] of males).

In placebo-controlled olanzapine monotherapy studies in adolescent patients (up to 6 weeks) with schizophrenia or bipolar I disorder (manic or mixed episodes), changes from normal to high in prolactin concentrations were observed in 47% of olanzapine-treated patients compared to 7% of placebo-treated patients. In a pooled analysis from clinical trials including 454 adolescents treated with olanzapine, potentially associated clinical manifestations included menstrual-related events (1% [2/168] of females), sexual function-related events (0.7% [3/454] of females and males), and breast-related events (2% [3/168] of females, 2% [7/286] of males) [ ]. In placebo-controlled olanzapine monotherapy studies in adolescent patients (up to 6 weeks) with schizophrenia or bipolar I disorder (manic or mixed episodes), changes from normal to high in prolactin concentrations were observed in 47% of olanzapine-treated patients compared to 7% of placebo-treated patients. In a pooled analysis from clinical trials including 454 adolescents treated with olanzapine, potentially associated clinical manifestations included menstrual-related events^1 (1% [2/168] of females), sexual function-related events^2 (0.7% [3/454] of females and males), and breast-related events^3 (2% [3/168] of females, 2% [7/286] of males) [ see Use in Specific Populations (8.4) ].

Based on a search of the following terms: amenorrhea, hypomenorrhea, menstruation delayed, and oligomenorrhea.^1 Based on a search of the following terms: amenorrhea, hypomenorrhea, menstruation delayed, and oligomenorrhea.

Based on a search of the following terms: anorgasmia, delayed ejaculation, erectile dysfunction, decreased libido, loss of libido, abnormal orgasm, and sexual dysfunction.^2 Based on a search of the following terms: anorgasmia, delayed ejaculation, erectile dysfunction, decreased libido, loss of libido, abnormal orgasm, and sexual dysfunction.

Based on a search of the following terms: breast discharge, enlargement or swelling, galactorrhea, gynecomastia, and lactation disorder.^3 Based on a search of the following terms: breast discharge, enlargement or swelling, galactorrhea, gynecomastia, and lactation disorder.

Dose group differences with respect to prolactin elevation have been observed. In a single 8 week randomized, double-blind, fixed-dose study comparing 10 (n=199), 20 (n=200) and 40 (n=200) mg/day of oral olanzapine in adult patients with schizophrenia or schizoaffective disorder, incidence of prolactin elevation >24.2 ng/mL (female) or >18.77 ng/mL (male) at any time during the trial (10 mg/day: 31.2%; 20 mg/day: 42.7%; 40 mg/day: 61.1%) indicated significant differences between 10 vs 40 mg/day and 20 vs 40 mg/day Dose group differences with respect to prolactin elevation have been observed. In a single 8 week randomized, double-blind, fixed-dose study comparing 10 (n=199), 20 (n=200) and 40 (n=200) mg/day of oral olanzapine in adult patients with schizophrenia or schizoaffective disorder, incidence of prolactin elevation >24.2 ng/mL (female) or >18.77 ng/mL (male) at any time during the trial (10 mg/day: 31.2%; 20 mg/day: 42.7%; 40 mg/day: 61.1%) indicated significant differences between 10 vs 40 mg/day and 20 vs 40 mg/day .

5.23 Concomitant Use of Olanzapine and Fluoxetine Products

Olanzapine and fluoxetine capsules contain the same active ingredients that are in Zyprexa®, Zyprexa® Zydis®, Zyprexa® RelprevvTM (olanzapine), and in Prozac®, Prozac® Weekly™, and Sarafem® (fluoxetine HCl). Caution should be exercised when prescribing these medications concomitantly with olanzapine and fluoxetine capsules [ see Overdosage (10) ].

5.24 Long Elimination Half-Life of Fluoxetine

Because of the long elimination half-lives of fluoxetine and its major active metabolite, changes in dose will not be fully reflected in plasma for several weeks, affecting both strategies for titration to final dose and withdrawal from treatment. This is of potential consequence when drug discontinuation is required or when drugs are prescribed that might interact with fluoxetine and norfluoxetine following the discontinuation of fluoxetine [ see Clinical Pharmacology (12.3) ].

5.25 Discontinuation Adverse Reactions

During marketing of fluoxetine, a component of olanzapine and fluoxetine capsules, SNRIs, and SSRIs, there have been spontaneous reports of adverse reactions occurring upon discontinuation of these drugs, particularly when abrupt, including the following: dysphoric mood, irritability, agitation, dizziness, sensory disturbances (e.g., paresthesias such as electric shock sensations), anxiety, confusion, headache, lethargy, emotional lability, insomnia, and hypomania. While these reactions are generally self-limiting, there have been reports of serious discontinuation symptoms. Patients should be monitored for these symptoms when discontinuing treatment with fluoxetine. A gradual reduction in the dose rather than abrupt cessation is recommended whenever possible. If intolerable symptoms occur following a decrease in the dose or upon discontinuation of treatment, then resuming the previously prescribed dose may be considered. Subsequently, the physician may continue decreasing the dose but at a more gradual rate. Plasma fluoxetine and norfluoxetine concentration decrease gradually at the conclusion of therapy, which may minimize the risk of discontinuation symptoms with this drug [ see Dosage and Administration (2.4) and Patient Counseling Information (17.18)].

5.26 Sexual Dysfunction

Use of SSRIs, including fluoxetine a component of olanzapine and fluoxetine capsules, may cause symptoms of sexual dysfunction [see Adverse Reactions (6.1)]. In male patients, olanzapine and fluoxetine capsules use may result in ejaculatory delay or
failure, decreased libido, and erectile dysfunction. In female patients, olanzapine and fluoxetine capsules use may result in decreased libido and delayed or absent orgasm. It is important for prescribers to inquire about sexual function prior to initiation of
olanzapine and fluoxetine capsules and to inquire specifically about changes in sexual function during treatment, because sexual function may not be spontaneously reported. When evaluating changes in sexual function, obtaining a detailed history (including timing of symptom onset) is important because sexual symptoms may have other causes, including the underlying psychiatric disorder. Discuss potential management strategies to support patients in making informed decisions about treatment.

6 ADVERSE REACTIONS

The following adverse reactions are discussed in more detail in other sections of the labeling:

- Suicidal Thoughts and Behaviors in Children, Adolescents, and Young Adults [see Boxed Warning and Warnings and Precautions (5.1)]
- Increased Mortality in Elderly Patients with Dementia-Related Psychosis [see Warnings and Precautions (5.2)]
- Neuroleptic Malignant syndrome (NMS) [see Warnings and Precautions (5.3)]
- Drug Reaction with Eosinophilia and Systemic Symptoms (DRESS) [see Warnings and Precautions (5.4)]
- Hyperglycemia [see Warnings and Precautions (5.5)]
- Dyslipidemia [see Warnings and Precautions (5.5)]
- Weight Gain [see Warnings and Precautions (5.5)]
- Serotonin Syndrome [see Warnings and Precautions (5.6)]
- Angle-Closure Glaucoma [see Warnings and Precautions (5.7)]
- Allergic Reactions and Rash [see Warnings and Precautions (5.8)]
- Activation of Mania/Hypomania [see Warnings and Precautions (5.9)]
- Tardive Dyskinesia [see Warnings and Precautions (5.10)]
- Orthostatic Hypotension [see Warnings and Precautions (5.11)]
- Falls [see Warnings and Precautions (5.12)]
- Leukopenia, Neutropenia, and Agranulocytosis [see Warnings and Precautions (5.13)]
- Dysphagia [see Warnings and Precautions (5.14)]
- Seizures [see Warnings and Precautions (5.15)]
- Abnormal Bleeding [see Warnings and Precautions (5.16)]
- Hyponatremia [see Warnings and Precautions (5.17)]
- Potential for Cognitive and Motor Impairment [see Warnings and Precautions (5.18)]
- Body Temperature Dysregulation [see Warnings and Precautions (5.19)]
- QT Prolongation [see Warnings and Precautions (5.20)]
- Hyperprolactinemia [see Warnings and Precautions (5.22)]
- Discontinuation Adverse Reactions [see Warnings and Precautions (5.25)]

6.1 Clinical Trials Experience

Because clinical trials are conducted under widely varying conditions, adverse reaction rates observed in the clinical trials of a drug cannot be directly compared to rates in the clinical trials of another drug and may not reflect or predict the rates observed in practice.

The data in the tables represent the proportion of individuals who experienced, at least once, a treatment-emergent adverse reaction of the type listed. A reaction was considered treatment-emergent if it occurred for the first time or worsened while receiving therapy following baseline evaluation.

Adults — The information below is derived from a clinical study database for olanzapine and fluoxetine capsules consisting of 2547 patients with treatment resistant depression, depressive episodes associated with Bipolar I Disorder, Major Depressive Disorder with psychosis, or sexual dysfunction with approximately 1085 patient-years of exposure. The conditions and duration of treatment with olanzapine and fluoxetine capsules varied greatly and included (in overlapping categories) open-label and double-blind phases of studies, inpatients and outpatients, fixed-dose and dose-titration studies, and short-term or long-term exposure.

Adverse Reactions Associated with Discontinuation of Treatment in Short-Term, Controlled Studies Including Depressive Episodes Associated with Bipolar I Disorder and Treatment Resistant Depression — Overall, 11.3% of the 771 patients in the olanzapine and fluoxetine capsule group discontinued due to adverse reactions compared with 4.4% of the 477 patients for placebo. Adverse reactions leading to discontinuation associated with the use of olanzapine and fluoxetine capsules (incidence of at least 1% for olanzapine and fluoxetine capsules and greater than that for placebo) using MedDRA Dictionary coding were weight increased (2%) and sedation (1%) versus placebo patients which had 0% incidence of weight increased and sedation.

Commonly Observed Adverse Reactions in Controlled Studies Including Depressive Episodes Associated with Bipolar I Disorder and Treatment Resistant Depression — In short-term studies, the most commonly observed adverse reactions associated with the use of olanzapine and fluoxetine capsules (incidence ≥5% and at least twice that for placebo in the olanzapine and fluoxetine capsule-controlled database) using MedDRA Dictionary coding were: disturbance in attention, dry mouth, fatigue, hypersomnia, increased appetite, peripheral edema, sedation, somnolence, tremor, vision blurred, and weight increased. Adverse reactions reported in clinical trials of olanzapine and fluoxetine in combination are generally consistent with treatment-emergent adverse reactions during olanzapine or fluoxetine monotherapy.

In a 47 week maintenance study in adults with treatment resistant depression, adverse reactions associated with olanzapine and fluoxetine capsule use were generally similar to those seen in short-term studies. Weight gain, hyperlipidemia, and hyperglycemia were observed in olanzapine and fluoxetine capsule -treated patients throughout the study.

Adverse Reactions Occurring at an Incidence of 2% or More in Short-Term Controlled Studies Including Depressive Episodes Associated with Bipolar I Disorder and Treatment Resistant Depression — Table 16 enumerates the treatment-emergent adverse reactions associated with the use of olanzapine and fluoxetine capsules (incidence of at least 2% for olanzapine and fluoxetine capsules and twice or more than for placebo). The olanzapine and fluoxetine capsule-controlled column includes patients with various diagnoses while the placebo column includes only patients with bipolar depression and major depression with psychotic features.

Table 16: Adverse Reactions: Incidence in the Short-Term Controlled Clinical Studies in Adults
System Organ Class | Adverse Reaction | Percentage of Patients Reporting Event
System Organ Class |  | Olanzapine and Fluoxetine Capsule-Controlled (N=771) | Placebo (N=477)
Eye disorders | Vision blurred | 5 | 2
Gastrointestinal disorders | Dry mouth | 15 | 6
Gastrointestinal disorders | Flatulence | 3 | 1
Gastrointestinal disorders | Abdominal distension | 2 | 0
General disorders and administration site conditions | Fatigue | 12 | 2
General disorders and administration site conditions | Edemaa | 15 | 2
General disorders and administration site conditions | Asthenia | 3 | 1
General disorders and administration site conditions | Pain | 2 | 1
General disorders and administration site conditions | Pyrexia | 2 | 1
Infections and infestations | Sinusitis | 2 | 1
Investigations | Weight increased | 25 | 3
Metabolism and nutrition disorders | Increased appetite | 20 | 4
Musculoskeletal and connective tissue disorders | Arthralgia | 4 | 1
Musculoskeletal and connective tissue disorders | Pain in extremity | 3 | 1
Musculoskeletal and connective tissue disorders | Musculoskeletal stiffness | 2 | 1
Nervous system disorders | Somnolenceb | 27 | 11
Nervous system disorders | Tremor | 9 | 3
Nervous system disorders | Disturbance in attention | 5 | 1
Psychiatric disorders | Restlessness | 4 | 1
Psychiatric disorders | Thinking abnormal | 2 | 1
Psychiatric disorders | Nervousness | 2 | 1
Reproductive system and breast disorders | Erectile dysfunction | 2 | 1

a Includes edema, edema peripheral, pitting edema, generalized edema, eyelid edema, face edema, gravitational edema,
localized edema, periorbital edema, swelling, joint swelling, swelling face, and eye swelling.

b Includes somnolence, sedation, hypersomnia, and lethargy.

Extrapyramidal Symptoms

Dystonia, Class Effect for Antipsychotics — Symptoms of dystonia, prolonged abnormal contractions of muscle groups, may occur in susceptible individuals during the first few days of treatment. Dystonic symptoms include: spasm of the neck muscles, sometimes progressing to tightness of the throat, swallowing difficulty, difficulty breathing, and/or protrusion of the tongue. While these symptoms can occur at low doses, the frequency and severity are greater with high potency and at higher doses of first generation antipsychotic drugs. In general, an elevated risk of acute dystonia may be observed in males and younger age groups receiving antipsychotics; however, events of dystonia have been reported infrequently (<1%) with the olanzapine and fluoxetine combination.

Additional Findings Observed in Clinical Studies

Sexual Dysfunction — In the pool of controlled olanzapine and fluoxetine capsule studies in patients with bipolar depression, there were higher rates of the treatment-emergent adverse reactions decreased libido, anorgasmia, erectile dysfunction and abnormal ejaculation in the olanzapine and fluoxetine capsule group than in the placebo group. One case of decreased libido led to discontinuation in the olanzapine and fluoxetine capsule group. In the controlled studies that contained a fluoxetine arm, the rates of decreased libido and abnormal ejaculation in the olanzapine and fluoxetine capsule group were less than the rates in the fluoxetine group. None of the differences were statistically significant.

Sexual dysfunction, including priapism, has been reported with all SSRIs. While it is difficult to know the precise risk of sexual dysfunction associated with the use of SSRIs, physicians should routinely inquire about such possible side effects.

There are no adequate and well-controlled studies examining sexual dysfunction with olanzapine and fluoxetine capsule or fluoxetine treatment. Symptoms of sexual dysfunction occasionally persist after discontinuation of fluoxetine treatment.

Difference Among Dose Levels Observed in Other Olanzapine Clinical Trials

In a single 8 week randomized, double-blind, fixed-dose study comparing 10 (N=199), 20 (N=200), and 40 (N=200) mg/day of olanzapine in patients with Schizophrenia or Schizoaffective Disorder, statistically significant differences among 3 dose groups were observed for the following safety outcomes: weight gain, prolactin elevation, fatigue, and dizziness. Mean baseline to endpoint increase in weight (10 mg/day: 1.9 kg; 20 mg/day: 2.3 kg; 40 mg/day: 3 kg) was observed with significant differences between 10 vs 40 mg/day. Incidence of treatment-emergent prolactin elevation >24.2 ng/mL (female) or >18.77 ng/mL (male) at any time during the trial (10 mg/day: 31.2%; 20 mg/day: 42.7%; 40 mg/day: 61.1%) with significant differences between 10 vs 40 mg/day and 20 vs 40 mg/day; fatigue (10 mg/day: 1.5%; 20 mg/day: 2.1%; 40 mg/day: 6.6%) with significant differences between 10 vs 40 and 20 vs 40 mg/day; and dizziness (10 mg/day: 2.6%; 20 mg/day: 1.6%; 40 mg/day: 6.6%) with significant differences between 20 vs 40 mg, was observed.

Other Adverse Reactions Observed in Clinical Studies

Following is a list of treatment-emergent adverse reactions reported by patients treated with olanzapine and fluoxetine capsules in clinical trials. This listing is not intended to include reactions (1) already listed in previous tables or elsewhere in labeling, (2) for which a drug cause was remote, (3) which were so general as to be uninformative, (4) which were not considered to have significant clinical implications, or (5) which occurred at a rate equal to or less than placebo.

Reactions are classified by body system using the following definitions: frequent adverse reactions are those occurring in at least 1/100 patients; infrequent adverse reactions are those occurring in 1/100 to 1/1000 patients; and rare reactions are those occurring in fewer than 1/1000 patients.

Body as a Whole — Frequent: chills, neck rigidity, photosensitivity reaction; Rare: death^1.

Cardiovascular System — Frequent: vasodilatation.

Digestive System — Frequent: diarrhea; Infrequent: gastritis, gastroenteritis, nausea and vomiting, peptic ulcer; Rare: gastrointestinal hemorrhage, intestinal obstruction, liver fatty deposit, pancreatitis.

Hemic and Lymphatic System — Frequent: ecchymosis; Infrequent: anemia, thrombocytopenia; Rare: leukopenia, purpura.

Metabolic and Nutritional — Frequent: generalized edema, weight loss; Rare: bilirubinemia, creatinine increased, gout.

Musculoskeletal System — Rare: osteoporosis.

Nervous System — Frequent: amnesia; Infrequent: ataxia, buccoglossal syndrome, coma, depersonalization, dysarthria, emotional lability, euphoria, hypokinesia, movement disorder, myoclonus; Rare: hyperkinesia, libido increased, withdrawal syndrome.

Respiratory System — Infrequent: epistaxis, yawn; Rare: laryngismus.

Skin and Appendages — Infrequent: alopecia, dry skin, pruritus; Rare: exfoliative dermatitis.

Special Senses — Frequent: taste perversion; Infrequent: abnormality of accommodation, dry eyes.

Urogenital System — Frequent: breast pain, menorrhagia^2, urinary frequency, urinary incontinence; Infrequent: amenorrhea^2, female lactation^2, hypomenorrhea^2, metrorrhagia^2, urinary retention, urinary urgency, urination impaired; Rare: breast engorgement^2.

^1 This term represents a serious adverse event but does not meet the definition for adverse drug reactions. It is included here because of its seriousness.

^2 Adjusted for gender.

Other Adverse Reactions Observed with Olanzapine or Fluoxetine Monotherapy

The following adverse reactions were not observed in olanzapine and fluoxetine capsule-treated patients during premarketing clinical studies but have been reported with olanzapine or fluoxetine monotherapy: aplastic anemia, bruxism, cholestatic jaundice, diabetic coma, dysuria, eosinophilic pneumonia^3, erythema multiforme, esophageal ulcer, gynecological bleeding, headache, hypotension, jaundice, neutropenia, restless legs syndrome, stuttering^3, sudden unexpected death^4, sweating, and violent behaviors^3. Random triglyceride levels of ≥1000 mg/dL have been reported.

^3 Stuttering was only studied in oral and long acting injection (LAI) olanzapine formulations

^4 These terms represent serious adverse events but do not meet the definition for adverse drug reactions. They are included here because of their seriousness.

Children and Adolescent Patients (aged 10 to 17 years) with a Diagnosis of Bipolar Depression

The information below is derived from a single, 8 week, randomized, placebo-controlled clinical trial investigating olanzapine and fluoxetine capsules for the treatment of bipolar I depression in patients 10 to 17 years of age.

Adverse Reactions Associated with Discontinuation of Treatment in the single pediatric study — Overall, 14.1% of the 170 patients in the olanzapine and fluoxetine capsule group discontinued due to adverse reactions compared with 5.9% of the 85 patients for placebo. Adverse reactions leading to discontinuation associated with the use of olanzapine and fluoxetine capsules (incidence of at least 1% for olanzapine and fluoxetine capsules and greater than that for placebo) using MedDRA Dictionary coding were weight increased (2.9%), suicidal ideation (1.8%), bipolar disorder (1.2%), and somnolence (1.2%) versus placebo patients which had 0% incidence of weight increased, bipolar disorder, and somnolence, and a 1.2% incidence of suicidal ideation.

Adverse Reactions Occurring at an Incidence of 2% or more and greater than placebo — Table 17 enumerates the treatment-emergent adverse reactions associated with the use of olanzapine and fluoxetine capsules (incidence of at least 2% for olanzapine and fluoxetine capsules and twice or more than for placebo).

Table 17: Treatment-Emergent Adverse Reactions: Incidence in a 8-week randomized, double-blind, placebo-controlled clinical trial in pediatric bipolar I depression.
System Organ Class | Adverse Reaction | Percentage of Patients Reporting Event
System Organ Class | Adverse Reaction | Olanzapine and Fluoxetine Capsules; (N=170) | Placebo; (N=85)
Nervous system disorders | Somnolencea | 24 | 2
 | Tremor | 9 | 1
Investigations | Weight increased | 20 | 1
 | Blood triglycerides increased | 7 | 2
 | Blood cholesterol increased | 4 | 0
 | Hepatic enzyme increasedb | 9 | 1
Gastrointestinal disorders | Dyspepsia | 3 | 1
Metabolism and nutrition disorders | Increased appetite | 17 | 1
Psychiatric disorders | Anxiety | 3 | 1
 | Restlessness | 3 | 1
 | Suicidal ideation | 2 | 1
Musculoskeletal and connective tissue disorders | Back pain | 2 | 1
Injury, poisoning and procedural complications | Accidental overdose | 3 | 1
Reproductive system and breast disorders | Dysmenorrhea | 2 | 0

a Includes somnolence, sedation, and hypersomnia. No lethargy was reported.

b Includes alanine aminotransferase increased, aspartate aminotransferase increased, hepatic enzyme increased, liver function test
abnormal, gamma-glutamyltransferase increased, and transaminases increased.

6.2 Vital Signs and Laboratory Studies

Adults:

Vital Signs — Tachycardia, bradycardia, and orthostatic hypotension have occurred in olanzapine and fluoxetine capsule-treated patients [ see Warnings and Precautions (5.11)]. The mean standing pulse rate of olanzapine and fluoxetine capsule-treated patients was reduced by 0.7 beats/min.

Laboratory Changes — In olanzapine and fluoxetine capsule clinical studies (including treatment resistant depression, depressive episodes associated with Bipolar I Disorder, Major Depressive Disorder with psychosis, or sexual dysfunction), olanzapine and fluoxetine capsules were associated with statistically significantly greater frequencies for the following treatment-emergent findings in laboratory analytes (normal at baseline to abnormal at any time during the trial) compared to placebo: elevated prolactin (28% vs 5%); elevated urea nitrogen (3% vs 0.8%); elevated uric acid (3% vs 0.5%); low albumin (3% vs 0.3%); low bicarbonate (14% vs 9%); low hemoglobin (3% vs 0%); low inorganic phosphorus (2% vs 0.3%); low lymphocytes (2% vs 0%); and low total bilirubin (15% vs 4%).

As with olanzapine, asymptomatic elevations of hepatic aminotransferases [ALT, AST, and GGT] and alkaline phosphatase have been observed with olanzapine and fluoxetine capsules. In the olanzapine and fluoxetine capsule-controlled database, clinically significant ALT elevations (change from <3 times the upper limit of normal [ULN] at baseline to ≥3 times ULN) were observed in 5% (38/698) of patients exposed to olanzapine and fluoxetine capsules compared with 0.5% (2/378) of placebo-treated patients and 4% (33/751) of olanzapine-treated patients. ALT elevations ≥5 times ULN were observed in 2% (11/701) of olanzapine and fluoxetine capsule-treated patients, compared to 0.3% (1/379) of placebo-treated patients and 1% (11/760) of olanzapine-treated patients. No patient with elevated ALT values experienced jaundice or liver failure, or met the criteria for Hy's Rule. ALT values returned to normal, or were decreasing, at last follow-up in the majority of patients who either continued treatment with olanzapine and fluoxetine capsules or discontinued olanzapine and fluoxetine capsules.

Rare postmarketing reports of hepatitis have been received in patients treated with olanzapine. Very rare cases of cholestatic or mixed liver injury have also been reported in the postmarketing period in patients treated with olanzapine.

Caution should be exercised in patients with signs and symptoms of hepatic impairment, in patients with pre-existing conditions associated with limited hepatic functional reserve, and in patients who are being treated with potentially hepatotoxic drugs.

An increase in creatine phosphokinase has been reported very rarely in olanzapine and fluoxetine capsule-treated patients and infrequently in clinical trials of olanzapine-treated patients.

QT Interval Prolongation — In patients treated with olanzapine and fluoxetine capsules QTcF≥450 msec for males and QTcF≥470 msec for females has been reported frequently (≥1%). The incidence of QTcF>500 msec associated with olanzapine and fluoxetine capsule treatment in clinical trials has been rare and was not significantly different from the incidence associated with placebo. The mean increase in QTc interval for olanzapine and fluoxetine capsule-treated patients (5.17 msec) in the one clinical study directly comparing olanzapine and fluoxetine capsules to placebo in adult patients was significantly greater than that for placebo-treated patients (-1.66 msec).

Children and Adolescents (aged 10 to 17 years):

In a single 8 week randomized, placebo-controlled clinical trial investigating olanzapine and fluoxetine capsules for treatment of bipolar I depression in patients 10 to 17 years of age, the following was observed:

Vital Signs — In the olanzapine and fluoxetine capsule-treated patients compared with placebo-treated patients, the mean orthostatic blood pressure and standing pulse rate were not significantly different between treatment groups.

Body Weight: An increase in weight greater than or equal to 7% occurred in 52.4% of the olanzapine and fluoxetine capsule group and 3.6% of the placebo group. Weight gain greater than or equal to 15% occurred in 14.1% of the olanzapine and fluoxetine capsule group and none of the placebo group.

Laboratory Changes — Olanzapine and fluoxetine capsules were associated with statistically significantly greater frequencies for the following treatment-emergent findings in laboratory analytes (normal or low at baseline to abnormal at any time during the trial) compared to placebo: elevated ALT (45.9% vs 2.5%); elevated AST (33.7% vs 7.6%); high fasting total cholesterol (28.9% vs 8.2%); high fasting LDL cholesterol (19.7% vs 6.5%); high fasting triglycerides (52.3% vs 27.3%), and elevated prolactin (85% vs 36%). No patient with elevated hepatic enzyme values experienced jaundice or liver failure, or met the criteria for Hy’s Rule. Five patients experienced an adverse event potentially associated with elevated prolactin; these events included dysmenorrhoea, galactorrhoea, and ovulation disorder.

QT Interval Prolongation — Olanzapine and fluoxetine capsules were associated with a statistically significantly greater mean increase in QTcF interval (8.2 msec [95% CI 6.2, 10.2]) compared with placebo. No patients developed QTc increases ≥60 msec or QTc ≥480 msec [ see Warnings and Precautions (5.20)].

6.3 Postmarketing Experience

The following adverse reactions have been identified during post-approval use of olanzapine and fluoxetine capsules. Because these reactions are reported voluntarily from a population of uncertain size, it is difficult to reliably estimate their frequency or evaluate a causal relationship to drug exposure.

Adverse reactions reported since market introduction that were temporally (but not necessarily causally) related to olanzapine and fluoxetine capsule therapy include the following: rhabdomyolysis and venous thromboembolic events (including pulmonary embolism and deep venous thrombosis).

To report SUSPECTED ADVERSE REACTIONS, contact AvKARE at 1-855-361-3993; email drugsafety@avkare.com; or FDA at 1-800-FDA-1088 or www.fda.gov/medwatch.

7 DRUG INTERACTIONS

The risks of using olanzapine and fluoxetine capsules in combination with other drugs have not been extensively evaluated in systematic studies. The drug-drug interactions sections of fluoxetine and olanzapine are applicable to olanzapine and fluoxetine capsules. As with all drugs, the potential for interaction by a variety of mechanisms (e.g., pharmacodynamic, pharmacokinetic drug inhibition or enhancement, etc.) is a possibility. In evaluating individual cases, consideration should be given to using lower initial doses of the concomitantly administered drugs, using conservative titration schedules, and monitoring of clinical status [see Clinical Pharmacology (12.3)].

7.1 Monoamine Oxidase Inhibitors (MAOIs)

[ See Dosage and Administration (2.4, 2.5), Contraindications (4.1), and Warnings and Precautions (5.6) ].

7.2 CNS Acting Drugs

Caution is advised if the concomitant administration of olanzapine and fluoxetine capsules and other CNS-active drugs is required. In evaluating individual cases, consideration should be given to using lower initial doses of the concomitantly administered drugs, using conservative titration schedules, and monitoring of clinical status [ see Clinical Pharmacology (12.3) ].

7.3 Serotonergic Drugs

[ See Dosage and Administration (2.4, 2.5), Contraindications (4.1), and Warnings and Precautions (5.6) ].

7.4 Drugs that Interfere with Hemostasis (e.g., NSAIDs, Aspirin, Warfarin)

Serotonin release by platelets plays an important role in hemostasis. Epidemiological studies of the case-control and cohort design that have demonstrated an association between use of psychotropic drugs that interfere with serotonin reuptake and the occurrence of upper gastrointestinal bleeding have also shown that concurrent use of an NSAID or aspirin may potentiate this risk of bleeding. Altered anticoagulant effects, including increased bleeding, have been reported when SNRIs or SSRIs are coadministered with warfarin [ see Warnings and Precautions (5.16)]. Warfarin (20 mg single dose) did not affect olanzapine pharmacokinetics. Single doses of olanzapine did not affect the pharmacokinetics of warfarin. Patients receiving warfarin therapy should be carefully monitored when olanzapine and fluoxetine capsules are initiated or discontinued.

7.5 Electroconvulsive Therapy (ECT)

There are no clinical studies establishing the benefit of the combined use of ECT and fluoxetine. There have been rare reports of prolonged seizures in patients on fluoxetine receiving ECT treatment [ see Warnings and Precautions (5.15)].

7.6 Potential for Other Drugs to Affect Olanzapine and Fluoxetine Capsules

Benzodiazepines — Coadministration of diazepam with olanzapine potentiated the orthostatic hypotension observed with olanzapine [ see Drug Interactions (7.7) ].

Inducers of 1A2 — Carbamazepine therapy (200 mg BID) causes an approximate 50% increase in the clearance of olanzapine. This increase is likely due to the fact that carbamazepine is a potent inducer of CYP1A2 activity. Higher daily doses of carbamazepine may cause an even greater increase in olanzapine clearance [ see Drug Interactions (7.7) ].

Alcohol — Ethanol (45 mg/70 kg single dose) did not have an effect on olanzapine pharmacokinetics [ see Drug Interactions (7.7) ].

Inhibitors of CYP1A2 — Fluvoxamine decreases the clearance of olanzapine. This results in a mean increase in olanzapine Cmax following fluvoxamine administration of 54% in female nonsmokers and 77% in male smokers. The mean increase in olanzapine AUC is 52% and 108%, respectively. Lower doses of the olanzapine component of olanzapine and fluoxetine capsules should be considered in patients receiving concomitant treatment with fluvoxamine.

The Effect of Other Drugs on Olanzapine — Fluoxetine, an inhibitor of CYP2D6, decreases olanzapine clearance a small amount [ see Clinical Pharmacology (12.3) ]. Agents that induce CYP1A2 or glucuronyl transferase enzymes, such as omeprazole and rifampin, may cause an increase in olanzapine clearance. The effect of CYP1A2 inhibitors, such as fluvoxamine and some fluoroquinolone antibiotics, on olanzapine and fluoxetine capsules has not been evaluated. Although olanzapine is metabolized by multiple enzyme systems, induction or inhibition of a single enzyme may appreciably alter olanzapine clearance. Therefore, a dosage increase (for induction) or a dosage decrease (for inhibition) may need to be considered with specific drugs.

7.7 Potential for Olanzapine and Fluoxetine Capsules to Affect Other Drugs

Pimozide — Concomitant use of olanzapine and fluoxetine capsules and pimozide is contraindicated. Pimozide can prolong the QT interval. Olanzapine and fluoxetine capsules can increase the level of pimozide through inhibition of CYP2D6. Olanzapine and fluoxetine capsules can also prolong the QT interval. Clinical studies of pimozide with other antidepressants demonstrate an increase in drug interaction or QTc prolongation. While a specific study with pimozide and olanzapine and fluoxetine capsules has not been conducted, the potential for drug interactions or QTc prolongation warrants restricting the concurrent use of pimozide and olanzapine and fluoxetine capsules [ see Contraindications (4.2), Warnings and Precautions (5.20), and Drug Interactions (7.8) ].

Carbamazepine — Patients on stable doses of carbamazepine have developed elevated plasma anticonvulsant concentrations and clinical anticonvulsant toxicity following initiation of concomitant fluoxetine treatment.

Alcohol — The coadministration of ethanol with olanzapine and fluoxetine capsules may potentiate sedation and orthostatic hypotension [ see Drug Interactions (7.6) ].

Thioridazine — Thioridazine should not be administered with olanzapine and fluoxetine capsules or administered within a minimum of 5 weeks after discontinuation of olanzapine and fluoxetine capsules because of the risk of QT prolongation [ see Contraindications (4.2), Warnings and Precautions (5.20), and Drug Interactions (7.8) ].

In a study of 19 healthy male subjects, which included 6 slow and 13 rapid hydroxylators of debrisoquin, a single 25 mg oral dose of thioridazine produced a 2.4-fold higher Cmax and a 4.5-fold higher AUC for thioridazine in the slow hydroxylators compared with the rapid hydroxylators. The rate of debrisoquin hydroxylation is felt to depend on the level of CYP2D6 isozyme activity. Thus, this study suggests that drugs that inhibit CYP2D6, such as certain SSRIs, including fluoxetine, will produce elevated plasma levels of thioridazine [ see Contraindications (4.2) ].

Thioridazine administration produces a dose-related prolongation of the QTc interval, which is associated with serious ventricular arrhythmias, such as torsade de pointes-type arrhythmias and sudden death. This risk is expected to increase with fluoxetine-induced inhibition of thioridazine metabolism [ see Contraindications (4.2) ].

Due to the risk of serious ventricular arrhythmias and sudden death potentially associated with elevated thioridazine plasma levels, thioridazine should not be administered with fluoxetine or within a minimum of 5 weeks after fluoxetine has been discontinued [ see Contraindications (4.2) ].

Tricyclic Antidepressants (TCAs) — Single doses of olanzapine did not affect the pharmacokinetics of imipramine or its active metabolite desipramine.

In 2 fluoxetine studies, previously stable plasma levels of imipramine and desipramine have increased >2- to 10-fold when fluoxetine has been administered in combination. This influence may persist for 3 weeks or longer after fluoxetine is discontinued. Thus, the dose of TCA may need to be reduced and plasma TCA concentrations may need to be monitored temporarily when olanzapine and fluoxetine capsules are coadministered or has been recently discontinued [ see Warnings and Precautions (5.6) and Clinical Pharmacology (12.3) ].

Antihypertensive Agents — Because of the potential for olanzapine to induce hypotension, olanzapine and fluoxetine capsules may enhance the effects of certain antihypertensive agents [ see Warnings and Precautions (5.11)].

Levodopa and Dopamine Agonists — The olanzapine component of olanzapine and fluoxetine capsules may antagonize the effects of levodopa and dopamine agonists.

Benzodiazepines — Multiple doses of olanzapine did not influence the pharmacokinetics of diazepam and its active metabolite N-desmethyldiazepam.

When concurrently administered with fluoxetine, the half-life of diazepam may be prolonged in some patients [ see Clinical Pharmacology (12.3) ]. Coadministration of alprazolam and fluoxetine has resulted in increased alprazolam plasma concentrations and in further psychomotor performance decrement due to increased alprazolam levels.

Clozapine — Elevation of blood levels of clozapine has been observed in patients receiving concomitant fluoxetine.

Haloperidol — Elevation of blood levels of haloperidol has been observed in patients receiving concomitant fluoxetine.

Phenytoin — Patients on stable doses of phenytoin have developed elevated plasma levels of phenytoin with clinical phenytoin toxicity following initiation of concomitant fluoxetine.

Drugs Metabolized by CYP2D6 — In vitro studies utilizing human liver microsomes suggest that olanzapine has little potential to inhibit CYP2D6. Thus, olanzapine is unlikely to cause clinically important drug interactions mediated by this enzyme.

Fluoxetine inhibits the activity of CYP2D6 and may make individuals with normal CYP2D6 metabolic activity resemble a poor metabolizer. Coadministration of fluoxetine with other drugs that are metabolized by CYP2D6, including certain antidepressants (e.g., TCAs), antipsychotics (e.g., phenothiazines and most atypicals), and antiarrhythmics (e.g., propafenone, flecainide, and others) should be approached with caution. Therapy with medications that are predominantly metabolized by the CYP2D6 system and that have a relatively narrow therapeutic index should be initiated at the low end of the dose range if a patient is receiving fluoxetine concurrently or has taken it in the previous 5 weeks. If fluoxetine is added to the treatment regimen of a patient already receiving a drug metabolized by CYP2D6, the need for a decreased dose of the original medication should be considered. Drugs with a narrow therapeutic index represent the greatest concern (including but not limited to, flecainide, propafenone, vinblastine, and TCAs).

Drugs Metabolized by CYP3A — In vitro studies utilizing human liver microsomes suggest that olanzapine has little potential to inhibit CYP3A. Thus, olanzapine is unlikely to cause clinically important drug interactions mediated by these enzymes.

In an in vivo interaction study involving the coadministration of fluoxetine with single doses of terfenadine (a CYP3A substrate), no increase in plasma terfenadine concentrations occurred with concomitant fluoxetine. In addition, in vitro studies have shown ketoconazole, a potent inhibitor of CYP3A activity, to be at least 100 times more potent than fluoxetine or norfluoxetine as an inhibitor of the metabolism of several substrates for this enzyme, including astemizole, cisapride, and midazolam. These data indicate that fluoxetine’s extent of inhibition of CYP3A activity is not likely to be of clinical significance.

Effect of Olanzapine on Drugs Metabolized by Other CYP Enzymes — In vitro studies utilizing human liver microsomes suggest that olanzapine has little potential to inhibit CYP1A2, CYP2C9, and CYP2C19. Thus, olanzapine is unlikely to cause clinically important drug interactions mediated by these enzymes.

Lithium — Multiple doses of olanzapine did not influence the pharmacokinetics of lithium.

There have been reports of both increased and decreased lithium levels when lithium was used concomitantly with fluoxetine. Cases of lithium toxicity and increased serotonergic effects have been reported. Lithium levels should be monitored in patients taking olanzapine and fluoxetine capsules concomitantly with lithium [ see Warnings and Precautions (5.5) ].

Drugs Tightly Bound to Plasma Proteins — The in vitro binding of olanzapine and fluoxetine capsules to human plasma proteins is similar to the individual components. The interaction between olanzapine and fluoxetine capsules and other highly protein-bound drugs has not been fully evaluated. Because fluoxetine is tightly bound to plasma protein, the administration of fluoxetine to a patient taking another drug that is tightly bound to protein (e.g., warfarin, digitoxin) may cause a shift in plasma concentrations potentially resulting in an adverse effect. Conversely, adverse effects may result from displacement of protein-bound fluoxetine by other tightly bound drugs [ see Clinical Pharmacology (12.3) ].

Valproate — In vitro studies using human liver microsomes determined that olanzapine has little potential to inhibit the major metabolic pathway, glucuronidation, of valproate. Further, valproate has little effect on the metabolism of olanzapine in vitro. Thus, a clinically significant pharmacokinetic interaction between olanzapine and valproate is unlikely.

Biperiden — Multiple doses of olanzapine did not influence the pharmacokinetics of biperiden.

Theophylline — Multiple doses of olanzapine did not affect the pharmacokinetics of theophylline or its metabolites.

7.8 Drugs that Prolong the QT Interval

Do not use olanzapine and fluoxetine capsules in combination with thioridazine or pimozide. Use olanzapine and fluoxetine capsules with caution in combination with other drugs that cause QT prolongation. These include: specific antipsychotics (e.g., ziprasidone, iloperidone, chlorpromazine, mesoridazine, droperidol); specific antibiotics (e.g., erythromycin, gatifloxacin, moxifloxacin, sparfloxacin); Class 1A antiarrhythmic medications (e.g., quinidine, procainamide); Class III antiarrhythmics (e.g., amiodarone, sotalol); and others (e.g., pentamidine, levomethadyl acetate, methadone, halofantrine, mefloquine, dolasetron mesylate, probucol or tacrolimus). Fluoxetine is primarily metabolized by CYP2D6. Concomitant treatment with CYP2D6 inhibitors can increase the concentration of fluoxetine. Concomitant use of other highly protein-bound drugs can increase the concentration of fluoxetine [ see Contraindications (4.2), Warnings and Precautions (5.20), Drug Interactions (7.7), and Clinical Pharmacology (12.3) ].

8 USE IN SPECIFIC POPULATIONS

8.1 Pregnancy

Risk Summary

There are no adequate and well-controlled clinical studies with olanzapine and fluoxetine capsules or their components (olanzapine and fluoxetine) in pregnant women.

A number of published epidemiological studies assessing the risk of fluoxetine exposure during the first trimester of pregnancy have demonstrated inconsistent results.

Neonates exposed to fluoxetine, a component of olanzapine and fluoxetine capsules, and other SSRIs and SNRIs late in the third trimester have developed complications arising immediately upon delivery (respiratory distress, cyanosis, apnea, seizures, temperature instability, feeding difficulty, vomiting, hypoglycemia, hypotonia, hypertonia, hyperreflexia, tremor, jitteriness, irritability, and constant crying) requiring prolonged hospitalization, respiratory support, and tube feeding. These features are consistent with either a direct toxic effect of SSRIs and SNRIs or, possibly, a drug discontinuation syndrome. In some cases, the clinical picture is consistent with serotonin syndrome. Neonates exposed to olanzapine, a component of olanzapine and fluoxetine capsules, during the third trimester of pregnancy are at risk for extrapyramidal and/or withdrawal symptoms following delivery including agitation, hypertonia, hypotonia, tremor, somnolence, respiratory distress and feeding disorder. These complications have varied in severity; while in some cases symptoms have been self-limited, in other cases neonates have required intensive care unit support and prolonged hospitalization.

Infants exposed to SSRIs in pregnancy may have an increased risk for persistent pulmonary hypertension of the newborn (PPHN).

Olanzapine and fluoxetine capsules should be used during pregnancy only if the potential benefit justifies the potential risk to the fetus, taking into account the risk of untreated Bipolar I Depression or Treatment Resistant Depression.

Human Data

There are no adequate and well-controlled clinical studies with olanzapine and fluoxetine capsules, olanzapine or fluoxetine in pregnant women. Seven pregnancies were observed during premarketing clinical studies with olanzapine, including 2 resulting in normal births, 1 resulting in neonatal death due to a cardiovascular defect, 3 therapeutic abortions, and 1 spontaneous abortion. Results of a number of published epidemiological studies assessing the risk of fluoxetine exposure during the first trimester of pregnancy have demonstrated inconsistent results. More than 10 cohort studies and case-control studies failed to demonstrate an increased risk for congenital malformations overall. However, one prospective cohort study conducted by the European Network of Teratology Information Services reported an increased risk of cardiovascular malformations in infants born to women (N = 253) exposed to fluoxetine during the first trimester of pregnancy compared to infants of women (N = 1359) who were not exposed to fluoxetine. There was no specific pattern of cardiovascular malformations. Overall, however, a causal relationship has not been established.

Neonates exposed to fluoxetine, a component of olanzapine and fluoxetine capsules, and other SSRIs or serotonin and norepinephrine reuptake inhibitors (SNRIs), late in the third trimester have developed complications requiring prolonged hospitalization, respiratory support, and tube feeding. Such complications can arise immediately upon delivery. Reported clinical findings have included respiratory distress, cyanosis, apnea, seizures, temperature instability, feeding difficulty, vomiting, hypoglycemia, hypotonia, hypertonia, hyperreflexia, tremor, jitteriness, irritability, and constant crying. These features are consistent with either a direct toxic effect of SSRIs and SNRIs or, possibly, a drug discontinuation syndrome. It should be noted that, in some cases, the clinical picture is consistent with serotonin syndrome [ see Dosage and Administration (2.3) and Warnings and Precautions (5.6) ].

Infants exposed to SSRIs in pregnancy may have an increased risk for persistent pulmonary hypertension of the newborn (PPHN). PPHN occurs in 1 to 2 per 1,000 live births in the general population and is associated with substantial neonatal morbidity and mortality. Several recent epidemiologic studies suggest a positive statistical association between SSRI (including fluoxetine) use in pregnancy and PPHN. Other studies do not show a significant statistical association.

Neonates exposed to antipsychotic drugs (including olanzapine, a component of olanzapine and fluoxetine capsules), during the third trimester of pregnancy are at risk for extrapyramidal and/or withdrawal symptoms following delivery. There have been reports of agitation, hypertonia, hypotonia, tremor, somnolence, respiratory distress and feeding disorder in these neonates. These complications have varied in severity; while in some cases symptoms have been self-limited, in other cases neonates have required intensive care unit support and prolonged hospitalization.

Physicians should also note the results of a prospective longitudinal study of 201 pregnant women with a history of major depression, who were either on antidepressants or had received antidepressants less than 12 weeks prior to their last menstrual period, and were in remission. Women who discontinued antidepressant medication during pregnancy showed a significant increase in relapse of their major depression compared to those women who remained on antidepressant medication throughout pregnancy.

When treating a pregnant woman with olanzapine and fluoxetine capsules, the physician should carefully consider both the potential risks of taking an SSRI, along with the established benefits of treating depression with an antidepressant. This decision can only be made on a case by case basis [ see Dosage and Administration (2.3) ].

Olanzapine and fluoxetine capsules should be used during pregnancy only if the potential benefit justifies the potential risk to the fetus.

Animal Data

Olanzapine and fluoxetine capsules — Embryo fetal development studies were conducted in rats and rabbits with olanzapine and fluoxetine in low-dose and high-dose combinations. In rats, the doses were: 2 and 4 mg/kg/day (low-dose) [1 and 0.5 times the maximum recommended human dose (MRHD) for olanzapine (20 mg) and fluoxetine (80 mg), respectively on a mg/m^2 body surface area], and 4 and 8 mg/kg/day (high-dose) [2 and 1 times the MRHD on a mg/m^2 body surface area, respectively]. In rabbits, the doses were 4 and 4 mg/kg/day (low-dose) [4 and 1 times the MRHD on a mg/m^2 basis, respectively], and 8 and 8 mg/kg/day (high-dose) [9 and 2 times the MRHD on a mg/m^2 basis, respectively]. In these studies, olanzapine and fluoxetine were also administered alone at the high-doses (4 and 8 mg/kg/day, respectively, in the rat; 8 and 8 mg/kg/day, respectively, in the rabbit). In the rabbit, there was no evidence of teratogenicity; however, the high-dose combination produced decreases in fetal weight and retarded skeletal ossification in conjunction with maternal toxicity. Similarly, in the rat there was no evidence of teratogenicity; however, a decrease in fetal weight was observed with the high-dose combination.

In a pre- and postnatal study conducted in rats, olanzapine and fluoxetine were orally administered during pregnancy and throughout lactation in combination at dose levels up to 2 (olanzapine) plus 4 (fluoxetine) mg/kg/day (1 and 0.5 times the MRHD on a mg/m^2 body surface area. An elevation of early postnatal mortality (survival through postnatal day 4 was 69% per litter) and reduced bodyweight (approximately 8% in female) occurred among offspring at the highest dose: the no-effect dose was 0.5 (olanzapine) plus 1 (fluoxetine) mg/kg/day (0.25 and 0.13 times the MRHD on a mg/m^2 body surface area). Among the surviving progeny, there were no adverse effects on physical or neurobehavioral development and reproductive performance at any dose.

Olanzapine — In oral embryo-fetal studies in rats and rabbits, there was no evidence of teratogenicity following administration of olanzapine at doses up to 18 and 30 mg/kg/day, respectively (9 and 30 times the MRHD on a mg/m^2 basis, respectively). In a rat teratology study, early resorptions and increased numbers of dead fetuses were observed at a dose of 18 mg/kg/day (9 times the MRHD on a mg/m^2 basis). Gestation was prolonged at 10 mg/kg/day (5 times the MRHD on a mg/m^2 basis). In a rabbit teratology study, fetal toxicity (manifested as increased resorptions and decreased fetal weight) occurred at a maternally toxic dose of 30 mg/kg/day (30 times the MRHD on a mg/m^2 basis). Because animal reproduction studies are not always predictive of human response, this drug should be used during pregnancy only if the potential benefit justifies the potential risk to the fetus.

Placental transfer of olanzapine occurs in rat pups.

Fluoxetine — In oral embryo-fetal development studies in rats and rabbits, there was no evidence of teratogenicity following administration of fluoxetine at doses up to 12.5 and 15 mg/kg/day, respectively (1.5 and 3.6 times, respectively, the MRHD of 80 mg/day on a mg/m^2 basis) throughout organogenesis. However, in rat reproduction studies, an increase in stillborn pups, a decrease in pup weight, and an increase in pup deaths during the first 7 days postpartum occurred following maternal exposure to 12 mg/kg/day (1.5 times the MRHD on a mg/m^2 basis) during gestation or 7.5 mg/kg/day (0.9 times the MRHD on a mg/m^2 basis) during gestation and lactation. There was no evidence of developmental neurotoxicity in the surviving offspring of rats treated with 12 mg/kg/day during gestation. The no-effect dose for rat pup mortality was 5 mg/kg/day (0.6 times the MRHD on a mg/m^2 basis).

8.2 Labor and Delivery

Olanzapine and fluoxetine capsules — The effect of olanzapine and fluoxetine capsules on labor and delivery in humans is unknown. Parturition in rats was not affected by olanzapine and fluoxetine capsules. Olanzapine and fluoxetine capsules should be used during labor and delivery only if the potential benefit justifies the potential risk.

Olanzapine — The effect of olanzapine on labor and delivery in humans is unknown. Parturition in rats was not affected by olanzapine.

Fluoxetine — The effect of fluoxetine on labor and delivery in humans is unknown. Fluoxetine crosses the placenta; therefore, there is a possibility that fluoxetine may be associated with adverse effects on the newborn.

8.3 Nursing Mothers

Olanzapine and fluoxetine capsules — Studies evaluating the individual components of olanzapine and fluoxetine capsules (olanzapine and fluoxetine) in nursing mothers are described below. Because of the potential for serious adverse reactions in nursing infants from olanzapine and fluoxetine capsules, a decision should be made whether to discontinue nursing or to discontinue the drug, taking into account the importance of the drug to the mother. It is recommended that women not breast-feed when receiving olanzapine and fluoxetine capsules.

Olanzapine — In a study in lactating, healthy women, olanzapine was excreted in breast milk. Mean infant dose at steady state was estimated to be 1.8% of the maternal olanzapine dose. It is recommended that women receiving olanzapine should not breast-feed.

Fluoxetine — Fluoxetine is excreted in human breast milk. In 1 breast milk sample, the concentration of fluoxetine plus norfluoxetine was 70.4 ng/mL. The concentration in the mother’s plasma was 295.0 ng/mL. No adverse effects on the infant were reported. In another case, an infant nursed by a mother on fluoxetine developed crying, sleep disturbance, vomiting, and watery stools. The infant’s plasma drug levels were 340 ng/mL of fluoxetine and 208 ng/mL of norfluoxetine on the 2nd day of feeding.

8.4 Pediatric Use

Olanzapine and fluoxetine capsules — The safety and efficacy of olanzapine and fluoxetine capsules in patients 10 to 17 years of age has been established for the acute treatment of Depressive Episodes Associated with Bipolar I Disorder in a single 8 week randomized, placebo-controlled clinical trial (N = 255) [ see Clinical Studies (14.1) ]. Patients were initiated at a dose of 3/25 mg/day and force-titrated to the maximum dose of 12/50 mg/day over two weeks. After Week 2, there was flexible dosing of olanzapine and fluoxetine capsules in the range of 6/25, 6/50, 12/25, or 12/50 mg/day. The average dose was olanzapine 7.7 mg and fluoxetine 37.6 mg. The recommended starting dose for children and adolescents is 3/25 mg per day (lower than that for adults). Flexible dosing is recommended, rather than the forced titration used in the study [ see Dosage and Administration (2.1) ].

The types of adverse events observed with olanzapine and fluoxetine capsules in children and adolescents were generally similar to those observed in adults. However, the magnitude and frequency of some changes were greater in children and adolescents than adults. These included increases in lipids, hepatic enzymes, and prolactin, as well as increases in the QT interval [ see Warnings and Precautions (5.5, 5.20, 5.22), and Vital Signs and Laboratory Studies (6.2) ]. The frequency of weight gain ≥7%, and the magnitude and frequency of increases in lipids, hepatic analytes, and prolactin in children and adolescents treated with olanzapine and fluoxetine capsules were similar to those observed in adolescents treated with olanzapine monotherapy.

The safety and efficacy of olanzapine and fluoxetine in combination for the treatment of bipolar I depression in patients under the age of 10 years have not been established. The safety and effectiveness of olanzapine and fluoxetine in combination for treatment resistant depression in patients less than 18 years of age have not been established.

Anyone considering the use of olanzapine and fluoxetine capsules in a child or adolescent must balance the potential risks with the clinical need [ see Boxed Warning and Warnings and Precautions (5.1) ].

Olanzapine — Safety and effectiveness of olanzapine in children <13 years of age have not been established.

Compared to patients from adult clinical trials, adolescents treated with oral olanzapine were likely to gain more weight, experience increased sedation, and have greater increases in total cholesterol, triglycerides, LDL cholesterol, prolactin and hepatic aminotransferase levels.

Animal Data

Fluoxetine — Juvenile animal toxicity studies were performed for fluoxetine alone. Significant toxicity on muscle tissue, neurobehavior, reproductive organs, and bone development has been observed following exposure of juvenile rats to fluoxetine from weaning through maturity. Oral administration of fluoxetine to rats from weaning postnatal day 21 through adulthood day 90 at 3, 10, or 30 mg/kg/day was associated with testicular degeneration and necrosis, epididymal vacuolation and hypospermia (at 30 mg/kg/day corresponding to plasma exposures [AUC] approximately 5 to 10 times the average AUC in pediatric patients at the MRHD of 20 mg/day), increased serum levels of creatine kinase (at AUC as low as 1 to 2 times the average AUC in pediatric patients at the MRHD of 20 mg/day), skeletal muscle degeneration and necrosis, decreased femur length/growth and body weight gain (at AUC 5 to 10 times the average AUC in pediatric patients at the MRHD of 20 mg/day). The high dose of 30 mg/kg/day exceeded a maximum tolerated dose. When animals were evaluated after a drug-free period (up to 11 weeks after cessation of dosing), fluoxetine was associated with neurobehavioral abnormalities (decreased reactivity at AUC as low as approximately 0.1 to 0.2 times the average AUC in pediatric patients at the MRHD and learning deficit at the high dose), and reproductive functional impairment (decreased mating at all doses and impaired fertility at the high dose). In addition, the testicular and epididymal microscopic lesions and decreased sperm concentrations found in high dose group were also observed, indicating that the drug effects on reproductive organs are irreversible. The reversibility of fluoxetine-induced muscle damage was not assessed.

These fluoxetine toxicities in juvenile rats have not been observed in adult animals. Plasma exposures (AUC) to fluoxetine in juvenile rats receiving 3, 10, or 30 mg/kg/day doses in this study are approximately 0.1 to 0.2, 1 to 2, and 5 to 10 times, respectively, the average exposure in pediatric patients receiving the MRHD of 20 mg/day. Rat exposures to the major metabolite, norfluoxetine, are approximately 0.3 to 0.8, 1 to 8, and 3 to 20 times, respectively, the pediatric exposure at the MRHD.

A specific effect on bone development was reported in juvenile mice administered fluoxetine by the intraperitoneal route to 4 week old mice for 4 weeks at doses 0.5 and 2 times the oral MRHD of 20 mg/day on mg/m^2 basis. There was a decrease in bone mineralization and density at both doses, but the overall growth (body weight gain or femur length) was not affected.

8.5 Geriatric Use

Olanzapine and fluoxetine capsules — Clinical studies of olanzapine and fluoxetine capsules did not include sufficient numbers of patients ≥65 years of age to determine whether they respond differently from younger patients. Other reported clinical experience has not identified differences in responses between the elderly and younger patients. In general, dose selection for an elderly patient should be cautious, usually starting at the low end of the dosing range, reflecting the greater frequency of decreased hepatic, renal, or cardiac function, and of concomitant disease or other drug therapy [ see Dosage and Administration (2.3) ].

Olanzapine — Of the 2500 patients in premarketing clinical studies with olanzapine, 11% (263 patients) were ≥65 years of age. In patients with Schizophrenia, there was no indication of any different tolerability of olanzapine in the elderly compared with younger patients. Studies in patients with dementia-related psychosis have suggested that there may be a different tolerability profile in this population compared with younger patients with Schizophrenia. Elderly patients with dementia-related psychosis treated with olanzapine are at an increased risk of death compared to placebo. In placebo-controlled studies of olanzapine in elderly patients with dementia-related psychosis, there was a higher incidence of cerebrovascular adverse reactions (e.g., stroke, transient ischemic attack) in patients treated with olanzapine compared to patients treated with placebo. Olanzapine is not approved for the treatment of patients with dementia-related psychosis [ see Boxed Warning, Dosage and Administration (2.3), and Warnings and Precautions (5.2) ].

Also, the presence of factors that might decrease pharmacokinetic clearance or increase the pharmacodynamic response to olanzapine should lead to consideration of a lower starting dose for any geriatric patient.

Fluoxetine — U.S. fluoxetine clinical studies included 687 patients ≥65 years of age and 93 patients ≥75 years of age. No overall differences in safety or effectiveness were observed between these subjects and younger subjects, and other reported clinical experience has not identified differences in responses between the elderly and younger patients, but greater sensitivity of some older individuals cannot be ruled out. SNRIs and SSRIs, including olanzapine and fluoxetine capsules, have been associated with cases of clinically significant hyponatremia in elderly patients, who may be at greater risk for this adverse reaction [ see Warnings and Precautions (5.17)].

8.6 Hepatic Impairment

In subjects with cirrhosis of the liver, the clearances of fluoxetine and its active metabolite, norfluoxetine, were decreased, thus increasing the elimination half-lives of these substances. A lower or less frequent dose of the fluoxetine-component of olanzapine and fluoxetine capsules should be used in patients with cirrhosis. Caution is advised when using olanzapine and fluoxetine capsules in patients with diseases or conditions that could affect its metabolism [ see Dosage and Administration (2.3) and Clinical Pharmacology (12.4) ].

9 DRUG ABUSE AND DEPENDENCE

9.3 Dependence

Olanzapine and fluoxetine capsules, as with fluoxetine and olanzapine, have not been systematically studied in humans for their potential for abuse, tolerance, or physical dependence. While the clinical studies did not reveal any tendency for any drug-seeking behavior, these observations were not systematic, and it is not possible to predict on the basis of this limited experience the extent to which a CNS-active drug will be misused, diverted, and/or abused once marketed. Consequently, physicians should carefully evaluate patients for history of drug abuse and follow such patients closely, observing them for signs of misuse or abuse of olanzapine and fluoxetine capsules (e.g., development of tolerance, incrementation of dose, drug-seeking behavior).

In studies in rats and rhesus monkeys designed to assess abuse and dependence potential, olanzapine alone was shown to have acute depressive CNS effects but little or no potential of abuse or physical dependence at oral doses up to 15 (rat) and 8 (monkey) times the MRHD (20 mg) on a mg/m^2 basis.

10 OVERDOSAGE

Olanzapine and fluoxetine capsules — During premarketing clinical studies of olanzapine and fluoxetine in combination, overdose of both fluoxetine and olanzapine were reported in 5 study subjects. Four of the 5 subjects experienced loss of consciousness (3) or coma (1). No fatalities occurred.

Adverse reactions involving overdose of fluoxetine and olanzapine in combination, and olanzapine and fluoxetine capsules, have been reported. An overdose of combination therapy is defined as confirmed or suspected ingestion of a dose of >20 mg olanzapine in combination with a dose of >80 mg fluoxetine. Adverse reactions associated with these reports included somnolence (sedation), impaired consciousness (coma), impaired neurologic function (ataxia, confusion, convulsions, dysarthria), arrhythmias, lethargy, essential tremor, agitation, acute psychosis, hypotension, hypertension, and aggression. Fatalities have been confounded by exposure to additional substances including alcohol, thioridazine, oxycodone, and propoxyphene.

Olanzapine — In postmarketing reports of overdose with olanzapine alone, symptoms have been reported in the majority of cases. In symptomatic patients, symptoms with ≥10% incidence included agitation/aggressiveness, dysarthria, tachycardia, various extrapyramidal symptoms, and reduced level of consciousness ranging from sedation to coma. Among less commonly reported symptoms were the following potentially medically serious reactions: aspiration, cardiopulmonary arrest, cardiac arrhythmias (such as supraventricular tachycardia as well as a patient that experienced sinus pause with spontaneous resumption of normal rhythm), delirium, possible neuroleptic malignant syndrome, respiratory depression/arrest, convulsion, hypertension, and hypotension. Reports of fatality in association with overdose of olanzapine alone have been received. In 1 case of death, the amount of acutely ingested olanzapine was reported to be possibly as low as 450 mg of oral olanzapine; however, in another case, a patient was reported to survive an acute olanzapine ingestion of approximately 2 g of oral olanzapine.

Fluoxetine — Worldwide exposure to fluoxetine is estimated to be over 38 million patients (circa 1999). Of the 1578 cases of overdose involving fluoxetine, alone or with other drugs, reported from this population, there were 195 deaths.

Among 633 adult patients who overdosed on fluoxetine alone, 34 resulted in a fatal outcome, 378 completely recovered, and 15 patients experienced sequelae after overdose, including abnormal accommodation, abnormal gait, confusion, unresponsiveness, nervousness, pulmonary dysfunction, vertigo, tremor, elevated blood pressure, erectile dysfunction, movement disorder, and hypomania. The remaining 206 patients had an unknown outcome. The most common signs and symptoms associated with non-fatal overdose were seizures, somnolence, nausea, tachycardia, and vomiting. The largest known ingestion of fluoxetine in adult patients was 8 grams in a patient who took fluoxetine alone and who subsequently recovered. However, in an adult patient who took fluoxetine alone, an ingestion as low as 520 mg has been associated with lethal outcome, but causality has not been established.

Among pediatric patients (ages 3 months to 17 years), there were 156 cases of overdose involving fluoxetine alone or in combination with other drugs. Six patients died, 127 patients completely recovered, 1 patient experienced renal failure, and 22 patients had an unknown outcome. One of the 6 fatalities was a 9-year-old boy who had a history of OCD, Tourette’s Syndrome with tics, attention deficit disorder, and fetal alcohol syndrome. He had been receiving 100 mg of fluoxetine daily for 6 months in addition to clonidine, methylphenidate, and promethazine. Mixed-drug ingestion or other methods of suicide complicated all 6 overdoses in children that resulted in fatalities. The largest ingestion in pediatric patients was 3 grams, which was non-lethal.

Other important adverse reactions reported with fluoxetine overdose (single or multiple drugs) included coma, delirium, ECG abnormalities (such as nodal rhythm, QT-interval prolongation and ventricular arrhythmias, including torsade de pointes-type arrhythmias), hypotension, mania, neuroleptic malignant syndrome-like reactions, pyrexia, stupor, and syncope.

10.1 Management of Overdose

For current information on the management of olanzapine and fluoxetine capsules (olanzapine and fluoxetine) overdose, contact a certified poison control center (1-800-222-1222 or www.poison.org). In managing overdose, consider the possibility of multiple drug involvement. In case of acute overdose, establish and maintain an airway and ensure adequate ventilation, which may include intubation. Induction of emesis is not recommended as the possibility of obtundation, seizures, or dystonic reactions of the head and neck following overdose may create a risk for aspiration. Commence cardiovascular monitoring immediately and include continuous electrocardiographic monitoring to detect possible arrhythmias.

A specific precaution involves patients who are taking or have recently taken olanzapine and fluoxetine capsules and may have ingested excessive quantities of a TCA (tricyclic antidepressant). In such cases, accumulation of the parent TCA and/or an active metabolite increases the possibility of serious sequelae and extends the time needed for close medical observation.

Due to the large volume of distribution of olanzapine and fluoxetine, forced diuresis, dialysis, hemoperfusion, and exchange transfusion are unlikely to be of benefit. No specific antidote for either fluoxetine or olanzapine overdose is known. Treat hypotension and circulatory collapse with appropriate measures such as intravenous fluids and/or sympathomimetic agents. Do not use epinephrine, dopamine, or other sympathomimetics with β-agonist activity, since beta stimulation may worsen hypotension in the setting of olanzapine-induced alpha blockade.

11 DESCRIPTION

Olanzapine and Fluoxetine Capsules USP combine an atypical antipsychotic and a selective serotonin reuptake inhibitor, olanzapine, USP (the active ingredient in Zyprexa®, and Zyprexa® Zydis®) and fluoxetine hydrochloride, USP (the active ingredient in Prozac®, Prozac® Weekly™, and Sarafem®).

Olanzapine, USP belongs to the thienobenzodiazepine class. The chemical designation is 2-methyl-4-(4-methyl-1-piperazinyl)-10 H-thieno[2,3- b] [1,5]benzodiazepine.

Fluoxetine hydrochloride, USP is a selective serotonin reuptake inhibitor (SSRI). The chemical designation is (±)-N-methyl-3-phenyl-3-[(α,α,α-trifluoro- p-tolyl)oxy]propylamine hydrochloride.

The chemical structures are:

C17H20N4S M.W. 312.44

C17H18F3NO•HCl M.W. 345.79

Olanzapine, USP is a yellow crystalline solid, which is practically insoluble in water.

Fluoxetine hydrochloride, USP is a white to off-white crystalline solid with a solubility of 14 mg/mL in water.

Olanzapine and Fluoxetine Capsules USP are available for oral administration in the following strength combinations:

 | 3 mg/25 mg | 6 mg/25 mg | 6 mg/50 mg | 12 mg/25 mg | 12 mg/50 mg
Olanzapine, USP | 3 | 6 | 6 | 12 | 12
fluoxetine base equivalent | 25 | 25 | 50 | 25 | 50

Each capsule also contains D&C yellow #10 aluminum lake, FD&C blue #1 aluminum lake, FD&C blue #2 aluminum lake, FD&C red #40 aluminum lake, gelatin, iron oxide black, magnesium stearate, pregelatinized corn starch, propylene glycol, shellac glaze, and titanium dioxide. Additionally, the 3 mg/25 mg capsule contains D&C yellow #10 and FD&C yellow #6; both the 6 mg/25 mg and 12 mg/25 mg capsules contain ferric oxide yellow; the 6 mg/25 mg capsule contains ferric oxide red; and the 12 mg/50 mg capsule contains D&C red #28, FD&C blue #1, and FD&C red #40.

12 CLINICAL PHARMACOLOGY

12.1 Mechanism of Action

Although the exact mechanism of olanzapine and fluoxetine capsules is unknown, it has been proposed that the activation of 3 monoaminergic neural systems (serotonin, norepinephrine, and dopamine) is responsible for its enhanced antidepressant effect. In animal studies, olanzapine and fluoxetine in combination has been shown to produce synergistic increases in norepinephrine and dopamine release in the prefrontal cortex compared with either component alone, as well as increases in serotonin.

12.2 Pharmacodynamics

Olanzapine binds with high affinity to the following receptors: serotonin 5HT2A/2C, 5HT6 (Ki=4, 11, and 5 nM, respectively), dopamine D1-4 (Ki=11 to 31 nM), histamine H1 (Ki=7 nM), and adrenergic α1 receptors (Ki=19 nM). Olanzapine is an antagonist with moderate affinity binding for serotonin 5HT3 (Ki=57 nM) and muscarinic M1-5 (Ki=73, 96, 132, 32, and 48 nM, respectively). Olanzapine binds weakly to GABAA, BZD, and β-adrenergic receptors (Ki >10 μM). Fluoxetine is an inhibitor of the serotonin transporter and is a weak inhibitor of the norepinephrine and dopamine transporters.

Antagonism at receptors other than dopamine and 5HT2 may explain some of the other therapeutic and side effects of olanzapine. Olanzapine’s antagonism of muscarinic M1-5 receptors may explain its anticholinergic-like effects. The antagonism of histamine H1 receptors by olanzapine may explain the somnolence observed with this drug. The antagonism of α1-adrenergic receptors by olanzapine may explain the orthostatic hypotension observed with this drug. Fluoxetine has relatively low affinity for muscarinic, α1-adrenergic, and histamine H1 receptors.

12.3 Pharmacokinetics

Olanzapine and fluoxetine capsules — Fluoxetine (administered as a 60 mg single dose or 60 mg daily for 8 days) caused a small increase in the mean maximum concentration of olanzapine (16%) following a 5 mg dose, an increase in the mean area under the curve (17%) and a small decrease in mean apparent clearance of olanzapine (16%). In another study, a similar decrease in apparent clearance of olanzapine of 14% was observed following olanzapine doses of 6 or 12 mg with concomitant fluoxetine doses of 25 mg or more. The decrease in clearance reflects an increase in bioavailability. The terminal half-life is not affected, and therefore the time to reach steady state should not be altered. The overall steady-state plasma concentrations of olanzapine and fluoxetine when given as the combination in the therapeutic dose ranges were comparable with those typically attained with each of the monotherapies. The small change in olanzapine clearance, observed in both studies, likely reflects the inhibition of a minor metabolic pathway for olanzapine via CYP2D6 by fluoxetine, a potent CYP2D6 inhibitor, and was not deemed clinically significant. Therefore, the pharmacokinetics of the individual components is expected to reasonably characterize the overall pharmacokinetics of the combination.

Absorption and Bioavailability

Olanzapine and fluoxetine capsules — Following a single oral 12 mg/50 mg dose of olanzapine and fluoxetine capsules, peak plasma concentrations of olanzapine and fluoxetine occur at approximately 4 and 6 hours, respectively. The effect of food on the absorption and bioavailability of olanzapine and fluoxetine capsules has not been evaluated. The bioavailability of olanzapine given as Zyprexa®, and the bioavailability of fluoxetine given as Prozac® were not affected by food. It is unlikely that there would be a significant food effect on the bioavailability of olanzapine and fluoxetine capsules.

Olanzapine — Olanzapine is well absorbed and reaches peak concentration approximately 6 hours following an oral dose. Food does not affect the rate or extent of olanzapine absorption when olanzapine is given as Zyprexa®. It is eliminated extensively by first pass metabolism, with approximately 40% of the dose metabolized before reaching the systemic circulation.

Fluoxetine — Following a single oral 40 mg dose, peak plasma concentrations of fluoxetine from 15 to 55 ng/mL are observed after 6 to 8 hours. Food does not appear to affect the systemic bioavailability of fluoxetine given as Prozac®, although it may delay its absorption by 1 to 2 hours, which is probably not clinically significant.

Distribution

Olanzapine and fluoxetine capsules — The in vitro binding to human plasma proteins of olanzapine and fluoxetine in combination is similar to the binding of the individual components.

Olanzapine — Olanzapine is extensively distributed throughout the body, with a volume of distribution of approximately 1000 L. It is 93% bound to plasma proteins over the concentration range of 7 to 1100 ng/mL, binding primarily to albumin and α1-acid glycoprotein.

Fluoxetine — Over the concentration range from 200 to 1000 ng/mL, approximately 94.5% of fluoxetine is bound in vitro to human serum proteins, including albumin and α1-glycoprotein. The interaction between fluoxetine and other highly protein-bound drugs has not been fully evaluated [ see Drug Interactions (7.7) ].

Metabolism and Elimination

Olanzapine and fluoxetine capsules — Olanzapine and fluoxetine capsule therapy yielded steady-state concentrations of norfluoxetine similar to those seen with fluoxetine in the therapeutic dose range.

Olanzapine — Olanzapine displays linear pharmacokinetics over the clinical dosing range. Its half-life ranges from 21 to 54 hours (5th to 95th percentile; mean of 30 hr), and apparent plasma clearance ranges from 12 to 47 L/hr (5th to 95th percentile; mean of 25 L/hr). Administration of olanzapine once daily leads to steady-state concentrations in about 1 week that are approximately twice the concentrations after single doses. Plasma concentrations, half-life, and clearance of olanzapine may vary between individuals on the basis of smoking status, gender, and age [ see Dosage and Administration (2.3) and Clinical Pharmacology (12.4) ].

Following a single oral dose of^14C-labeled olanzapine, 7% of the dose of olanzapine was recovered in the urine as unchanged drug, indicating that olanzapine is highly metabolized. Approximately 57% and 30% of the dose was recovered in the urine and feces, respectively. In the plasma, olanzapine accounted for only 12% of the AUC for total radioactivity, indicating significant exposure to metabolites. After multiple dosing, the major circulating metabolites were the 10-N-glucuronide, present at steady state at 44% of the concentration of olanzapine, and 4´-N-desmethyl olanzapine, present at steady state at 31% of the concentration of olanzapine. Both metabolites lack pharmacological activity at the concentrations observed.

Direct glucuronidation and CYP450-mediated oxidation are the primary metabolic pathways for olanzapine. In vitro studies suggest that CYP1A2, CYP2D6, and the flavin-containing monooxygenase system are involved in olanzapine oxidation. CYP2D6-mediated oxidation appears to be a minor metabolic pathway in vivo, because the clearance of olanzapine is not reduced in subjects who are deficient in this enzyme.

Fluoxetine — Fluoxetine is a racemic mixture (50/50) of R-fluoxetine and S-fluoxetine enantiomers. In animal models, both enantiomers are specific and potent serotonin uptake inhibitors with essentially equivalent pharmacologic activity. The S-fluoxetine enantiomer is eliminated more slowly and is the predominant enantiomer present in plasma at steady state.

Fluoxetine is extensively metabolized in the liver to its only identified active metabolite, norfluoxetine, via the CYP2D6 pathway. A number of unidentified metabolites exist.

In animal models, S-norfluoxetine is a potent and selective inhibitor of serotonin uptake and has activity essentially equivalent to R- or S-fluoxetine. R-norfluoxetine is significantly less potent than the parent drug in the inhibition of serotonin uptake. The primary route of elimination appears to be hepatic metabolism to inactive metabolites excreted by the kidney.

Clinical Issues Related to Metabolism and Elimination

The complexity of the metabolism of fluoxetine has several consequences that may potentially affect the clinical use of olanzapine and fluoxetine capsules.

Variability in Metabolism — A subset (about 7%) of the population has reduced activity of the drug metabolizing enzyme CYP2D6. Such individuals are referred to as “poor metabolizers” of drugs such as debrisoquin, dextromethorphan, and the tricyclic antidepressants (TCAs). In a study involving labeled and unlabeled enantiomers administered as a racemate, these individuals metabolized S-fluoxetine at a slower rate and thus achieved higher concentrations of S-fluoxetine. Consequently, concentrations of S-norfluoxetine at steady state were lower. The metabolism of R-fluoxetine in these poor metabolizers appears normal. When compared with normal metabolizers, the total sum at steady state of the plasma concentrations of the 4 enantiomers was not significantly greater among poor metabolizers. Thus, the net pharmacodynamic activities were essentially the same. Alternative nonsaturable pathways (non-CYP2D6) also contribute to the metabolism of fluoxetine. This explains how fluoxetine achieves a steady-state concentration rather than increasing without limit.

Because the metabolism of fluoxetine, like that of a number of other compounds including TCAs and other selective serotonin antidepressants, involves the CYP2D6 system, concomitant therapy with drugs also metabolized by this enzyme system (such as the TCAs) may lead to drug interactions [ see Drug Interactions (7.7) ].

Accumulation and Slow Elimination — The relatively slow elimination of fluoxetine (elimination half-life of 1 to 3 days after acute administration and 4 to 6 days after chronic administration) and its active metabolite, norfluoxetine (elimination half-life of 4 to 16 days after acute and chronic administration), leads to significant accumulation of these active species in chronic use and delayed attainment of steady state, even when a fixed dose is used. After 30 days of dosing at 40 mg/day, plasma concentrations of fluoxetine in the range of 91 to 302 ng/mL and norfluoxetine in the range of 72 to 258 ng/mL have been observed. Plasma concentrations of fluoxetine were higher than those predicted by single-dose studies, because the metabolism of fluoxetine is not proportional to dose. However, norfluoxetine appears to have linear pharmacokinetics. Its mean terminal half-life after a single dose was 8.6 days and after multiple dosing was 9.3 days. Steady-state levels after prolonged dosing are similar to levels seen at 4 to 5 weeks.

The long elimination half-lives of fluoxetine and norfluoxetine assure that, even when dosing is stopped, active drug substance will persist in the body for weeks (primarily depending on individual patient characteristics, previous dosing regimen, and length of previous therapy at discontinuation). This is of potential consequence when drug discontinuation is required or when drugs are prescribed that might interact with fluoxetine and norfluoxetine following the discontinuation of fluoxetine.

12.4 Specific Populations

Geriatric — Based on the individual pharmacokinetic profiles of olanzapine and fluoxetine, the pharmacokinetics of olanzapine and fluoxetine capsules may be altered in geriatric patients. Caution should be used in dosing the elderly, especially if there are other factors that might additively influence drug metabolism and/or pharmacodynamic sensitivity.

In a study involving 24 healthy subjects, the mean elimination half-life of olanzapine was about 1.5 times greater in elderly subjects (≥65 years of age) than in non-elderly subjects (<65 years of age).

The disposition of single doses of fluoxetine in healthy elderly subjects (≥65 years of age) did not differ significantly from that in younger normal subjects. However, given the long half-life and nonlinear disposition of the drug, a single-dose study is not adequate to rule out the possibility of altered pharmacokinetics in the elderly, particularly if they have systemic illness or are receiving multiple drugs for concomitant diseases. The effects of age upon the metabolism of fluoxetine have been investigated in 260 elderly but otherwise healthy depressed patients (≥60 years of age) who received 20 mg fluoxetine for 6 weeks. Combined fluoxetine plus norfluoxetine plasma concentrations were 209.3 ± 85.7 ng/mL at the end of 6 weeks. No unusual age-associated pattern of adverse reactions was observed in those elderly patients.

Renal Impairment — The pharmacokinetics of olanzapine and fluoxetine capsules has not been studied in patients with renal impairment. However, olanzapine and fluoxetine individual pharmacokinetics do not differ significantly in patients with renal impairment. Olanzapine and fluoxetine capsule dosing adjustment based upon renal impairment is not routinely required.

Because olanzapine is highly metabolized before excretion and only 7% of the drug is excreted unchanged, renal dysfunction alone is unlikely to have a major impact on the pharmacokinetics of olanzapine. The pharmacokinetic characteristics of olanzapine were similar in patients with severe renal impairment and normal subjects, indicating that dosage adjustment based upon the degree of renal impairment is not required. In addition, olanzapine is not removed by dialysis. The effect of renal impairment on olanzapine metabolite elimination has not been studied.

In depressed patients on dialysis (N=12), fluoxetine administered as 20 mg once daily for 2 months produced steady-state fluoxetine and norfluoxetine plasma concentrations comparable with those seen in patients with normal renal function. While the possibility exists that renally excreted metabolites of fluoxetine may accumulate to higher levels in patients with severe renal dysfunction, use of a lower or less frequent dose is not routinely necessary in renally impaired patients.

Hepatic Impairment — Based on the individual pharmacokinetic profiles of olanzapine and fluoxetine, the pharmacokinetics of olanzapine and fluoxetine capsules may be altered in patients with hepatic impairment. The lowest starting dose should be considered for patients with hepatic impairment [ see Dosage and Administration (2.3) and Warnings and Precautions (5.20)].

Although the presence of hepatic impairment may be expected to reduce the clearance of olanzapine, a study of the effect of impaired liver function in subjects (N=6) with clinically significant cirrhosis (Child-Pugh Classification A and B) revealed little effect on the pharmacokinetics of olanzapine.

As might be predicted from its primary site of metabolism, liver impairment can affect the elimination of fluoxetine. The elimination half-life of fluoxetine was prolonged in a study of cirrhotic patients, with a mean of 7.6 days compared with the range of 2 to 3 days seen in subjects without liver disease; norfluoxetine elimination was also delayed, with a mean duration of 12 days for cirrhotic patients compared with the range of 7 to 9 days in normal subjects.

Gender — Clearance of olanzapine is approximately 30% lower in women than in men. There were, however, no apparent differences between men and women in effectiveness or adverse effects. Dosage modifications based on gender should not be needed.

Smoking Status — Olanzapine clearance is about 40% higher in smokers than in nonsmokers, although dosage modifications are not routinely required.

Race — No olanzapine and fluoxetine capsule pharmacokinetic study was conducted to investigate the effects of race. In vivo studies have shown that exposures to olanzapine are similar among Japanese, Chinese and Caucasians, especially after normalization for body weight differences. Dosage modifications for race, therefore, are not routinely required.

Combined Effects — The combined effects of age, smoking, and gender could lead to substantial pharmacokinetic differences in populations. The clearance of olanzapine in young smoking males, for example, may be 3 times higher than that in elderly nonsmoking females. Olanzapine and fluoxetine capsule dosing modification may be necessary in patients who exhibit a combination of factors that may result in slower metabolism of the olanzapine component [ see Dosage and Administration (2.3) ].

Children and Adolescents (ages 10 to 17 years) — Based on the pediatric olanzapine and fluoxetine capsule study, steady-state olanzapine, fluoxetine, and norfluoxetine plasma concentrations were about 31%, 76%, and 38% higher, respectively, in pediatric patients with lower body weights (less than 50 kg) than in pediatric patients with high body weight (greater than or equal to 50 kg). Exposures in pediatric patients with high body weight were similar to those previously observed in adults. Dose modifications based on body weight are not required.

13 NONCLINICAL TOXICOLOGY

13.1 Carcinogenesis, Mutagenesis, Impairment of Fertility

No carcinogenicity, mutagenicity, or fertility studies were conducted with olanzapine and fluoxetine capsules. The following data are based on findings in studies performed with the individual components, therefore all dose multiples (based on body surface area) reflect the maximum recommended human dose (MRHD) of 20 mg olanzapine, or 80 mg fluoxetine, when each drug is administered separately.

Carcinogenesis

Olanzapine — Oral carcinogenicity studies were conducted in mice and rats. Olanzapine was administered to mice in two 78 week studies at doses of 3, 10, and 30/20 mg/kg/day [equivalent to 0.8 to 5 times the maximum recommended human daily dose (MRHD) on a mg/m^2 basis] and 0.25, 2, and 8 mg/kg/day (equivalent to 0.06 to 2 times the MRHD on a mg/m^2 basis). Rats were dosed for 2 years at doses of 0.25, 1, 2.5, and 4 mg/kg/day (males) and 0.25, 1, 4, and 8 mg/kg/day (females) (equivalent to 0.1 to 2 and 0.1 to 4 times the MRHD on a mg/m^2 basis, respectively). The incidence of liver hemangiomas and hemangiosarcomas was significantly increased in 1 mouse study in females dosed at 8 mg/kg/day (2 times the MRHD on a mg/m^2 basis). These tumors were not increased in another mouse study in females dosed at 10 or 30/20 mg/kg/day (2 to 5 times the MRHD on a mg/m^2 basis); in this study, there was a high incidence of early mortalities in males of the 30/20 mg/kg/day group. The incidence of mammary gland adenomas and adenocarcinomas was significantly increased in female mice dosed at ≥2 mg/kg/day and in female rats dosed at ≥4 mg/kg/day (0.5 and 2 times the MRHD on a mg/m^2 basis, respectively). Antipsychotic drugs have been shown to chronically elevate prolactin levels in rodents. Serum prolactin levels were not measured during the olanzapine carcinogenicity studies; however, measurements during subchronic toxicity studies showed that olanzapine elevated serum prolactin levels up to 4-fold in rats at the same doses used in the carcinogenicity study. An increase in mammary gland neoplasms has been found in rodents after chronic administration of other antipsychotic drugs and is considered to be prolactin-mediated. The relevance for human risk of the finding of prolactin-mediated endocrine tumors in rodents is unknown [ see Warnings and Precautions (5.22)].

Fluoxetine — The dietary administration of fluoxetine to rats and mice for 2 years at doses of up to 10 and 12 mg/kg/day, respectively (approximately 1.2 and 0.7 times, respectively, the MRHD on a mg/m^2 basis), produced no evidence of carcinogenicity.

Mutagenesis

Olanzapine — No evidence of genotoxic potential for olanzapine was found in the Ames reverse mutation test, in vivo micronucleus test in mice, the chromosomal aberration test in Chinese hamster ovary cells, unscheduled DNA synthesis test in rat hepatocytes, induction of forward mutation test in mouse lymphoma cells, or in vivo sister chromatid exchange test in bone marrow of Chinese hamsters.

Fluoxetine — Fluoxetine and norfluoxetine have been shown to have no genotoxic effects based on the following assays: bacterial mutation assay, DNA repair assay in cultured rat hepatocytes, mouse lymphoma assay, and in vivo sister chromatid exchange assay in Chinese hamster bone marrow cells.

Impairment of Fertility

Olanzapine and fluoxetine capsules — Fertility studies were not conducted with olanzapine and fluoxetine capsules. However, in a repeat-dose rat toxicology study of 3 months duration, ovary weight was decreased in females treated with the low-dose [2 and 4 mg/kg/day (1 and 0.5 times the MRHD on a mg/m^2 basis), respectively] and high-dose [4 and 8 mg/kg/day (2 and 1 times the MRHD on a mg/m^2 basis), respectively] combinations of olanzapine and fluoxetine. Decreased ovary weight, and corpora luteal depletion and uterine atrophy were observed to a greater extent in the females receiving the high-dose combination than in females receiving either olanzapine or fluoxetine alone. In a 3 month repeat-dose dog toxicology study, reduced epididymal sperm and reduced testicular and prostate weights were observed with the high-dose combination of olanzapine and fluoxetine [5 and 5 mg/kg/day (9 and 2 times the MRHD on a mg/m^2 basis), respectively] and with olanzapine alone (5 mg/kg/day or 9 times the MRHD on a mg/m^2 basis).

Olanzapine — In an oral fertility and reproductive performance study in rats, male mating performance, but not fertility, was impaired at a dose of 22.4 mg/kg/day and female fertility was decreased at a dose of 3 mg/kg/day (11 and 1.5 times the MRHD on a mg/m^2 basis, respectively). Discontinuance of olanzapine treatment reversed the effects on male-mating performance. In female rats, the precoital period was increased and the mating index reduced at 5 mg/kg/day (2.5 times the MRHD on a mg/m^2 basis). Diestrous was prolonged and estrous was delayed at 1.1 mg/kg/day (0.6 times the MRHD on a mg/m^2 basis); therefore, olanzapine may produce a delay in ovulation.

Fluoxetine — Two fertility studies conducted in adult rats at doses of up to 7.5 and 12.5 mg/kg/day (approximately 0.9 and 1.5 times the MRHD on a mg/m^2 basis) indicated that fluoxetine had no adverse effects on fertility. However, adverse effects on fertility were seen when juvenile rats were treated with fluoxetine at a high dose (30 mg/kg) associated with significant toxicity [ see Use in Specific Populations (8.4) ].

14 CLINICAL STUDIES

Efficacy for olanzapine and fluoxetine capsules was established for the:

- Acute treatment of depressive episodes in Bipolar I Disorder in adults, and children and adolescents (10 to 17 years) in 3 short-term, placebo-controlled trials (Studies 1, 2, 3) [ see Clinical Studies (14.1) ].
- Acute and maintenance treatment of treatment resistant depression in adults (18 to 85 years) in 3 short-term, placebo-controlled trials (Studies 4, 5, 6) and 1 randomized withdrawal study with an active control (Study 7) [ see Clinical Studies (14.2) ].

14.1 Depressive Episodes Associated with Bipolar I Disorder

Adults — The efficacy of olanzapine and fluoxetine capsules for the acute treatment of depressive episodes associated with Bipolar I Disorder was established in 2 identically designed, 8 week, randomized, double-blind, controlled studies of patients who met Diagnostic and Statistical Manual 4th edition (DSM-IV) criteria for Bipolar I Disorder, Depressed utilizing flexible dosing of olanzapine and fluoxetine capsules (6/25, 6/50, or 12/50 mg/day), olanzapine (5 to 20 mg/day), and placebo. These studies included patients (≥18 years of age [n=788]) with or without psychotic symptoms and with or without a rapid cycling course.

The primary rating instrument used to assess depressive symptoms in these studies was the Montgomery-Asberg Depression Rating Scale (MADRS), a 10 item clinician-rated scale with total scores ranging from 0 to 60. The primary outcome measure of these studies was the change from baseline to endpoint in the MADRS total score. In both studies, olanzapine and fluoxetine capsules were statistically significantly superior to both olanzapine monotherapy and placebo in reduction of the MADRS total score. Refer to Table 18 (Studies 1 and 2).

Children and Adolescents — The efficacy of olanzapine and fluoxetine capsules for the acute treatment of depressive episodes associated with Bipolar I Disorder was established in a single 8 week, randomized, double-blind, placebo-controlled study of patients, 10 to 17 years of age [N=255], who met Diagnostic and Statistical Manual 4th edition-Text Revision (DSM-IV-TR) criteria for Bipolar I Disorder, Depressed. Patients were initiated at a dose of 3/25 mg/day and force-titrated to the maximum dose of 12/50 mg/day over two weeks. After Week 2, there was flexible dosing of olanzapine and fluoxetine capsules in the range of 6/25, 6/50, 12/25, or 12/50 mg/day. The average daily dose was olanzapine 7.7 mg and fluoxetine 37.6 mg. The recommended starting dose for children and adolescents is 3/25 mg per day. Flexible dosing is recommended, rather than the forced titration used in the study [ see Dosage and Administration (2.1) ]. This study included patients with or without psychotic symptoms.

The primary rating instrument used to assess depressive symptoms in these studies was the Children’s Depressive Rating Scale-Revised (CDRS-R), a 17-item clinician-rated scale with total scores ranging from 17 to 113. The primary outcome measure of this study was the change from baseline to Week 8 in the CDRS-R total score. In this study, olanzapine and fluoxetine capsules were statistically significantly superior to placebo in reduction of the CDRS-R total score. Refer to Table 18 (Study 3).

Table 18: Summary of the Primary Efficacy Result for Studies in Bipolar Depressiona
Study Number; (Primary Efficacy Measure) | Treatment group | Mean baseline score (SD) | LS mean change from baseline (SE) | Differenceb from Olanzapine and Fluoxetine (95% CI)
Study 1; (MADRS) | Olanzapine and fluoxetine | 29.9 (5.0) | -18.7 (1.8)
 | Olanzapine | 32.4 (6.3) | -14.4 (1.0) | -4.4 (NA)
 | Placebo | 31.2 (5.7) | -13.3 (1.0) | -5.5 (NA)
Study 2; (MADRS) | Olanzapine and fluoxetine | 31.7 (6.8) | -18.44 (1.7)
 | Olanzapine | 32.8 (6.1) | -15.81 (1.0) | -2.6 (NA)
 | Placebo | 31.4 (6.6) | -10.68 (1.0) | -7.8 (NA)
Study 3; (CDRS-R) | Olanzapine and fluoxetine | 54.6 (10.0) | -28.43 (1.1)
 | Placebo | 53.7 (8.2) | -23.40 (1.5) | -5.0 (-8.3, -1.8)

a SD – standard deviation; SE – standard error; LS mean – least-squares mean estimate; CI – unadjusted confidence interval; NA – not
available.

b Difference (olanzapine and fluoxetine capsules minus active comparator or placebo) in least squares estimates.

14.2 Treatment Resistant Depression

The efficacy of olanzapine and fluoxetine capsules in acute treatment resistant depression was demonstrated with data from 3 clinical studies (n=579) in adults (18 to 85 years). Doses evaluated in these studies ranged from 6 to 18 mg for olanzapine and 25 to 50 mg for fluoxetine.

An 8 week randomized, double-blind controlled study was conducted to evaluate the efficacy of olanzapine and fluoxetine capsules in patients (n=300) who met DSM-IV criteria for Major Depressive Disorder and did not respond to 2 different antidepressants after at least 6 weeks at or above the minimally effective labeled dosage in their current episode. Patients who were not responding to an antidepressant in their current episode entered an 8-week open-label fluoxetine lead-in; non-responders were randomized (1:1:1) to receive olanzapine and fluoxetine capsules, olanzapine, or fluoxetine, and were treated for 8 weeks. Olanzapine and fluoxetine capsules were flexibly dosed between 6/50 mg, 12/50 mg, and 18/50 mg. Results from this study yielded statistically significant greater reduction in mean total MADRS scores from baseline to endpoint for olanzapine and fluoxetine capsules versus fluoxetine and olanzapine. See Table 19 (Study 4). A second study with the same treatment-resistant patient population (n=28), when analyzed with change in MADRS as the outcome measure, demonstrated statistically significantly greater reduction in MADRS scores for olanzapine and fluoxetine capsules versus fluoxetine and olanzapine. See Table 19 (Study 5). A third study demonstrated statistically significantly greater reduction in total MADRS scores for olanzapine and fluoxetine capsules versus fluoxetine or olanzapine alone, when analyzed in a subpopulation of depressed patients (n=251) who met the definition of treatment resistance (patients who had not responded to 2 antidepressants of adequate dose and duration in the current episode). See Table 19 (Study 6).

Table 19: Summary of the Primary Efficacy Result for Studies in Treatment-Resistant Depressiona
Study Number (Primary Efficacy Measure | Treatment group | Mean baseline score (SD) | LS Mean change from baseline (SE) | Differenceb from Olanzapine and Fluoxetine (95% CI)
Study 4; (MADRS) | Olanzapine and fluoxetine; Olanzapine; Fluoxetine | 30.6 (6.1); 30.1 (6.3); 30.1 (5.9) | -14.1 (1.0); -7.1 (1.0); -8.3 (1.1) | -6.9 (NA); -5.8 (NA)
Study 5; (HAMD-21) | Olanzapine and fluoxetine; Olanzapine; Fluoxetine | 26.4 (7.5); 24.5 (5.2); 23.5 (6.0) | -11.7 (3.3); -5.9 (1.9); -3.8 (3.0) | -6.1 (-13.7, 1.5); -6.7 (-14.0, 0.5)
Study 6; (MADRS) | Olanzapine and fluoxetine; Olanzapine; Fluoxetine | 30.1 (6.6); 31.5 (6.8); 31.1 (5.6) | -13.3 (0.8); -8.8 (1.7); -10.0 (1.4) | NA; NA

a SD – standard deviation; SE – standard error; LS mean – least-squares mean estimate; CI – unadjusted confidence interval; NA – not available.

b Difference (olanzapine and fluoxetine capsules minus active comparator or placebo) in least squares estimates.

The efficacy of olanzapine and fluoxetine capsules in the maintenance therapy of treatment-resistant depression was demonstrated in a 47 week study (Study 7) in adults (18 to 65 years). Olanzapine and fluoxetine capsules was dosed between 6/25 mg, 12/25 mg, 6/50 mg, 12/50 mg, and 18/50 mg.

Patients (N=892) met DSM-IV criteria for Major Depressive Disorder and for treatment-resistant depression (a lack of response to 2 antidepressants after at least 6 weeks at or above the minimally effective labeled dose in their current episode of major depressive disorder). Patients were initially treated with open-label olanzapine and fluoxetine capsules; those who responded to and were stabilized on treatment over approximately 20 weeks were randomized to continue receiving treatment with olanzapine and fluoxetine capsules (n=221) or to receive treatment with fluoxetine (n=223) for another 27 weeks. Relapse was assessed using 3 criteria: a 50% increase in Montgomery-Åsberg Depression Rating Scale score from randomization with concomitant Clinical Global Impressions–Severity of Depression score increase to 4 or more; hospitalization due to depression or suicidality; or discontinuation due to lack of efficacy/worsening of depression/suicidality. A total of 15.8% of patients on olanzapine and fluoxetine capsules and 31.8% of patients on fluoxetine relapsed; this difference was statistically significant. Patients receiving continued olanzapine and fluoxetine capsules experienced statistically significantly longer time to relapse over the 27 weeks compared with those receiving fluoxetine (Figure 1).

16 HOW SUPPLIED/STORAGE AND HANDLING

16.1 How Supplied

Olanzapine and fluoxetine capsules USP are supplied as follows:

3 mg/25 mg strength: Capsules with opaque buff body and cap with "TEVA" imprinted on the cap and "5503" imprinted on the body, in bottles of 30. (NDC 42291-652-30)

6 mg/25 mg strength: Capsules with opaque orange body and cap with "TEVA" imprinted on the cap and "5504" imprinted on the body, in bottles of 30. (NDC 42291-653-30)

6 mg/50 mg strength: Capsules with opaque white body and cap with "TEVA" imprinted on the cap and "5505" imprinted on the body, in bottles of 30. (NDC 42291-654-30)

12 mg/25 mg strength: Capsules with opaque yellow body and cap with "TEVA" imprinted on the cap and "5506" imprinted on the body, in bottles of 30. (NDC 42291-655-30)

12 mg/50 mg strength: Capsules with opaque maroon body and cap with "TEVA" imprinted on the cap and "5507" imprinted on the body, in bottles of 30. (NDC 42291-656-30)

16.2 Storage and Handling

Store at 20° to 25°C (68° to 77°F) with excursions permitted between 15° to 30°C (59° to 86°F) [See USP Controlled Room Temperature]. Protect from light and moisture. Keep container tightly closed.

Dispense in a tight, light-resistant container as defined in the USP, with a child-resistant closure (as required).

17 PATIENT COUNSELING INFORMATION

See FDA-approved Medication Guide.

Patients should be advised of the following issues and asked to alert their prescriber if these occur while taking olanzapine and fluoxetine capsules.

17.1 Information on Medication Guide

Prescribers or other health professionals should inform patients, their families, and their caregivers about the potential benefits and potential risks associated with treatment with olanzapine and fluoxetine capsules and should counsel them in their appropriate use. A patient Medication Guide is available for olanzapine and fluoxetine capsules. The prescribers or other health professionals should instruct patients, their families, and their caregivers to read the Medication Guide and should assist them in understanding its contents. Patients should be given the opportunity to discuss the contents of the Medication Guide and to obtain answers to any questions they may have.

17.2 Suicidal Thoughts and Behaviors in Children, Adolescents, and Young Adults

Patients, their families, and their caregivers should be encouraged to be alert to the emergence of anxiety, agitation, panic attacks, insomnia, irritability, hostility, aggressiveness, impulsivity, akathisia (psychomotor restlessness), hypomania, mania, other unusual changes in behavior, worsening of depression, and suicidal ideation, especially early during antidepressant treatment and when the dose is adjusted up or down. Families and caregivers of patients should be advised to look for the emergence of such symptoms on a day-to-day basis, since changes may be abrupt. Such symptoms should be reported to the patient's prescriber or health professional, especially if they are severe, abrupt in onset, or were not part of the patient's presenting symptoms. Symptoms such as these may be associated with an increased risk for suicidal thinking and behavior and indicate a need for very close monitoring and possibly changes in the medication [ see Boxed Warning and Warnings and Precautions (5.1) ].

17.3 Elderly Patients with Dementia-Related Psychosis: Increased Mortality and Cerebrovascular Adverse Events (CVAE), Including Stroke

Patients and caregivers should be advised that elderly patients with dementia-related psychosis treated with antipsychotic drugs are at increased risk of death. Patients and caregivers should be advised that elderly patients with dementia-related psychosis treated with olanzapine had a significantly higher incidence of cerebrovascular adverse events (e.g., stroke, transient ischemic attack) compared with placebo. Olanzapine and fluoxetine capsules are not approved for elderly patients with dementia-related psychosis [ see Boxed Warning and Warnings and Precautions (5.2) ].

17.4 Neuroleptic Malignant Syndrome (NMS)

Patients and caregivers should be counseled that a potentially fatal symptom complex sometimes referred to as NMS has been reported in association with administration of antipsychotic drugs, including olanzapine, a component of olanzapine and fluoxetine capsules. Signs and symptoms of NMS include hyperpyrexia, muscle rigidity, altered mental status, and evidence of autonomic instability (irregular pulse or blood pressure, tachycardia, diaphoresis, and cardiac dysrhythmia) [ see Warnings and Precautions (5.3) ].

17.5 Drug Reaction with Eosinophilia and Systemic Symptoms (DRESS)

Patients should be advised to report to their health care provider at the earliest onset of any signs and symptoms that may be associated with Drug Reaction with Eosinophilia and Systemic Symptoms (DRESS) [ see Warnings and Precautions (5.4) ].

17.6 Hyperglycemia and Diabetes Mellitus

Patients should be advised of the potential risk of hyperglycemia-related adverse reactions. Patients should be monitored regularly for worsening of glucose control. Patients and caregivers should be counseled that metabolic changes have occurred during treatment with olanzapine and fluoxetine capsules. Patients who have diabetes should follow their doctor's instructions about how often to check their blood sugar while taking olanzapine and fluoxetine capsules [ see Warnings and Precautions (5.5) ].

17.7 Dyslipidemia

Patients should be counseled that dyslipidemia has occurred during treatment with olanzapine and fluoxetine capsules. Patients should have their lipid profile monitored regularly [ see Warnings and Precautions (5.5) ].

17.8 Weight Gain

Patients should be counseled that weight gain has occurred during treatment with olanzapine and fluoxetine capsules. Patients should have their weight monitored regularly [ see Warnings and Precautions (5.5) ].

17.9 Serotonin Syndrome

Patients should be cautioned about the risk of serotonin syndrome with the concomitant use of olanzapine and fluoxetine capsules and other serotonergic agents including triptans, tricyclic antidepressants, fentanyl, lithium, tramadol, tryptophan, buspirone, amphetamines, and St. John’s Wort [ see Contraindications (4.1) and Warnings and Precautions (5.6), and Drug Interactions (7.3) ]. Patients should be advised of the signs and symptoms associated with serotonin syndrome that may include mental status changes (e.g., agitation, hallucinations, delirium, and coma), autonomic instability (e.g., tachycardia, labile blood pressure, dizziness, diaphoresis, flushing, hyperthermia), neuromuscular changes (e.g., tremor, rigidity, myoclonus, hyperreflexia, incoordination), seizures, and/or gastrointestinal symptoms (e.g., nausea, vomiting, diarrhea). Patients should be cautioned to seek medical care immediately if they experience these symptoms.

17.10 Angle-Closure Glaucoma

Patients should be advised that taking olanzapine and fluoxetine capsules can cause mild pupillary dilation, which in susceptible individuals, can lead to an episode of angle-closure glaucoma. Pre-existing glaucoma is almost always open-angle glaucoma because angle-closure glaucoma, when diagnosed, can be treated definitively with iridectomy. Open-angle glaucoma is not a risk factor for angle-closure glaucoma. Patients may wish to be examined to determine whether they are susceptible to angle-closure, and have a prophylactic procedure (e.g., iridectomy), if they are susceptible [ see Warnings and Precautions (5.7) ].

17.11 Allergic Reactions and Rash

Patients should be advised to notify their physician if they develop a rash or hives [ see Warnings and Precautions (5.8) ]. Patients should also be advised of the signs and symptoms associated with a severe allergic reaction, including swelling of the face, eyes, or mouth, or have trouble breathing. Patients should be cautioned to seek medical care immediately if they experience these symptoms.

17.12 Orthostatic Hypotension

Patients should be advised of the risk of orthostatic hypotension, especially during the period of initial dose titration and in association with the use of concomitant drugs that may potentiate the orthostatic effect of olanzapine, e.g., diazepam or alcohol [ see Warnings and Precautions (5.11) and Drug Interactions (7.6, 7.7) ]. Patients should be advised to change positions carefully to help prevent orthostatic hypotension, and to lie down if they feel dizzy or faint, until they feel better. Patients should be advised to call their doctor if they experience any of the following signs and symptoms associated with orthostatic hypotension: dizziness, fast or slow heart beat, or fainting.

17.13 Abnormal Bleeding

Patients should be cautioned about the concomitant use of olanzapine and fluoxetine capsules and NSAIDs, aspirin, warfarin, or other drugs that affect coagulation since the combined use of psychotropic drugs that interfere with serotonin reuptake and these agents have been associated with an increased risk of bleeding [ see Warnings and Precautions (5.16)]. Patients should be advised to call their doctor if they experience any increased or unusual bruising or bleeding while taking olanzapine and fluoxetine capsules.

17.14 Hyponatremia

Patients should be advised that hyponatremia has been reported during treatment with SNRIs and SSRIs, including olanzapine and fluoxetine capsules. Signs and symptoms of hyponatremia include headache, difficulty concentrating, memory impairment, confusion, weakness, and unsteadiness, which may lead to falls. More severe and/or acute cases have been associated with hallucination, syncope, seizure, coma, respiratory arrest, and death [ see Warnings and Precautions (5.17)].

17.15 Potential for Cognitive and Motor Impairment

Olanzapine and fluoxetine capsules have the potential to impair judgment, thinking, or motor skills. Patients should be cautioned about operating hazardous machinery, including automobiles, until they are reasonably certain that olanzapine and fluoxetine capsule therapy does not affect them adversely [ see Warnings and Precautions (5.18)].

17.16 Body Temperature Dysregulation

Patients should be advised regarding appropriate care in avoiding overheating and dehydration. Patients should be advised to call their doctor right away if they become severely ill and have some or all of these symptoms of dehydration: sweating too much or not at all, dry mouth, feeling very hot, feeling thirsty, not able to produce urine [ see Warnings and Precautions (5.19)].

17.17 Concomitant Medication

Patients should be advised to inform their physician if they are taking Prozac®, Prozac® Weekly™, Sarafem®, fluoxetine, Zyprexa®, Zyprexa® Zydis® or Zyprexa® Relprevv. Patients should be advised to inform their physicians if they are taking, plan to take, or have stopped taking any prescription or over-the-counter drugs, including herbal supplements, since there is a potential for interactions. Patients should also be advised to inform their physicians if they plan to discontinue any medications they are taking while taking olanzapine and fluoxetine capsules, as stopping a medication may also impact the overall blood level of olanzapine and fluoxetine capsules [ see Warnings and Precautions (5.23)].

17.18 Discontinuation of Treatment with Olanzapine and Fluoxetine Capsules

Patients should be advised to take olanzapine and fluoxetine capsules exactly as prescribed, and to continue taking olanzapine and fluoxetine capsules as prescribed even after their mood symptoms improve. Patients should be advised that they should not alter their dosing regimen, or stop taking olanzapine and fluoxetine capsules, without consulting their physician [ see Warnings and Precautions (5.25)].

17.19 Alcohol

Patients should be advised to avoid alcohol while taking olanzapine and fluoxetine capsules [ see Drug Interactions (7.6, 7.7) ].

17.20 Use in Specific Populations

Pregnancy — Patients should be advised to notify their physician if they become pregnant or intend to become pregnant during olanzapine and fluoxetine capsule therapy. Olanzapine and fluoxetine capsules should be used during pregnancy only if the potential benefit justifies the potential risk to the fetus [ see Use in Specific Populations (8.1) ].

Nursing Mothers — Patients, if taking olanzapine and fluoxetine capsules, should be advised not to breast-feed [ see Use in Specific Populations (8.3) ].

Pediatric Use ― Safety and efficacy of olanzapine and fluoxetine capsules in patients 10 to 17 years of age have been established for the acute treatment of Depressive Episodes Associated with Bipolar I Disorder. The types of adverse reactions observed with olanzapine and fluoxetine capsules in children and adolescents were generally similar to those observed in adults. However, the magnitude and frequency of some changes were greater in children and adolescents than adults. These included increases in lipids, hepatic enzymes, and prolactin, as well as increases in the QT interval. Educate patients, families, and caregivers about these risks [ see Warnings and Precautions (5.5, 5.18, 5.20), Adverse Reactions (6.2), and Use in Specific Populations (8.4) ].

The frequency of weight gain ≥7%, and the magnitude and frequency of increases in lipids, hepatic analytes, and prolactin in children and adolescents treated with olanzapine and fluoxetine capsules were similar to those observed in adolescents treated with olanzapine monotherapy [ see Warnings and Precautions (5.5, 5.20), Adverse Reactions (6.2), and Use in Specific Populations (8.4) ].

The safety and effectiveness of olanzapine and fluoxetine capsules for the treatment of bipolar I depression in patients under 10 years of age have not been established. The safety and effectiveness of olanzapine and fluoxetine capsules for treatment resistant depression in patients under 18 years of age have not been established.

17.21 QT Prolongation

Patients should be advised that QT interval prolongation and ventricular arrhythmia including Torsade de Pointes have been reported in patients treated with fluoxetine. Signs and symptoms of ventricular arrhythmia include fast, slow, or irregular heart rate, dyspnea, syncope, or dizziness, which may indicate serious cardiac arrhythmia [see Warnings and Precautions (5.20)].

Brands listed are the trademarks of their respective owners.

Manufactured for:
AvKARE
Pulaski, TN 38478
Mfg. Rev. 03/25
AV Rev. 09/25(M)

Medication Guide

Olanzapine (oh-LAN-zah-peen) and Fluoxetine (floo-OX-eh-teen) Capsules

Read the Medication Guide that comes with olanzapine and fluoxetine capsules before you start taking them and each time you get a refill. There may be new information. This Medication Guide does not take the place of talking to your doctor about your medical condition or treatment. Talk with your doctor or pharmacist if there is something you do not understand or you want to learn more about olanzapine and fluoxetine capsules.

What is the most important information I should know about olanzapine and fluoxetine capsules?

Olanzapine and fluoxetine capsules may cause serious side effects, including:

1. Suicidal thoughts or actions.
2. Increased risk of death in elderly people who are confused, have memory loss and have lost touch with reality (dementia-related psychosis).
3. High blood sugar (hyperglycemia).
4. High fat levels in your blood (increased cholesterol and triglycerides), especially in children and adolescents age 10 to 17.
5. Weight gain, especially in children and adolescents age 10 to 17.

These serious side effects are described below.

1. Suicidal thoughts or actions.

Antidepressant medicines, depression and other serious mental illnesses, and suicidal thoughts or actions:

Talk to your, or your family member's, healthcare provider about:

- all risks and benefits of treatment with antidepressant medicines.
- all treatment choices for depression or other serious mental illness.

- Antidepressant medicines may increase suicidal thoughts or actions in some children, teenagers, and young adults within the first few months of treatment.
- Depression and other serious mental illnesses are the most important causes of suicidal thoughts and actions. Some people may have a particularly high risk of having suicidal thoughts or actions. These include people who have (or have a family history of) bipolar illness (also called manic-depressive illness) or suicidal thoughts or actions.
- How can I watch for and try to prevent suicidal thoughts and actions in myself or a family member?
  - Pay close attention to any changes, especially sudden changes, in mood, behaviors, thoughts, or feelings. This is very important when an antidepressant medicine is started or when the dose is changed.
  - Call the healthcare provider right away to report new or sudden changes in mood, behavior, thoughts, or feelings.
  - Keep all follow-up visits with the healthcare provider as scheduled. Call the healthcare provider between visits as needed, especially if you have concerns about symptoms.

Call a healthcare provider right away if you or your family member has any of the following symptoms, especially if they are new, worse, or worry you:

- thoughts about suicide or dying
- attempts to commit suicide
- new or worse depression
- new or worse anxiety
- feeling very agitated or restless
- panic attacks
- trouble sleeping (insomnia)
- new or worse irritability
- acting aggressive, being angry, or violent
- acting on dangerous impulses
- an extreme increase in activity and talking (mania)
- or other unusual changes in behavior or mood.

What else do I need to know about antidepressant medicines?

- Never stop an antidepressant medicine without first talking to a healthcare provider. Stopping an antidepressant medicine suddenly can cause other symptoms.
- Antidepressants are medicines used to treat depression and other illnesses. It is important to discuss all the risks of treating depression and also the risks of not treating it. Patients and their families or other caregivers should discuss all treatment choices with the healthcare provider, not just the use of antidepressants.
- Antidepressant medicines have other side effects. Talk to the healthcare provider about the side effects of the medicine prescribed for you or your family member.
- Antidepressant medicines can interact with other medicines. Know all of the medicines that you or your family member takes. Keep a list of all medicines to show the healthcare provider. Do not start new medicines without first checking with your healthcare provider.
- Not all antidepressant medicines prescribed for children are FDA approved for use in children. Talk to your child's healthcare provider for more information.

2. Increased risk of death in elderly people who are confused, have memory loss and have lost touch with reality (dementia-related psychosis). Olanzapine and fluoxetine capsules are not approved for treating psychosis in elderly people with dementia.

3. High blood sugar (hyperglycemia): High blood sugar can happen if you have diabetes already or if you have never had diabetes. High blood sugar could lead to:

- build up of acid in your blood due to ketones (ketoacidosis)
- coma
- death

Your doctor should do tests to check your blood sugar before you start taking olanzapine and fluoxetine capsules and during treatment. In people who do not have diabetes, sometimes high blood sugar goes away when olanzapine and fluoxetine capsules are stopped. People with diabetes and some people who did not have diabetes before taking olanzapine and fluoxetine capsules need to take medicine for high blood sugar even after they stop taking olanzapine and fluoxetine capsules.

If you have diabetes, follow your doctor's instructions about how often to check your blood sugar while taking olanzapine and fluoxetine capsules.

Call your doctor if you have any of these symptoms of high blood sugar (hyperglycemia) while taking olanzapine and fluoxetine capsules:

- feel very thirsty
- need to urinate more than usual
- feel very hungry
- feel weak or tired
- feel sick to your stomach
- feel confused, or your breath smells fruity.

4. High fat levels in your blood (increased cholesterol and triglycerides). High fat levels may happen in people treated with olanzapine and fluoxetine capsules, especially in children and adolescents (10 to 17 years old). You may not have any symptoms, so your doctor should do blood tests to check your cholesterol and triglyceride levels before you start taking olanzapine and fluoxetine capsules and during treatment.

5. Increase in weight (weight gain): Weight gain is common in people who take olanzapine and fluoxetine capsules. Children and adolescents (10 to 17 years old) who received olanzapine and fluoxetine capsules, were more likely to gain weight and to gain more weight than adults. Some people may gain a lot of weight while taking olanzapine and fluoxetine capsules, so you and your doctor should check your weight regularly. Talk to your doctor about ways to control weight gain, such as eating a healthy, balanced diet, and exercising.

What are olanzapine and fluoxetine capsules?

Olanzapine and fluoxetine capsules are a prescription medicine used for:

- short-term treatment of episodes of depression that happen with Bipolar I Disorder in people age 10 or older.
- treatment of episodes of depression that do not respond to 2 other medicines, also called treatment resistant depression, in adults.

Olanzapine and fluoxetine capsules contain two medicines, olanzapine and fluoxetine hydrochloride.

It is not known if olanzapine and fluoxetine capsules are safe and effective in children under the age of 10.

The symptoms of Bipolar I Disorder include alternating periods of depression and high or irritable mood, increased activity and restlessness, racing thoughts, talking fast, impulsive behavior, and a decreased need for sleep. With treatment, some of your symptoms of Bipolar I Disorder may improve.

The symptoms of treatment resistant depression include decreased mood, decreased interest, increased guilty feelings, decreased energy, decreased concentration, changes in appetite, and suicidal thoughts or behavior. With treatment, some of your symptoms of treatment resistant depression may improve.

If you do not think you are getting better, call your doctor.

Who should not take olanzapine and fluoxetine capsules?

- Do not take olanzapine and fluoxetine capsules if you take a Monoamine Oxidase Inhibitor (MAOI). Ask your healthcare provider or pharmacist if you are not sure if you take an MAOI, including the antibiotic linezolid.

- Do not take an MAOI within 5 weeks of stopping olanzapine and fluoxetine capsules unless directed to do so by your physician.
- Do not start olanzapine and fluoxetine capsules if you stopped taking an MAOI in the last 2 weeks unless directed to do so by your physician.

People who take olanzapine and fluoxetine capsules close in time to an MAOI can have serious and life-threatening side effects, with symptoms including:

- high fever
- continued muscle spasms that you cannot control
- rigid muscles
- changes in heart rate and blood pressure that happen fast
- confusion
- unconsciousness.

- Do not take olanzapine and fluoxetine capsules if you take Mellaril® (thioridazine). Do not take Mellaril® within 5 weeks of stopping olanzapine and fluoxetine capsules. Mellaril® can cause serious heart rhythm problems and you could die suddenly.
- Do not take olanzapine and fluoxetine capsules if you take the antipsychotic medicine pimozide (Orap®). Do not take pimozide (Orap®) within 5 weeks of stopping olanzapine and fluoxetine capsules.

What should I tell my doctor before taking olanzapine and fluoxetine capsules?

Olanzapine and fluoxetine capsules may not be right for you. Before starting olanzapine and fluoxetine capsules, tell your doctor about all your medical conditions, including if you have or had any of the following:

- heart problems
- seizures (convulsions)
- diabetes or high blood sugar levels (hyperglycemia)
- high cholesterol or triglyceride levels in your blood
- liver problems
- low or high blood pressure
- strokes or "mini-strokes" also called transient ischemic attacks (TIAs)
- bleeding problems
- Alzheimer's disease
- angle-closure glaucoma
- enlarged prostate in men
- bowel obstruction
- breast cancer
- are pregnant or plan to become pregnant. It is not known if olanzapine and fluoxetine capsules will harm your unborn baby.
- are breast-feeding or plan to breast-feed. Olanzapine and fluoxetine can pass into your breast milk and may harm your baby. You should not breast-feed while taking olanzapine and fluoxetine capsules. Talk to your doctor about the best way to feed your baby if you take olanzapine and fluoxetine capsules.

Before starting olanzapine and fluoxetine capsules, tell your doctor about all the medicines that you take, including

- Prescription and non-prescription medicines
- Vitamins, and herbal supplements
- Triptans used to treat migraine headache
- Medicines used to treat mood, anxiety, psychotic or thought disorders, including tricyclics, lithium, buspirone, SSRIs, SNRIs, MAOIs, or antipsychotics
- Tramadol and fentanyl
- Amphetamines
- Over-the-counter supplements such as tryptophan or St. John’s Wort
- Electroconvulsive therapy (ECT)

Olanzapine and fluoxetine capsules and some medicines may interact with each other and may not work as well, or cause possible serious side effects. Your doctor can tell you if it is safe to take olanzapine and fluoxetine capsules with your other medicines. Do not start or stop any medicine while taking olanzapine and fluoxetine capsules without talking to your doctor first.

If you take olanzapine and fluoxetine capsules, you should not take any other medicines that contain:

- olanzapine (the active ingredient in Zyprexa® and Zyprexa® Zydis®) or
- fluoxetine hydrochloride (the active ingredient in Prozac®, Prozac® Weekly™, and Sarafem®).

You could take too much medicine (overdose).

How should I take olanzapine and fluoxetine capsules?

- Take olanzapine and fluoxetine capsules exactly as prescribed. Your doctor may need to change (adjust) the dose of olanzapine and fluoxetine capsules until it is right for you.
- If you miss a dose of olanzapine and fluoxetine capsules, take the missed dose as soon as you remember. If it is almost time for the next dose, skip the missed dose and take your next dose at the regular time. Do not take two doses of olanzapine and fluoxetine capsules at the same time.
- To prevent serious side effects, do not stop taking olanzapine and fluoxetine capsules suddenly. If you need to stop taking olanzapine and fluoxetine capsules, your doctor can tell you how to safely stop taking them.
- If you take too many olanzapine and fluoxetine capsules, call your doctor or poison control center right away, or get emergency treatment.
- Olanzapine and fluoxetine capsules can be taken with or without food.
- Olanzapine and fluoxetine capsules are usually taken one time each day, in the evening.
- If you do not think you are getting better or have any concerns about your condition while taking olanzapine and fluoxetine capsules, call your doctor.

What should I avoid while taking olanzapine and fluoxetine capsules?

- Olanzapine and fluoxetine capsules can cause sleepiness and may affect your ability to make decisions, think clearly, or react quickly. You should not drive, operate heavy machinery, or do other dangerous activities until you know how olanzapine and fluoxetine capsules affect you.
- Avoid drinking alcohol while taking olanzapine and fluoxetine capsules. Drinking alcohol while you take olanzapine and fluoxetine capsules may make you sleepier than if you take olanzapine and fluoxetine capsules alone.

What are the possible side effects of olanzapine and fluoxetine capsules?

Other possible serious risks:

- Increased risk of death and increased incidence of stroke or "mini-strokes" called transient ischemic attacks (TIAs) in elderly people with psychosis related to dementia (a brain disorder that lessens the ability to remember, think, and reason). Olanzapine and fluoxetine capsules are not approved for these patients.
- Severe allergic reactions: Tell your doctor right away if you get red itchy welts (hives) or, a rash alone or with fever and joint pain, while taking olanzapine and fluoxetine capsules. Call your doctor right away if you become severely ill and have some or all of these symptoms:

- swelling of your face, eyes, or mouth
- trouble breathing

- Neuroleptic malignant syndrome (NMS): NMS is a rare but very serious condition that can happen in people who take antipsychotic medicines, including olanzapine and fluoxetine capsules. NMS can cause death and must be treated in a hospital. Call your doctor right away if you become severely ill and have some or all of these symptoms:
  - high fever
  - excessive sweating
  - rigid muscles
  - confusion
  - changes in your breathing, heartbeat, and blood pressure
- Drug Reaction with Eosinophilia and Systemic Symptoms (DRESS): DRESS can occur. Features of DRESS may include rash, fever, swollen glands and other internal organ involvement such as liver, kidney, lung and heart. DRESS is sometimes fatal; therefore, tell your doctor immediately if you experience any of these signs.
- Tardive Dyskinesia: This condition causes body movements that keep happening and that you cannot control. These movements usually affect the face and tongue. Tardive dyskinesia may not go away, even if you stop taking olanzapine and fluoxetine capsules. It may also start after you stop taking olanzapine and fluoxetine capsules. Tell your doctor if you get any body movements that you cannot control.
- Serotonin Syndrome: This is a condition that can be life threatening. Call your doctor right away if you become severely ill and have some or all of these symptoms:
  - agitation, hallucinations, coma or other changes in mental status
  - coordination problems or muscle twitching (overactive reflexes)
  - racing heartbeat, high or low blood pressure
  - sweating or fever
  - nausea, vomiting, and diarrhea
  - muscle rigidity
  - dizziness
  - flushing
  - tremor
  - seizures
- Visual problems:
  - eye pain
  - changes in vision
  - swelling or redness in or around the eye
  Only some people are at risk for these problems. You may want to undergo an eye examination to see if you are at risk and receive preventative treatment if you are.
- Abnormal bleeding: Tell your doctor if you notice any increased or unusual bruising or bleeding while taking olanzapine and fluoxetine capsules, especially if you take one of these medicines:
  - the blood thinner warfarin (Coumadin®, Jantoven®)
  - a non-steroidal anti-inflammatory drug (NSAID)
  - aspirin
- Low salt (sodium) levels in the blood (hyponatremia): Call your doctor right away if you become severely ill and have some or all of these symptoms:
  - headache
  - feel weak
  - confusion
  - problems concentrating
  - memory problems
  - feel unsteady
- Changes in the electrical activity of your heart (QT prolongation and ventricular arrhythmia including torsade de pointes). This condition can be life threatening. The symptoms may include:
  - fast, slow, or irregular heartbeat
  - shortness of breath
  - dizziness or fainting
- Decreased blood pressure when you change positions, with symptoms of dizziness, fast or slow heart beat, or fainting
- Difficulty swallowing
- Seizures
- Problems with control of body temperature: You could become very hot, for instance when you exercise a lot or stay in an area that is very hot. It is important for you to drink water to avoid dehydration. Call your doctor right away if you become severely ill and have some or all of these symptoms of dehydration:
  - sweating too much or not at all
  - dry mouth
  - feeling very hot
  - feeling thirsty
  - not able to produce urine

Common possible side effects of olanzapine and fluoxetine capsules include: dry mouth, tiredness, sleeping for long period of time, increased appetite, swelling of your hands and feet, drowsiness, tremors (shakes), or blurred vision.

Tell your doctor about any side effect that bothers you or that does not go away.

These are not all the possible side effects with olanzapine and fluoxetine capsules. For more information, ask your doctor or pharmacist.

Call your doctor for medical advice about side effects. You may report side effects to FDA at 1-800-FDA-1088.

How should I store olanzapine and fluoxetine capsules?

- Store olanzapine and fluoxetine capsules at room temperature, between 68°F to 77°F (20°C to 25°C).
- Keep olanzapine and fluoxetine capsules away from light.
- Keep olanzapine and fluoxetine capsules dry and away from moisture. Keep the bottle closed tightly.

Keep olanzapine and fluoxetine capsules and all medicines out of the reach of children.

General information about olanzapine and fluoxetine capsules

Medicines are sometimes prescribed for purposes other than those listed in a Medication Guide. Do not use olanzapine and fluoxetine capsules for a condition for which they were not prescribed. Do not give olanzapine and fluoxetine capsules to other people, even if they have the same condition. They may harm them.

This Medication Guide summarizes the most important information about olanzapine and fluoxetine capsules. If you would like more information, talk with your doctor. You can ask your doctor or pharmacist for information about olanzapine and fluoxetine capsules that was written for healthcare professionals. For more information about olanzapine and fluoxetine capsules call 1-855-361-3993.

What are the ingredients in olanzapine and fluoxetine capsules?

Active ingredients: olanzapine and fluoxetine hydrochloride

Inactive ingredients: D&C yellow #10 aluminum lake, FD&C blue #1 aluminum lake, FD&C blue #2 aluminum lake, FD&C red #40 aluminum lake, gelatin, iron oxide black, magnesium stearate, pregelatinized corn starch, propylene glycol, shellac glaze, and titanium dioxide. Additionally, the 3 mg/25 mg capsule contains D&C yellow #10 and FD&C yellow #6; both the 6 mg/25 mg and 12 mg/25 mg capsules contain ferric oxide yellow; the 6 mg/25 mg capsule contains ferric oxide red; and the 12 mg/50 mg capsule contains D&C red #28, FD&C blue #1, and FD&C red #40.

Brands listed are the trademarks of their respective owners.
This Medication Guide has been approved by the U.S. Food and Drug Administration.
Manufactured for:
AvKARE
Pulaski, TN38478
Mfg. Rev. 03/25
AV Rev. 09/25 (M)